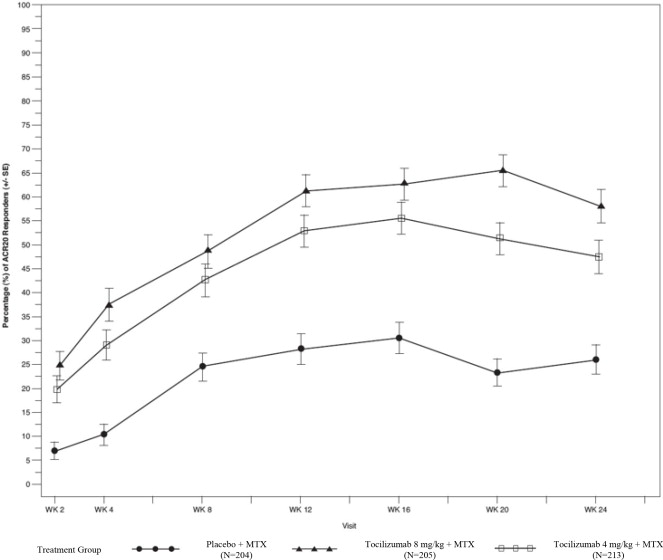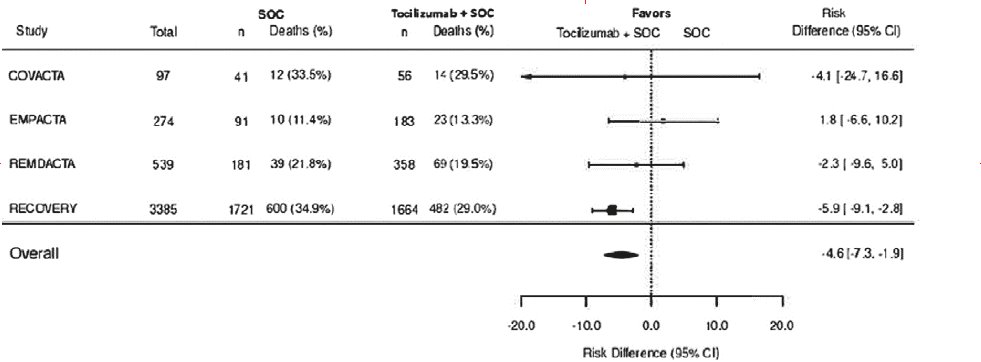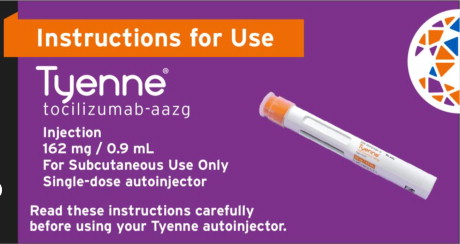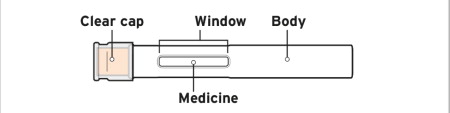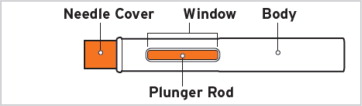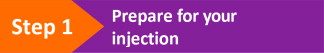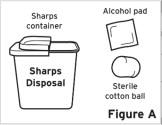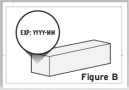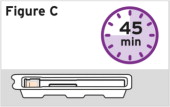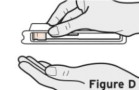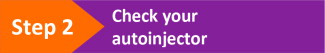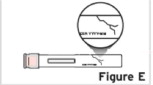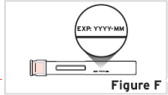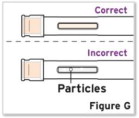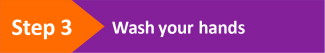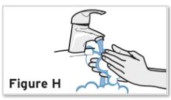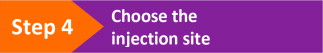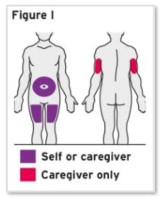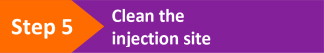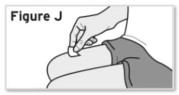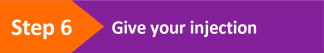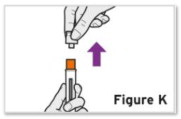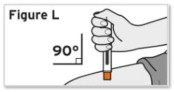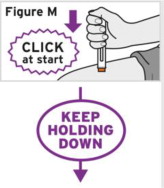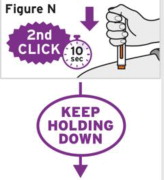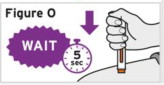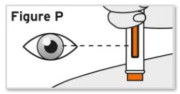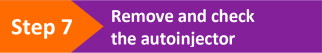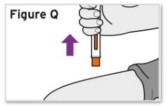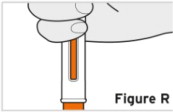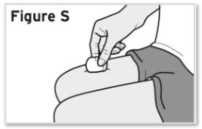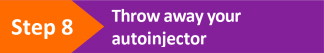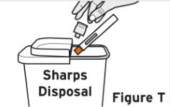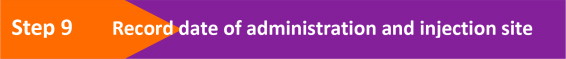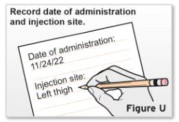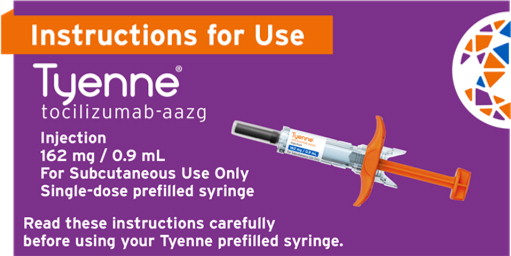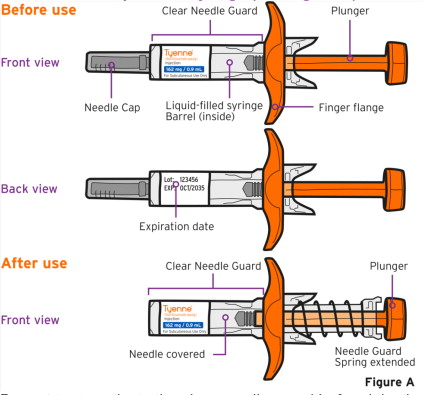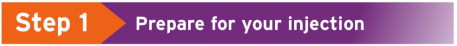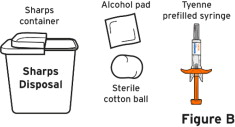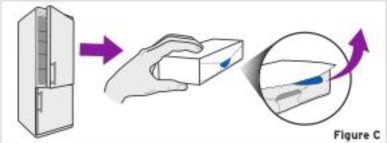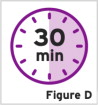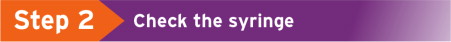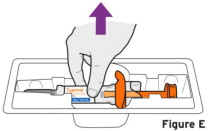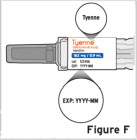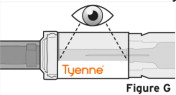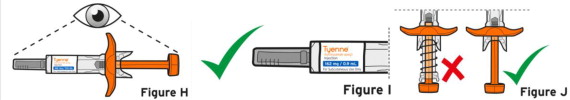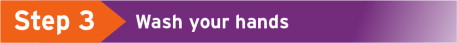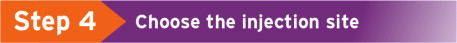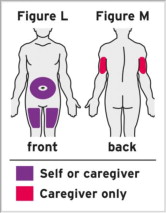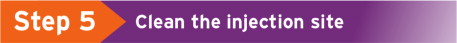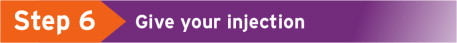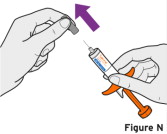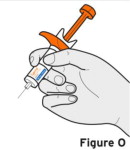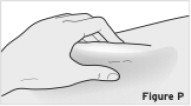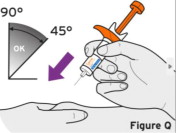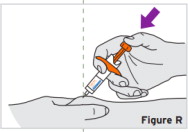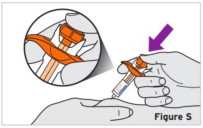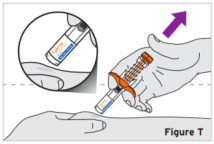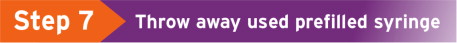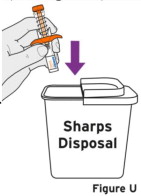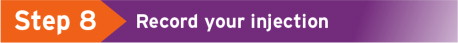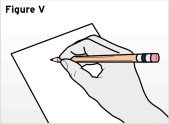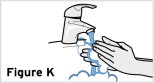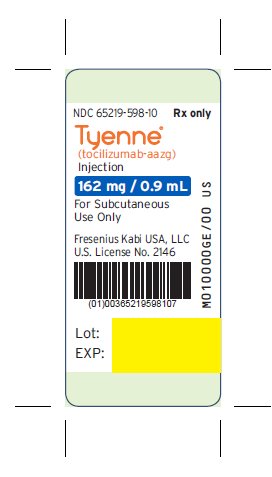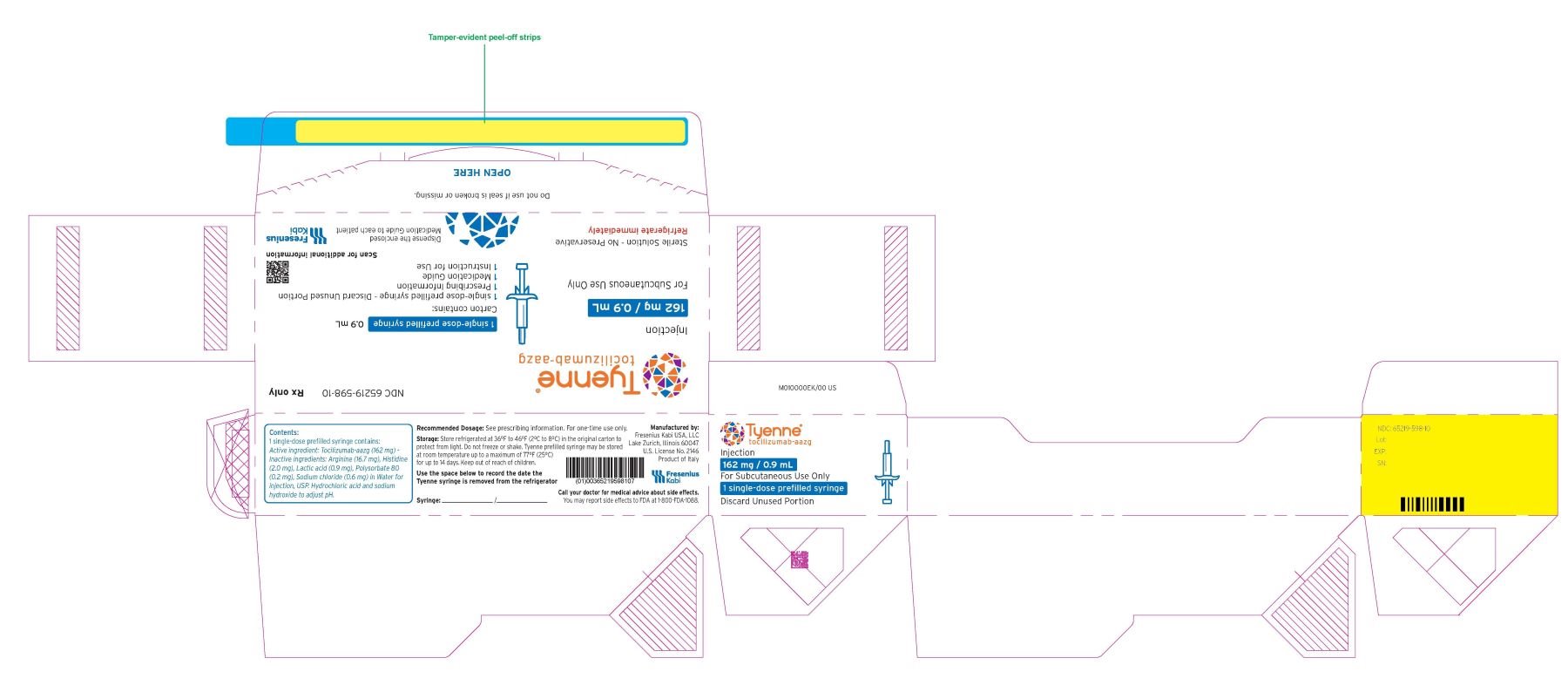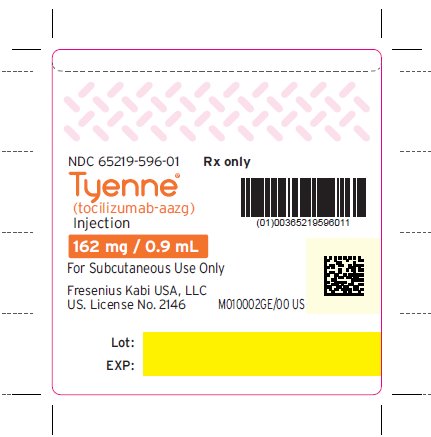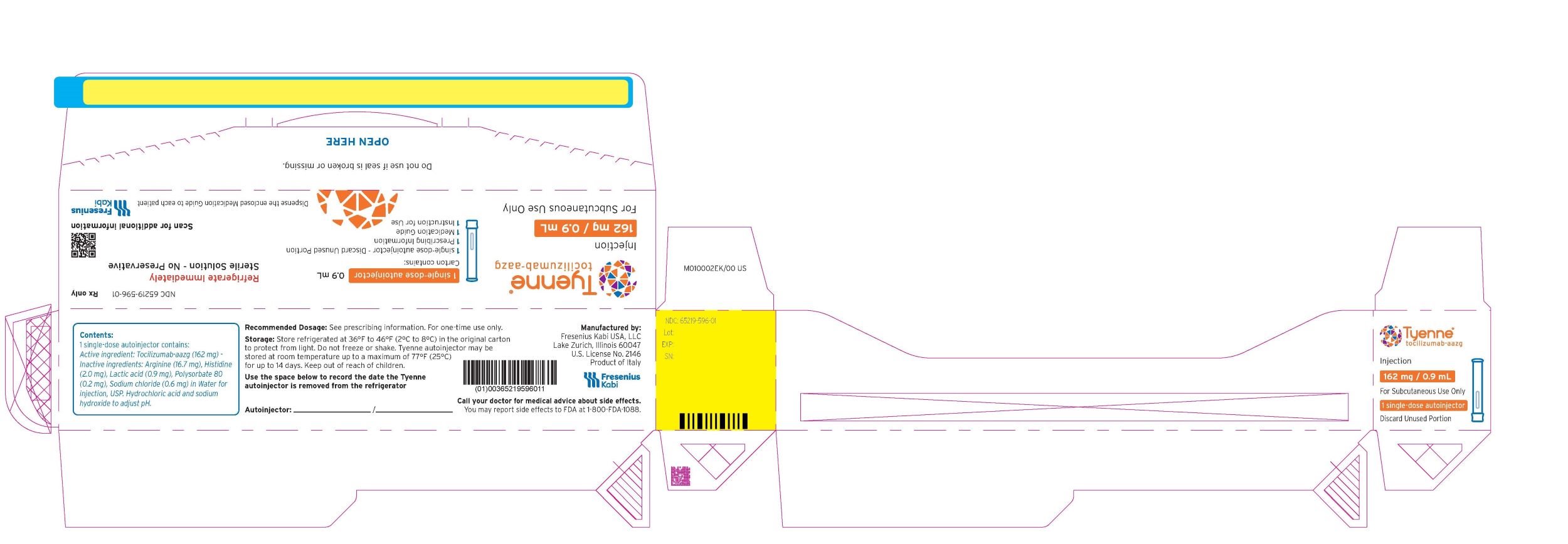 DRUG LABEL: TYENNE
NDC: 65219-598 | Form: INJECTION, SOLUTION
Manufacturer: Fresenius Kabi USA, LLC
Category: prescription | Type: HUMAN PRESCRIPTION DRUG LABEL
Date: 20250826

ACTIVE INGREDIENTS: TOCILIZUMAB 162 mg/0.9 mL
INACTIVE INGREDIENTS: Arginine; Histidine; Lactic acid, L-; Polysorbate 80; Sodium chloride; Water; Hydrochloric acid; Sodium hydroxide

HIGHLIGHTS OF PRESCRIBING INFORMATION

These highlights do not include all the information needed to use TYENNE safely and effectively. See full prescribing information for TYENNE.
TYENNE® (tocilizumab-aazg) injection, for intravenous or subcutaneous use
Initial U.S. Approval: 2024
TYENNE® (tocilizumab-aazg) is biosimilar [Biosimilar means that the biological product is approved based on data demonstrating that it is highly similar to an FDA-approved biological product, known as a reference product, and that there are no clinically meaningful differences between the biosimilar product and the reference product. Biosimilarity of TYENNE has been demonstrated for the condition(s) of use (e.g., indication(s), dosing regimen(s), strength(s), dosage form(s), and route(s) of administration) described in its Full Prescribing Information.] to ACTEMRA® (tocilizumab).

RECENT MAJOR CHANGES

Indications and Usage (1.5, 1.6) 02/2025

Dosage and Administration (2.1, 2.6, 2.7) 02/2025

Warnings and Precautions (5.1, 5.3, 5.4) 02/2025

Warnings and Precautions (5.6) 12/2024

WARNING: RISK OF SERIOUS INFECTIONS

See full prescribing information for complete boxed warning.

- Serious infections leading to hospitalization or death including tuberculosis (TB), bacterial, invasive fungal, viral, and other opportunistic infections have occurred in patients receiving tocilizumab products. (5.1)
- If a serious infection develops, interrupt TYENNE until the infection is controlled. (5.1)
- Perform test for latent TB (except patients with COVID-19); if positive, start treatment for TB prior to starting TYENNE. (5.1)
- Monitor all patients for active TB during treatment, even if initial latent TB test is negative. (5.1)

1 INDICATIONS AND USAGE

TYENNE® (tocilizumab-aazg) is an interleukin-6 (IL-6) receptor antagonist indicated for treatment of:

Rheumatoid Arthritis (RA) (1.1)

- Adult patients with moderately to severely active rheumatoid arthritis who have had an inadequate response to one or more Disease-Modifying Anti-Rheumatic Drugs (DMARDs).

Giant Cell Arteritis (GCA) (1.2)

- Adult patients with giant cell arteritis.

Polyarticular Juvenile Idiopathic Arthritis (PJIA) (1.3)

- Patients 2 years of age and older with active polyarticular juvenile idiopathic arthritis.

Systemic Juvenile Idiopathic Arthritis (SJIA) (1.4)

- Patients 2 years of age and older with active systemic juvenile idiopathic arthritis.

Cytokine Release Syndrome (CRS) (1.5)

- Adults and pediatric patients 2 years of age and older with chimeric antigen receptor (CAR) T cell-induced severe or life-threatening cytokine release syndrome.

Coronavirus Disease 2019 (COVID-19) (1.6)

- Hospitalized adult patients with coronavirus disease 2019 (COVID-19) who are receiving systemic corticosteroids and require supplemental oxygen, non-invasive or invasive mechanical ventilation, or extracorporeal membrane oxygenation (ECMO).

2 DOSAGE AND ADMINISTRATION

For RA, pJIA and sJIA, TYENNE may be used alone or in combination with methotrexate; and in RA, other non-biologic DMARDs may be used. (2)

General Administration and Dosing Information (2.1)

- RA, GCA, PJIA and SJIA – It is recommended that TYENNE not be initiated in patients with an absolute neutrophil count (ANC) below 2,000 per mm^3, platelet count below 100,000 per mm^3, or ALT or AST above 1.5 times the upper limit of normal (ULN) (5.3, 5.4).
- COVID-19 – It is recommended that TYENNE not be initiated in patients with an absolute neutrophil count (ANC) below 1,000 per mm^3, platelet count below 50,000 mm^3, or ALT or AST above 10 times ULN (5.3, 5.4).
- In RA, CRS or COVID-19 patients, TYENNE doses exceeding 800 mg per infusion are not recommended. (2.2, 2.9, 12.3)
- In GCA patients, TYENNE doses exceeding 600 mg per infusion are not recommended. (2.3, 12.3)

Rheumatoid Arthritis (2.2)

Recommended Adult Intravenous Dosage:

When used in combination with non-biologic DMARDs or as monotherapy the recommended starting dose is 4 mg per kg every 4 weeks followed by an increase to 8 mg per kg every 4 weeks based on clinical response.

Recommended Adult Subcutaneous Dosage:

Patients less than 100 kg weight | 162 mg administered subcutaneously every other week, followed by an increase to every week based on clinical response
Patients at or above 100 kg weight | 162 mg administered subcutaneously every week

Giant Cell Arteritis (2.3)

Recommended Adult Intravenous Dosage: The recommended dose is 6 mg per kg every 4 weeks in combination with a tapering course of glucocorticoids. TYENNE can be used alone following discontinuation of glucocorticoids.

Recommended Adult Subcutaneous Dosage: The recommended dose is 162 mg given once every week as a subcutaneous injection, in combination with a tapering course of glucocorticoids.

A dose of 162 mg given once every other week as a subcutaneous injection, in combination with a tapering course of glucocorticoids, may be prescribed based on clinical considerations.

TYENNE can be used alone following discontinuation of glucocorticoids.

Polyarticular Juvenile Idiopathic Arthritis (2.4)

Recommended Intravenous PJIA Dosage Every 4 Weeks
Patients less than 30 kg weight | 10 mg per kg
Patients at or above 30 kg weight | 8 mg per kg

Recommended Subcutaneous PJIA Dosage
Patients less than 30 kg weight | 162 mg once every three weeks
Patients at or above 30 kg weight | 162 mg once every two weeks

Systemic Juvenile Idiopathic Arthritis (2.5)

Recommended Intravenous SJIA Dosage Every 2 Weeks
Patients less than 30 kg weight | 12 mg per kg
Patients at or above 30 kg weight | 8 mg per kg

Recommended Subcutaneous SJIA Dosage
Patients less than 30 kg weight | 162 mg every two weeks
Patients at or above 30 kg weight | 162 mg every week

Cytokine Release Syndrome (2.6)

Recommended Intravenous CRS Dosage
Patients less than 30 kg weight | 12 mg per kg
Patients at or above 30 kg weight | 8 mg per kg
Alone or in combination with corticosteroids.

Coronavirus Disease 2019 (2.7)

The recommended dosage of TYENNE for adult patients with COVID-19 is 8 mg per kg administered by a 60-minute intravenous infusion.

Administration of Intravenous formulation (2.8)

- For patients with RA, GCA, COVID-19, CRS, PJIA, SJIA patients at or above 30 kg, dilute to 100 mL in 0.9% or 0.45% Sodium Chloride Injection, USP for intravenous infusion using aseptic technique.
- For PJIA, SJIA and CRS patients less than 30 kg, dilute to 50 mL in 0.9% or 0.45% Sodium Chloride Injection, USP for intravenous infusion using aseptic technique.
- Administer as a single intravenous drip infusion over 1 hour; do not administer as bolus or push.

Administration of Subcutaneous formulation (2.9)

- Follow the Instructions for Use for prefilled syringe and prefilled autoinjector

Dose Modifications (2.10)

Recommended for management of certain dose-related laboratory changes including elevated liver enzymes, neutropenia, and thrombocytopenia.

3 DOSAGE FORMS AND STRENGTHS

Intravenous Infusion

Injection: 80 mg/4 mL (20 mg/mL), 200 mg/10 mL (20 mg/mL), 400 mg/20 mL (20 mg/mL) in single-dose vials for further dilution prior to intravenous infusion (3)

Subcutaneous Injection

Injection: 162 mg/0.9 mL in a single-dose prefilled syringe or single-dose prefilled autoinjector (3)

4 CONTRAINDICATIONS

Known hypersensitivity to tocilizumab products. (4)

5 WARNINGS AND PRECAUTIONS

- Serious Infections – do not administer TYENNE during an active infection, including localized infections. If a serious infection develops, interrupt TYENNE until the infection is controlled. (5.1)
- Gastrointestinal (GI) perforation-use with caution in patients who may be at increased risk. (5.2)
- Hepatotoxicity- Monitor patients for signs and symptoms of hepatic injury. Modify or discontinue TYENNE if abnormal liver tests persist or worsen or if clinical signs and symptoms of liver disease develop. (2.10, 5.3)
- Laboratory monitoring-recommended due to potential consequences of treatment-related changes in neutrophils, platelets, lipids, and liver function tests. (2.10, 5.4)
- Hypersensitivity reactions, including anaphylaxis and death and serious cutaneous reactions including Drug Reaction with Eosinophilia and Systemic Symptoms (DRESS) - discontinue TYENNE, treat promptly, and monitor until reaction resolves (5.6)
- Live vaccines-Avoid use with TYENNE (5.9, 7.3)

6 ADVERSE REACTIONS

Most common adverse reactions (incidence of at least 5%): upper respiratory tract infections, nasopharyngitis, headache, hypertension, increased ALT, injection site reactions. (6)

To report SUSPECTED ADVERSE REACTIONS, contact Fresenius Kabi USA, LLC at 1-800-551-7176 or FDA at 1-800-FDA-1088 or www.fda.gov/medwatch

8 USE IN SPECIFIC POPULATIONS

- Pregnancy: Based on animal data, may cause fetal harm. (8.1)
- Lactation: Discontinue drug or nursing taking into consideration importance of drug to mother. (8.2)

FULL PRESCRIBING INFORMATION

WARNING: RISK OF SERIOUS INFECTIONS

Patients treated with tocilizumab products including TYENNE are at increased risk for developing serious infections that may lead to hospitalization or death [see Warnings and Precautions (5.1), Adverse Reactions (6.1)]. Most patients who developed these infections were taking concomitant immunosuppressants such as methotrexate or corticosteroids.

If a serious infection develops, interrupt TYENNE until the infection is controlled.

Reported infections include:

- Active tuberculosis, which may present with pulmonary or extrapulmonary disease. Patients, except those with COVID-19, should be tested for latent tuberculosis before TYENNE use and during therapy. Treatment for latent infection should be initiated prior to TYENNE use.
- Invasive fungal infections, including candidiasis, aspergillosis, and pneumocystis. Patients with invasive fungal infections may present with disseminated, rather than localized, disease.
- Bacterial, viral and other infections due to opportunistic pathogens.

The risks and benefits of treatment with TYENNE should be carefully considered prior to initiating therapy in patients with chronic or recurrent infection.

Patients should be closely monitored for the development of signs and symptoms of infection during and after treatment with TYENNE including the possible development of tuberculosis in patients who tested negative for latent tuberculosis infection prior to initiating therapy [see Warnings and Precautions (5.1)].

1 INDICATIONS AND USAGE

1.1 Rheumatoid Arthritis (RA)

TYENNE® (tocilizumab-aazg) is indicated for the treatment of adult patients with moderately to severely active rheumatoid arthritis who have had an inadequate response to one or more Disease-Modifying Anti-Rheumatic Drugs (DMARDs).

1.2 Giant Cell Arteritis (GCA)

TYENNE® (tocilizumab-aazg) is indicated for the treatment of giant cell arteritis (GCA) in adult patients.

1.3 Polyarticular Juvenile Idiopathic Arthritis (PJIA)

TYENNE® (tocilizumab-aazg) is indicated for the treatment of active polyarticular juvenile idiopathic arthritis in patients 2 years of age and older.

1.4 Systemic Juvenile Idiopathic Arthritis (SJIA)

TYENNE® (tocilizumab-aazg) is indicated for the treatment of active systemic juvenile idiopathic arthritis in patients 2 years of age and older.

1.5 Cytokine Release Syndrome (CRS)

TYENNE® (tocilizumab-aazg) is indicated for the treatment of chimeric antigen receptor (CAR) T cell-induced severe or life-threatening cytokine release syndrome in adults and pediatric patients 2 years of age and older.

1.6 Coronavirus Disease 2019 (COVID-19)

TYENNE® (tocilizumab-aazg) is indicated for the treatment of coronavirus disease 2019 (COVID-19) in hospitalized adult patients who are receiving systemic corticosteroids and require supplemental oxygen, noninvasive or invasive mechanical ventilation, or extracorporeal membrane oxygenation (ECMO).

2 DOSAGE AND ADMINISTRATION

2.1 General Considerations for Administration

Not Recommended for Concomitant Use with Biological DMARDs

Tocilizumab products have not been studied in combination with biological DMARDs such as TNF antagonists, IL-1R antagonists, anti-CD20 monoclonal antibodies and selective co-stimulation modulators because of the possibility of increased immunosuppression and increased risk of infection. Avoid using TYENNE with biological DMARDs.

Baseline Laboratory Evaluation Prior to Treatment

Obtain and assess baseline complete blood count (CBC) and liver function tests prior to treatment.

RA, GCA, PJIA and SJIA – It is recommended that TYENNE not be initiated in patients with an absolute neutrophil count (ANC) below 2,000 per mm^3, platelet count below 100,000 per mm^3, or ALT or AST above 1.5 times the upper limit of normal (ULN) [see Warnings and Precautions (5.3, 5.4)].

CRS – Patients with severe or life-threatening CRS frequently have cytopenias or elevated ALT or AST due to the lymphodepleting chemotherapy or the CRS. The decision to administer TYENNE should take into account the potential benefit of treating the CRS versus the risks of short-term treatment with TYENNE.

COVID-19 – It is recommended that TYENNE not be initiated in patients with an absolute neutrophil count (ANC) below 1,000 per mm^3, platelet count below 50,000 mm^3, or ALT or AST above 10 times ULN [see Warnings and Precautions (5.3, 5.4)].

2.2 Recommended Dosage for Rheumatoid Arthritis

TYENNE may be used as monotherapy or concomitantly with methotrexate or other non-biologic DMARDs as an intravenous infusion or as a subcutaneous injection.

Recommended Intravenous Dosage Regimen:

The recommended dosage of TYENNE for adult patients given as a 60-minute single intravenous drip infusion is 4 mg per kg every 4 weeks followed by an increase to 8 mg per kg every 4 weeks based on clinical response.

- Reduction of dose from 8 mg per kg to 4 mg per kg is recommended for management of certain dose-related laboratory changes including elevated liver enzymes, neutropenia, and thrombocytopenia [see Dosage and Administration (2.10), Warnings and Precautions (5.3, 5.4), and Adverse Reactions (6.1)].
- Doses exceeding 800 mg per infusion are not recommended in RA patients [see Clinical Pharmacology (12.3)].

Recommended Subcutaneous Dosage Regimen:

Patients less than 100 kg weight | 162 mg administered subcutaneously every other week, followed by an increase to every week based on clinical response
Patients at or above 100 kg weight | 162 mg administered subcutaneously every week

When transitioning from TYENNE intravenous therapy to subcutaneous administration administer the first subcutaneous dose instead of the next scheduled intravenous dose.

Interruption of dose or reduction in frequency of administration of subcutaneous dose from every week to every other week dosing is recommended for management of certain dose-related laboratory changes including elevated liver enzymes, neutropenia, and thrombocytopenia [see Dosage and Administration (2.10), Warnings and Precautions (5.3, 5.4), and Adverse Reactions (6.2)].

2.3 Recommended Dosage for Giant Cell Arteritis

Recommended Intravenous Dosage Regimen:

The recommended dosage of TYENNE for adult patients given as a 60-minute single intravenous drip infusion is 6 mg per kg every 4 weeks in combination with a tapering course of glucocorticoids.

TYENNE can be used alone following discontinuation of glucocorticoids.

- Interruption of dosing may be needed for management of dose-related laboratory abnormalities including elevated liver enzymes, neutropenia, and thrombocytopenia [see Dosage and Administration (2.10)].
- Doses exceeding 600 mg per infusion are not recommended in GCA patients [see Clinical Pharmacology (12.3)].

Recommended Subcutaneous Dosage Regimen:

The recommended dose of TYENNE for adult patients with GCA is 162 mg given once every week as a subcutaneous injection in combination with a tapering course of glucocorticoids.

A dose of 162 mg given once every other week as a subcutaneous injection in combination with a tapering course of glucocorticoids may be prescribed based on clinical considerations.

TYENNE can be used alone following discontinuation of glucocorticoids.

When transitioning from TYENNE intravenous therapy to subcutaneous administration, administer the first subcutaneous dose instead of the next scheduled intravenous dose.

Interruption of dose or reduction in frequency of administration of subcutaneous dose from every week to every other week dosing may be needed for management of dose-related laboratory abnormalities including elevated liver enzymes, neutropenia, and thrombocytopenia [see Dosage and Administration (2.10)].

2.4 Recommended Dosage for Polyarticular Juvenile Idiopathic Arthritis

TYENNE may be used as an intravenous infusion or as a subcutaneous injection alone or in combination with methotrexate. Do not change dose based solely on a single visit body weight measurement, as weight may fluctuate.

Recommended Intravenous Dosage Regimen:

The recommended dosage of TYENNE for PJIA patients given once every 4 weeks as a 60-minute single intravenous drip infusion is:

Recommended Intravenous PJIA Dosage Every 4 Weeks
Patients less than 30 kg weight | 10 mg per kg
Patients at or above 30 kg weight | 8 mg per kg

Recommended Subcutaneous Dosage Regimen:

Recommended Subcutaneous PJIA Dosage
Patients less than 30 kg weight | 162 mg once every 3 weeks
Patients at or above 30 kg weight | 162 mg once every 2 weeks

When transitioning from TYENNE intravenous therapy to subcutaneous administration, administer the first subcutaneous dose instead of the next scheduled intravenous dose.

Interruption of dosing may be needed for management of dose-related laboratory abnormalities including elevated liver enzymes, neutropenia, and thrombocytopenia [see Dosage and Administration (2.10)].

2.5 Recommended Dosage for Systemic Juvenile Idiopathic Arthritis

TYENNE may be used as an intravenous infusion or as a subcutaneous injection alone or in combination with methotrexate. Do not change a dose based solely on a single visit body weight measurement, as weight may fluctuate.

Recommended Intravenous Dosage Regimen:

The recommended dose of TYENNE for SJIA patients given once every 2 weeks as a 60-minute single intravenous drip infusion is:

Recommended Intravenous SJIA Dosage Every 2 Weeks
Patients less than 30 kg weight | 12 mg per kg
Patients at or above 30 kg weight | 8 mg per kg

Recommended Subcutaneous Dosage Regimen:

Recommended Subcutaneous SJIA Dosage
Patients less than 30 kg weight | 162 mg once every two weeks
Patients at or above 30 kg weight | 162 mg once every week

When transitioning from TYENNE intravenous therapy to subcutaneous administration, administer the first subcutaneous dose when the next scheduled intravenous dose is due.

Interruption of dosing may be needed for management of dose-related laboratory abnormalities including elevated liver enzymes, neutropenia, and thrombocytopenia [see Dosage and Administration (2.10)].

2.6 Recommended Dosage for Cytokine Release Syndrome (CRS)

Use only the intravenous route for treatment of CRS. The recommended dose of TYENNE for treatment of CRS given as a 60-minute intravenous infusion is:

Recommended Intravenous CRS Dosage
Patients less than 30 kg weight | 12 mg per kg
Patients at or above 30 kg weight | 8 mg per kg
Alone or in combination with corticosteroids

- If no clinical improvement in the signs and symptoms of CRS occurs after the first dose, up to 3 additional doses of TYENNE may be administered. The interval between consecutive doses should be at least 8 hours.
- Doses exceeding 800 mg per infusion are not recommended in CRS patients.
- Subcutaneous administration is not approved for CRS.

2.7 Coronavirus Disease 2019 (COVID-19)

Administer TYENNE by intravenous infusion only.

The recommended dosage of TYENNE for treatment of adult patients with COVID-19 is 8 mg per kg administered as a single 60-minute intravenous infusion. If clinical signs or symptoms worsen or do not improve after the first dose, one additional infusion of TYENNE may be administered at least 8 hours after the initial infusion.

- Doses exceeding 800 mg per infusion are not recommended in patients with COVID-19.
- Subcutaneous administration is not approved for COVID-19.

2.8 Preparation and Administration Instructions for Intravenous Infusion

TYENNE for intravenous infusion should be diluted by a healthcare professional using aseptic technique as follows:

- Use a sterile needle and syringe to prepare TYENNE.
- Patients less than 30 kg: use a 50 mL infusion bag or bottle of 0.9% or 0.45% Sodium Chloride Injection, USP, and then follow steps 1 and 2 below.
- Patients at or above 30 kg weight: use a 100 mL infusion bag or bottle, and then follow steps 1 and 2 below.
- Step 1. Withdraw a volume of 0.9% or 0.45% Sodium Chloride Injection, USP, equal to the volume of the TYENNE injection required for the patient's dose from the infusion bag or bottle [see Dosage and Administration (2.2, 2.4, 2.5, 2.6)].

For Intravenous Use: Volume of TYENNE Injection per kg of Body Weight
Dosage | Indication | Volume of TYENNE injection per kg of body weight
4 mg/kg | Adult RA | 0.2 mL/kg
6 mg/kg | Adult GCA | 0.3 mL/kg
8 mg/kg | Adult RA; Adult COVID-19; SJIA, PJIA and CRS (greater than or equal to 30 kg of body weight) | 0.4 mL/kg
10 mg/kg | PJIA (less than 30 kg of body weight) | 0.5 mL/kg
12 mg/kg | SJIA and CRS (less than 30 kg of body weight) | 0.6 mL/kg

- Step 2. Withdraw the amount of TYENNE for intravenous infusion from the vial(s) and add slowly into the 0.9% or 0.45% Sodium Chloride Injection, USP infusion bag or bottle. To mix the solution, gently invert the bag to avoid foaming.
- The prepared solution for infusion should be used immediately. If not used immediately, the diluted tocilizumab solutions may be refrigerated at 36°F to 46°F (2°C to 8°C) up to 24 hours, or stored at room temperature at or below 77°F (25°C) for up to 4 hours and should be protected from light. Administration of diluted TYENNE solution must be completed within this period of time.
- TYENNE solutions do not contain preservatives; therefore, unused product remaining in the vials should not be used.
- Allow the fully diluted TYENNE solution to reach room temperature prior to infusion.
- The infusion should be administered over 60 minutes and must be administered with an infusion set. Do not administer as an intravenous push or bolus.
- TYENNE should not be infused concomitantly in the same intravenous line with other drugs. No physical or biochemical compatibility studies have been conducted to evaluate the co-administration of TYENNE with other drugs.
- Parenteral drug products should be inspected visually for particulate matter and discoloration prior to administration, whenever solution and container permit. If particulates and discolorations are noted, the product should not be used.
- Fully diluted TYENNE solutions are compatible with polypropylene, polyethylene and polyvinyl chloride infusion bags and bottles, and glass infusion bottles.

2.9 Preparation and Administration Instructions for Subcutaneous Injection

- TYENNE for subcutaneous injection is not intended for intravenous drip infusion.
- Assess suitability of patient for subcutaneous home use and instruct patients to inform a healthcare professional before administering the next dose if they experience any symptoms of allergic reaction. Patients should seek immediate medical attention if they develop symptoms of serious allergic reactions. TYENNE subcutaneous injection is intended for use under the guidance of a healthcare practitioner. After proper training in subcutaneous injection technique, a patient may self-inject TYENNE or the patient's caregiver may administer TYENNE if a healthcare practitioner determines that it is appropriate. PJIA and SJIA patients may self-inject with the TYENNE prefilled syringe or autoinjector, or the patient's caregiver may administer TYENNE if both the healthcare practitioner and the parent/legal guardian determine it is appropriate [see Use in Specific Populations (8.4)].
  Patients, or patient caregivers, should be instructed to follow the directions provided in the Instructions for Use (IFU) for additional details on medication administration.
- Parenteral drug products should be inspected visually for particulate matter and discoloration prior to administration, whenever solution and container permit. Do not use TYENNE prefilled syringes (PFS) or prefilled autoinjectors exhibiting particulate matter, cloudiness, or discoloration. TYENNE for subcutaneous administration should be clear and colorless to pale yellow. Do not use if any part of the PFS or autoinjector appears to be damaged.
- Patients using TYENNE for subcutaneous administration should be instructed to inject the full amount in the syringe (0.9 mL) or full amount in the autoinjector (0.9 mL), which provides 162 mg of TYENNE, according to the directions provided in the IFU.
- Injection sites should be rotated with each injection and should never be given into moles, scars, or areas where the skin is tender, bruised, red, hard, or not intact.

2.10 Dosage Modifications due to Serious Infections or Laboratory Abnormalities

Serious Infections

Hold TYENNE treatment if a patient develops a serious infection until the infection is controlled.

Laboratory Abnormalities

Rheumatoid Arthritis and Giant Cell Arteritis

Liver Enzyme Abnormalities [see Warnings and Precautions (5.3, 5.4)]
Lab Value | Recommendation for RA | Recommendation for GCA
Greater than 1 to 3x ULN | Dose modify concomitant DMARDs if appropriate For persistent increases in this range:; - For patients receiving intravenous TYENNE, reduce dose to 4 mg per kg or hold TYENNE until ALT or AST have normalized - For patients receiving subcutaneous TYENNE, reduce injection frequency to every other week or hold dosing until ALT or AST have normalized. Resume TYENNE at every other week and increase frequency to every week as clinically appropriate | Dose modify immunomodulatory agents if appropriate For persistent increases in this range:; - For patients receiving Intravenous TYENNE, hold TYENNE until ALT or AST have normalized - For patients receiving subcutaneous TYENNE, reduce injection frequency to every other week or hold dosing until ALT or AST have normalized. Resume TYENNE at every other week and increase frequency to every week as clinically appropriate
Greater than 3 to 5x ULN (confirmed by repeat testing) | Hold TYENNE dosing until less than 3x ULN and follow recommendations above for greater than 1 to 3x ULN For persistent increases greater than 3x ULN, discontinue TYENNE | Hold TYENNE dosing until less than 3x ULN and follow recommendations above for greater than 1 to 3x ULN For persistent increases greater than 3x ULN, discontinue TYENNE
Greater than 5x ULN | Discontinue TYENNE | Discontinue TYENNE

Low Absolute Neutrophil Count (ANC) [see Warnings and Precautions (5.4)]
Lab Value (cells per mm^3) | Recommendation for RA | Recommendation for GCA
ANC greater than 1,000 | Maintain dose | Maintain dose
ANC 500 to 1,000 | Hold TYENNE dosing When ANC greater than 1,000 cells per mm^3:; - For patients receiving intravenous TYENNE, resume TYENNE at 4 mg per kg and increase to 8 mg per kg as clinically appropriate - For patients receiving subcutaneous TYENNE, resume TYENNE at every other week and increase frequency to every week as clinically appropriate | Hold TYENNE dosing When ANC greater than 1,000 cells per mm^3:; - For patients receiving intravenous TYENNE, resume TYENNE at 6 mg per kg - For patients receiving subcutaneous TYENNE, resume TYENNE at every other week and increase frequency to every week as clinically appropriate
ANC less than 500 | Discontinue TYENNE | Discontinue TYENNE

Low Platelet Count [see Warnings and Precautions (5.4)]
Lab Value (cells per mm^3) | Recommendation for RA | Recommendation for GCA
50,000 to 100,000 | Hold TYENNE dosing When platelet count is greater than 100,000 cells per mm^3:; - For patients receiving intravenous TYENNE, resume TYENNE at 4 mg per kg and increase to 8 mg per kg as clinically appropriate - For patients receiving subcutaneous TYENNE, resume TYENNE at every other week and increase frequency to every week as clinically appropriate | Hold TYENNE dosing When platelet count is greater than 100,000 cells per mm^3:; - For patients receiving intravenous TYENNE, resume TYENNE at 6 mg per kg - For patients receiving subcutaneous TYENNE, resume TYENNE at every other week and increase frequency to every week as clinically appropriate
Less than 50,000 | Discontinue TYENNE | Discontinue TYENNE

Polyarticular and Systemic Juvenile Idiopathic Arthritis

Dose reduction of tocilizumab products has not been studied in the PJIA and SJIA populations. Dose interruptions of TYENNE are recommended for liver enzyme abnormalities, low neutrophil counts, and low platelet counts in patients with PJIA and SJIA at levels similar to what is outlined above for patients with RA and GCA. If appropriate, dose modify or stop concomitant methotrexate and/or other medications and hold TYENNE dosing until the clinical situation has been evaluated. In PJIA and SJIA the decision to discontinue TYENNE for a laboratory abnormality should be based upon the medical assessment of the individual patient.

3 DOSAGE FORMS AND STRENGTHS

Intravenous Infusion

Injection: 80 mg/4 mL (20 mg/mL), 200 mg/10 mL (20 mg/mL), 400 mg/20 mL (20 mg/mL) as a clear and colorless to pale yellow solution in single-dose vials for further dilution prior to intravenous infusion.

Subcutaneous Injection

Injection: 162 mg/0.9 mL clear and colorless to pale yellow solution in a single-dose prefilled syringe or single-dose prefilled autoinjector.

4 CONTRAINDICATIONS

TYENNE is contraindicated in patients with known hypersensitivity to tocilizumab products [see Warnings and Precautions (5.6)].

5 WARNINGS AND PRECAUTIONS

5.1 Serious Infections

Serious and sometimes fatal infections due to bacterial, mycobacterial, invasive fungal, viral, protozoal, or other opportunistic pathogens have been reported in patients receiving immunosuppressive agents including tocilizumab products. The most common serious infections included pneumonia, urinary tract infection, cellulitis, herpes zoster, gastroenteritis, diverticulitis, sepsis and bacterial arthritis [see Adverse Reactions (6.1)]. Among opportunistic infections, tuberculosis, cryptococcus, aspergillosis, candidiasis, and pneumocystosis were reported with tocilizumab products. Other serious infections, not reported in clinical studies, may also occur (e.g., histoplasmosis, coccidioidomycosis, listeriosis). Patients have presented with disseminated rather than localized disease, and were often taking concomitant immunosuppressants such as methotrexate or corticosteroids which in addition to rheumatoid arthritis may predispose them to infections.

Do not administer TYENNE in patients with an active infection, including localized infections. The risks and benefits of treatment should be considered prior to initiating TYENNE in patients:

- with chronic or recurrent infection;
- who have been exposed to tuberculosis;
- with a history of serious or an opportunistic infection;
- who have resided or traveled in areas of endemic tuberculosis or endemic mycoses; or
- with underlying conditions that may predispose them to infection.

Closely monitor patients for the development of signs and symptoms of infection during and after treatment with TYENNE, as signs and symptoms of acute inflammation may be lessened due to suppression of the acute phase reactants [see Dosage and Administration (2.1), Adverse Reactions (6.1), and Patient Counseling Information (17)].

Hold TYENNE if a patient develops a serious infection, an opportunistic infection, or sepsis. A patient who develops a new infection during treatment with TYENNE should undergo a prompt and complete diagnostic workup appropriate for an immunocompromised patient, initiate appropriate antimicrobial therapy, and closely monitor the patient.

COVID-19

In patients with COVID-19, monitor for signs and symptoms of new infections during and after treatment with TYENNE. There is limited information regarding the use of tocilizumab products in patients with COVID-19 and concomitant active serious infections. The risks and benefits of treatment with TYENNE in COVID-19 patients with other concurrent infections should be considered.

Tuberculosis

Evaluate patients for tuberculosis risk factors and test for latent infection prior to initiating TYENNE. In patients with COVID-19, testing for latent infection is not necessary prior to initiating treatment with TYENNE.

Consider anti-tuberculosis therapy prior to initiation of TYENNE in patients with a past history of latent or active tuberculosis in whom an adequate course of treatment cannot be confirmed, and for patients with a negative test for latent tuberculosis but having risk factors for tuberculosis infection. Consultation with a physician with expertise in the treatment of tuberculosis is recommended to aid in the decision whether initiating anti-tuberculosis therapy is appropriate for an individual patient.

Closely monitor patients for the development of signs and symptoms of tuberculosis including patients who tested negative for latent tuberculosis infection prior to initiating therapy.

The incidence of tuberculosis in worldwide clinical development programs is 0.1%. Patients with latent tuberculosis should be treated with standard antimycobacterial therapy before initiating TYENNE.

Viral Reactivation

Viral reactivation has been reported with immunosuppressive biologic therapies and cases of herpes zoster exacerbation were observed in clinical studies with tocilizumab. No cases of Hepatitis B reactivation were observed in the trials; however patients who screened positive for hepatitis were excluded.

5.2 Gastrointestinal Perforations

Events of gastrointestinal perforation have been reported in clinical trials, primarily as complications of diverticulitis in patients treated with tocilizumab. Use TYENNE with caution in patients who may be at increased risk for gastrointestinal perforation. Promptly evaluate patients presenting with fever, new onset abdominal symptoms, and a change in bowel habits for early identification of gastrointestinal perforation [see Adverse Reactions (6.1)].

5.3 Hepatotoxicity

Serious cases of hepatic injury have been observed in patients taking intravenous or subcutaneous tocilizumab products. Some of these cases have resulted in liver transplant or death. Time to onset for cases ranged from months to years after treatment initiation with tocilizumab products. While most cases presented with marked elevations of transaminases (> 5 times ULN), some cases presented with signs or symptoms of liver dysfunction and only mildly elevated transaminases.

During randomized controlled studies, treatment with tocilizumab was associated with a higher incidence of transaminase elevations [see Adverse Reactions (6.1, 6.2, 6.5, 6.7)]. Increased frequency and magnitude of these elevations was observed when potentially hepatotoxic drugs (e.g., MTX) were used in combination with tocilizumab.

For RA and GCA patients, obtain a liver test panel (serum alanine aminotransferase [ALT], aspartate aminotransferase [AST], alkaline phosphatase, and total bilirubin) before initiating TYENNE, every 4 to 8 weeks after start of therapy for the first 6 months of treatment and every 3 months thereafter. It is not recommended to initiate TYENNE treatment in RA or GCA patients with elevated transaminases ALT or AST greater than 1.5x ULN. In patients who develop elevated ALT or AST greater than 5x ULN, discontinue TYENNE. For recommended modifications based upon increase in transaminases [see Dosage and Administration (2.10)].

Patients hospitalized with COVID-19 may have elevated ALT or AST levels. Multi-organ failure with involvement of the liver is recognized as a complication of severe COVID-19. The decision to administer TYENNE should balance the potential benefit of treating COVID-19 against the potential risks of acute treatment with TYENNE. It is not recommended to initiate TYENNE treatment in COVID-19 patients with elevated ALT or AST above 10 x ULN. Monitor ALT and AST during treatment.

Measure liver tests promptly in patients who report symptoms that may indicate liver injury, such as fatigue, anorexia, right upper abdominal discomfort, dark urine or jaundice. In this clinical context, if the patient is found to have abnormal liver tests (e.g., ALT greater than three times the upper limit of the reference range, serum total bilirubin greater than two times the upper limit of the reference range), TYENNE treatment should be interrupted and investigation done to establish the probable cause. TYENNE should only be restarted in patients with another explanation for the liver test abnormalities after normalization of the liver tests.

A similar pattern of liver enzyme elevation is noted with tocilizumab products treatment in the PJIA and SJIA populations. Monitor liver test panel at the time of the second administration and thereafter every 4 to 8 weeks for PJIA and every 2 to 4 weeks for SJIA.

5.4 Changes in Laboratory Parameters

Patients with Rheumatoid Arthritis, Giant Cell Arteritis and Coronavirus Disease 2019

Neutropenia

Treatment with tocilizumab products was associated with a higher incidence of neutropenia. Infections have been uncommonly reported in association with treatment-related neutropenia in long-term extension studies and postmarketing clinical experience.

- It is not recommended to initiate TYENNE treatment in RA and GCA patients with a low neutrophil count, i.e., absolute neutrophil count (ANC) less than 2000 per mm^3. In patients who develop an absolute neutrophil count less than 500 per mm^3 treatment is not recommended.
- Monitor neutrophils 4 to 8 weeks after start of therapy and every 3 months thereafter [see Clinical Pharmacology (12.2)]. For recommended modifications based on ANC results [see Dosage and Administration (2.10)].
- It is not recommended to initiate TYENNE treatment in COVID-19 patients with an ANC less than 1000 per mm^3. Neutrophils should be monitored.

Thrombocytopenia

Treatment with tocilizumab products was associated with a reduction in platelet counts. Treatment-related reduction in platelets was not associated with serious bleeding events in clinical trials [see Adverse Reactions (6.1, 6.2)].

- It is not recommended to initiate TYENNE treatment in RA and GCA patients with a platelet count below 100,000 per mm^3. In patients who develop a platelet count less than 50,000 per mm^3 treatment is not recommended.
- Monitor platelets 4 to 8 weeks after start of therapy and every 3 months thereafter. For recommended modifications based on platelet counts [see Dosage and Administration (2.10)].
- In COVID-19 patients with a platelet count less than 50,000 per mm^3, treatment is not recommended. Platelets should be monitored.

Elevated Liver Enzymes

Refer to 5.3 Hepatotoxicity. For recommended modifications [see Dosage and Administration (2.10)].

Lipid Abnormalities

Treatment with tocilizumab products was associated with increases in lipid parameters such as total cholesterol, triglycerides, LDL cholesterol, and/or HDL cholesterol [see Adverse Reactions (6.1, 6.2)].

- Assess lipid parameters approximately 4 to 8 weeks following initiation of TYENNE therapy.
- Subsequently, manage patients according to clinical guidelines [e.g., National Cholesterol Educational Program (NCEP)] for the management of hyperlipidemia.

Patients with Polyarticular and Systemic Juvenile Idiopathic Arthritis

A similar pattern of liver enzyme elevation, low neutrophil count, low platelet count and lipid elevations is noted with tocilizumab products treatment in the PJIA and SJIA populations. Monitor neutrophils, platelets, ALT and AST at the time of the second administration and thereafter every 4 to 8 weeks for PJIA and every 2 to 4 weeks for SJIA. Monitor lipids as above for approved adult indications [see Dosage and Administration (2.10)].

5.5 Immunosuppression

The impact of treatment with tocilizumab products on the development of malignancies is not known but malignancies were observed in clinical studies [see Adverse Reactions (6.1)]. TYENNE is an immunosuppressant, and treatment with immunosuppressants may result in an increased risk of malignancies.

5.6 Hypersensitivity Reactions, Including Anaphylaxis

Hypersensitivity reactions, including anaphylaxis, have been reported in association with tocilizumab products and anaphylactic events with a fatal outcome have been reported with intravenous infusion of tocilizumab products. Anaphylaxis and other hypersensitivity reactions that required treatment discontinuation were reported in 0.1% (3 out of 2644) of patients in the 6-month controlled trials of intravenous tocilizumab, 0.2% (8 out of 4009) of patients in the intravenous all-exposure RA population, 0.7% (8 out of 1068) in the subcutaneous 6-month controlled RA trials, and in 0.7% (10 out of 1465) of patients in the subcutaneous all-exposure population. In the SJIA controlled trial with intravenous tocilizumab, 1 out of 112 patients (0.9%) experienced hypersensitivity reactions that required treatment discontinuation. In the PJIA controlled trial with intravenous tocilizumab, 0 out of 188 patients (0%) in the tocilizumab all-exposure population experienced hypersensitivity reactions that required treatment discontinuation. Reactions that required treatment discontinuation included generalized erythema, rash, and urticaria. Injection site reactions were categorized separately [see Adverse Reactions (6)].

In the postmarketing setting, events of hypersensitivity reactions, including anaphylaxis and death have occurred in patients treated with a range of doses of intravenous tocilizumab products, with or without concomitant therapies. Events have occurred in patients who received premedication. Hypersensitivity, including anaphylaxis events, have occurred both with and without previous hypersensitivity reactions and as early as the first infusion of tocilizumab products [see Adverse Reactions (6.11)]. In addition, serious cutaneous reactions, including Drug Reaction with Eosinophilia and Systemic Symptoms (DRESS), have been reported in patients with autoinflammatory conditions treated with tocilizumab products.

TYENNE for intravenous use should only be infused by a healthcare professional with appropriate medical support to manage anaphylaxis. For TYENNE subcutaneous injection, advise patients to seek immediate medical attention if they experience any symptoms of a hypersensitivity reaction. If a hypersensitivity reaction occurs, immediately discontinue TYENNE, treat promptly and monitor until signs and symptoms resolve.

5.7 Demyelinating Disorders

The impact of treatment with tocilizumab products on demyelinating disorders is not known, but multiple sclerosis and chronic inflammatory demyelinating polyneuropathy were reported rarely in RA clinical studies. Monitor patients for signs and symptoms potentially indicative of demyelinating disorders. Prescribers should exercise caution in considering the use of TYENNE in patients with preexisting or recent onset demyelinating disorders.

5.8 Active Hepatic Disease and Hepatic Impairment

Treatment with TYENNE is not recommended in patients with active hepatic disease or hepatic impairment [see Adverse Reactions (6.1), Use in Specific Populations (8.6)].

5.9 Vaccinations

Avoid use of live vaccines concurrently with TYENNE as clinical safety has not been established. No data are available on the secondary transmission of infection from persons receiving live vaccines to patients receiving tocilizumab products.

No data are available on the effectiveness of vaccination in patients receiving tocilizumab products. Because IL-6 inhibition may interfere with the normal immune response to new antigens, it is recommended that all patients, particularly pediatric or elderly patients, if possible, be brought up to date with all immunizations in agreement with current immunization guidelines prior to initiating TYENNE therapy. The interval between live vaccinations and initiation of TYENNE therapy should be in accordance with current vaccination guidelines regarding immunosuppressive agents.

6 ADVERSE REACTIONS

The following serious adverse reactions are described elsewhere in labeling:

- Serious Infections [see Warnings and Precautions (5.1)]
- Gastrointestinal Perforations [see Warnings and Precautions (5.2)]
- Laboratory Parameters [see Warnings and Precautions (5.4)]
- Immunosuppression [see Warnings and Precautions (5.5)]
- Hypersensitivity Reactions, Including Anaphylaxis [see Warnings and Precautions (5.6)]
- Demyelinating Disorders [see Warnings and Precautions (5.7)]
- Active Hepatic Disease and Hepatic Impairment [see Warnings and Precautions (5.8)]

Because clinical studies are conducted under widely varying conditions, adverse reaction rates observed in the clinical studies of a drug cannot be directly compared to rates in the clinical studies of another drug and may not predict the rates observed in a broader patient population in clinical practice.

6.1 Clinical Trials Experience in Rheumatoid Arthritis Patients Treated with Intravenous Tocilizumab (tocilizumab-IV)

The tocilizumab-IV data in rheumatoid arthritis (RA) includes 5 double-blind, controlled, multicenter studies. In these studies, patients received doses of tocilizumab-IV 8 mg per kg monotherapy (288 patients), tocilizumab-IV 8 mg per kg in combination with DMARDs (including methotrexate) (1582 patients), or tocilizumab-IV 4 mg per kg in combination with methotrexate (774 patients).

The all exposure population includes all patients in registration studies who received at least one dose of tocilizumab-IV. Of the 4009 patients in this population, 3577 received treatment for at least 6 months, 3309 for at least one year; 2954 received treatment for at least 2 years and 2189 for 3 years.

All patients in these studies had moderately to severely active rheumatoid arthritis. The study population had a mean age of 52 years, 82% were female and 74% were Caucasian.

The most common serious adverse reactions were serious infections [see Warnings and Precautions (5.1)]. The most commonly reported adverse reactions in controlled studies up to 24 weeks (occurring in at least 5% of patients treated with tocilizumab-IV monotherapy or in combination with DMARDs) were upper respiratory tract infections, nasopharyngitis, headache, hypertension and increased ALT.

The proportion of patients who discontinued treatment due to any adverse reactions during the double-blind, placebo-controlled studies was 5% for patients taking tocilizumab-IV and 3% for placebo-treated patients. The most common adverse reactions that required discontinuation of tocilizumab-IV were increased hepatic transaminase values (per protocol requirement) and serious infections.

Overall Infections

In the 24 week, controlled clinical studies, the rate of infections in the tocilizumab-IV monotherapy group was 119 events per 100 patient-years and was similar in the methotrexate monotherapy group. The rate of infections in the 4 mg per kg and 8 mg per kg tocilizumab-IV plus DMARD group was 133 and 127 events per 100 patient-years, respectively, compared to 112 events per 100 patient-years in the placebo plus DMARD group. The most commonly reported infections (5% to 8% of patients) were upper respiratory tract infections and nasopharyngitis.

The overall rate of infections with tocilizumab-IV in the all exposure population remained consistent with rates in the controlled periods of the studies.

Serious Infections

In the 24 week, controlled clinical studies, the rate of serious infections in the tocilizumab-IV monotherapy group was 3.6 per 100 patient-years compared to 1.5 per 100 patient-years in the methotrexate group. The rate of serious infections in the 4 mg per kg and 8 mg per kg tocilizumab-IV plus DMARD group was 4.4 and 5.3 events per 100 patient-years, respectively, compared to 3.9 events per 100 patient-years in the placebo plus DMARD group.

In the all-exposure population, the overall rate of serious infections remained consistent with rates in the controlled periods of the studies. The most common serious infections included pneumonia, urinary tract infection, cellulitis, herpes zoster, gastroenteritis, diverticulitis, sepsis and bacterial arthritis. Cases of opportunistic infections have been reported [see Warnings and Precautions (5.1)].

In the cardiovascular outcomes Study WA25204, the rate of serious infections in the tocilizumab 8 mg/kg IV every 4 weeks group, with or without DMARD, was 4.5 per 100 patient-years, and the rate in the etanercept 50 mg weekly SC group, with or without DMARD, was 3.2 per 100 patient-years [see Clinical Studies (14.1)].

Gastrointestinal Perforations

During the 24 week, controlled clinical trials, the overall rate of gastrointestinal perforation was 0.26 events per 100 patient-years with tocilizumab-IV therapy.

In the all-exposure population, the overall rate of gastrointestinal perforation remained consistent with rates in the controlled periods of the studies. Reports of gastrointestinal perforation were primarily reported as complications of diverticulitis including generalized purulent peritonitis, lower GI perforation, fistula and abscess. Most patients who developed gastrointestinal perforations were taking concomitant nonsteroidal anti-inflammatory medications (NSAIDs), corticosteroids, or methotrexate [see Warnings and Precautions (5.2)]. The relative contribution of these concomitant medications versus tocilizumab-IV to the development of GI perforations is not known.

Infusion Reactions

In the 24 week, controlled clinical studies, adverse events associated with the infusion (occurring during or within 24 hours of the start of infusion) were reported in 8% and 7% of patients in the 4 mg per kg and 8 mg per kg tocilizumab-IV plus DMARD group, respectively, compared to 5% of patients in the placebo plus DMARD group. The most frequently reported event on the 4 mg per kg and 8 mg per kg dose during the infusion was hypertension (1% for both doses), while the most frequently reported event occurring within 24 hours of finishing an infusion were headache (1% for both doses) and skin reactions (1% for both doses), including rash, pruritus and urticaria. These events were not treatment limiting.

Anaphylaxis

Hypersensitivity reactions requiring treatment discontinuation, including anaphylaxis, associated with tocilizumab-IV were reported in 0.1% (3 out of 2644) in the 24 week, controlled trials and in 0.2% (8 out of 4009) in the all-exposure population. These reactions were generally observed during the second to fourth infusion of tocilizumab-IV. Appropriate medical treatment should be available for immediate use in the event of a serious hypersensitivity reaction [see Warnings and Precautions 5.6)].

Laboratory Abnormalities

Neutropenia

In the 24 week, controlled clinical studies, decreases in neutrophil counts below 1000 per mm^3 occurred in 1.8% and 3.4% of patients in the 4 mg per kg and 8 mg per kg tocilizumab-IV plus DMARD group, respectively, compared to 0.1% of patients in the placebo plus DMARD group.

Approximately half of the instances of ANC below 1000 per mm^3 occurred within 8 weeks of starting therapy. Decreases in neutrophil counts below 500 per mm^3 occurred in 0.4% and 0.3% of patients in the 4 mg per kg and 8 mg per kg tocilizumab-IV plus DMARD, respectively, compared to 0.1% of patients in the placebo plus DMARD group. There was no clear relationship between decreases in neutrophils below 1000 per mm^3 and the occurrence of serious infections.

In the all-exposure population, the pattern and incidence of decreases in neutrophil counts remained consistent with what was seen in the 24 week controlled clinical studies [see Warnings and Precautions (5.4)].

Thrombocytopenia

In the 24 week, controlled clinical studies, decreases in platelet counts below 100,000 per mm^3 occurred in 1.3% and 1.7% of patients on 4 mg per kg and 8 mg per kg tocilizumab-IV plus DMARD, respectively, compared to 0.5% of patients on placebo plus DMARD, without associated bleeding events.

In the all-exposure population, the pattern and incidence of decreases in platelet counts remained consistent with what was seen in the 24 week controlled clinical studies [see Warnings and Precautions 5.4)].

Elevated Liver Enzymes

Liver enzyme abnormalities are summarized in Table 1. In patients experiencing liver enzyme elevation, modification of treatment regimen, such as reduction in the dose of concomitant DMARD, interruption of tocilizumab-IV, or reduction in tocilizumab-IV dose, resulted in decrease or normalization of liver enzymes [see Dosage and Administration (2.1)]. These elevations were not associated with clinically relevant increases in direct bilirubin, nor were they associated with clinical evidence of hepatitis or hepatic insufficiency [see Warnings and Precautions (5.3, 5.4)].

Table 1 Incidence of Liver Enzyme Abnormalities in the 24 Week Controlled Period of Studies I to V*
 | Tocilizumab 8 mg per kg MONOTHERAPY | Methotrexate | Tocilizumab 4 mg per kg + DMARDs | Tocilizumab 8 mg per kg + DMARDs | Placebo + DMARDs
 | N = 288 | N = 284 | N = 774 | N = 1582 | N = 1170
 | (%) | (%) | (%) | (%) | (%)
AST (U/L)
> ULN to 3x ULN | 22 | 26 | 34 | 41 | 17
> 3x ULN to 5x ULN | 0.3 | 2 | 1 | 2 | 0.3
> 5x ULN | 0.7 | 0.4 | 0.1 | 0.2 | < 0.1
ALT (U/L)
> ULN to 3x ULN | 36 | 33 | 45 | 48 | 23
> 3x ULN to 5x ULN | 1 | 4 | 5 | 5 | 1
> 5x ULN | 0.7 | 1 | 1.3 | 1.5 | 0.3
ULN = Upper Limit of Normal
*For a description of these studies, see Section 14, Clinical Studies.

In the all-exposure population, the elevations in ALT and AST remained consistent with what was seen in the 24 week, controlled clinical trials.

In Study WA25204, of the 1538 patients with moderate to severe RA [see Clinical Studies (14.1)] and treated with tocilizumab, elevations in ALT or AST >3 x ULN occurred in 5.3% and 2.2% patients, respectively. One serious event of drug induced hepatitis with hyperbilirubinemia was reported in association with tocilizumab.

Lipids

Elevations in lipid parameters (total cholesterol, LDL, HDL, triglycerides) were first assessed at 6 weeks following initiation of tocilizumab-IV in the controlled 24 week clinical trials.

Increases were observed at this time point and remained stable thereafter. Increases in triglycerides to levels above 500 mg per dL were rarely observed. Changes in other lipid parameters from baseline to week 24 were evaluated and are summarized below:

- Mean LDL increased by 13 mg per dL in the tocilizumab 4 mg per kg+DMARD arm, 20 mg per dL in the tocilizumab 8 mg per kg+DMARD, and 25 mg per dL in tocilizumab 8 mg per kg monotherapy.
- Mean HDL increased by 3 mg per dL in the tocilizumab 4 mg per kg+DMARD arm, 5 mg per dL in the tocilizumab 8 mg per kg+DMARD, and 4 mg per dL in tocilizumab 8 mg per kg monotherapy.
- Mean LDL/HDL ratio increased by an average of 0.14 in the tocilizumab 4 mg per kg+DMARD arm, 0.15 in the tocilizumab 8 mg per kg+DMARD, and 0.26 in tocilizumab 8 mg per kg monotherapy.
- ApoB/ApoA1 ratios were essentially unchanged in tocilizumab-treated patients.
- Elevated lipids responded to lipid lowering agents.

In the all-exposure population, the elevations in lipid parameters remained consistent with what was seen in the 24 week, controlled clinical trials.

Immunogenicity

The observed incidence of anti-drug antibodies is highly dependent on the sensitivity and specificity of the assay. Differences in assay methods preclude meaningful comparisons of the incidence of anti-drug antibodies in the studies described below with the incidence of anti-drug antibodies in other studies, including those of tocilizumab or of other tocilizumab products.

In the 24 week, controlled clinical studies, a total of 2876 patients have been tested for anti-tocilizumab antibodies. Forty-six patients (2%) developed positive anti-tocilizumab antibodies, of whom 5 had an associated, medically significant, hypersensitivity reaction leading to withdrawal. Thirty patients (1%) developed neutralizing antibodies.

Malignancies

During the 24 week, controlled period of the studies, 15 malignancies were diagnosed in patients receiving tocilizumab-IV, compared to 8 malignancies in patients in the control groups. Exposure-adjusted incidence was similar in the tocilizumab-IV groups (1.32 events per 100 patient-years) and in the placebo plus DMARD group (1.37 events per 100 patient-years).

In the all-exposure population, the rate of malignancies remained consistent with the rate observed in the 24 week, controlled period [see Warnings and Precautions (5.5)].

Other Adverse Reactions

Adverse reactions occurring in 2% or more of patients on 4 or 8 mg per kg tocilizumab-IV plus DMARD and at least 1% greater than that observed in patients on placebo plus DMARD are summarized inTable 2.

Table 2 Adverse Reactions Occurring in at Least 2% or More of Patients on 4 or 8 mg per kg Tocilizumab plus DMARD and at Least 1% Greater Than That Observed in Patients on Placebo plus DMARD
24 Week Phase 3 Controlled Study Population
 | Tocilizumab 8 mg per kg MONOTHERAPY | Methotrexate | Tocilizumab 4 mg per kg + DMARDs | Tocilizumab 8 mg per kg + DMARDs | Placebo + DMARDs
Preferred Term | N = 288 | N = 284 | N = 774 | N = 1582 | N = 1170
 | (%) | (%) | (%) | (%) | (%)
Upper Respiratory Tract Infection | 7 | 5 | 6 | 8 | 6
Nasopharyngitis | 7 | 6 | 4 | 6 | 4
Headache | 7 | 2 | 6 | 5 | 3
Hypertension | 6 | 2 | 4 | 4 | 3
ALT increased | 6 | 4 | 3 | 3 | 1
Dizziness | 3 | 1 | 2 | 3 | 2
Bronchitis | 3 | 2 | 4 | 3 | 3
Rash | 2 | 1 | 4 | 3 | 1
Mouth Ulceration | 2 | 2 | 1 | 2 | 1
Abdominal Pain Upper | 2 | 2 | 3 | 3 | 2
Gastritis | 1 | 2 | 1 | 2 | 1
Transaminase increased | 1 | 5 | 2 | 2 | 1

Other infrequent and medically relevant adverse reactions occurring at an incidence less than 2% in rheumatoid arthritis patients treated with tocilizumab-IV in controlled trials were:

Infections and Infestations: oral herpes simplex

Gastrointestinal disorders: stomatitis, gastric ulcer

Investigations: weight increased, total bilirubin increased

Blood and lymphatic system disorders: leukopenia

General disorders and administration site conditions: edema peripheral

Respiratory, thoracic, and mediastinal disorders: dyspnea, cough

Eye disorders: conjunctivitis

Renal disorders: nephrolithiasis

Endocrine disorders: hypothyroidism

6.2 Clinical Trials Experience in Rheumatoid Arthritis Patients Treated with Subcutaneous Tocilizumab (tocilizumab-SC)

The tocilizumab-SC data in rheumatoid arthritis (RA) includes 2 double-blind, controlled, multicenter studies. Study SC-I was a non-inferiority study that compared the efficacy and safety of tocilizumab 162 mg administered every week subcutaneously and 8 mg/kg intravenously every four weeks in 1262 adult subjects with rheumatoid arthritis. Study SC-II was a placebo-controlled superiority study that evaluated the safety and efficacy of tocilizumab 162 mg administered every other week subcutaneously or placebo in 656 patients. All patients in both studies received background non-biologic DMARDs.

The safety observed for tocilizumab-SC administered subcutaneously was consistent with the known safety profile of intravenous tocilizumab, with the exception of injection site reactions (ISRs), which were more common with tocilizumab-SC compared with placebo SC injections (IV arm).

Injection Site Reactions

In the 6-month control period, in SC-I, the frequency of ISRs was 10.1% (64/631) and 2.4% (15/631) for the weekly tocilizumab-SC and placebo SC (IV-arm) groups, respectively. In SC-II, the frequency of ISRs was 7.1% (31/437) and 4.1% (9/218) for the every other week tocilizumab-SC and placebo groups, respectively. These ISRs (including erythema, pruritus, pain and hematoma) were mild to moderate in severity. The majority resolved without any treatment and none necessitated drug discontinuation.

Immunogenicity

In the 6-month control period in SC-I, 0.8% (5/625) in the tocilizumab-SC arm and 0.8% (5/627) in the IV arm developed anti-tocilizumab antibodies; of these, all developed neutralizing antibodies. In SC-II, 1.6% (7/434) in the tocilizumab-SC arm compared with 1.4 % (3/217) in the placebo arm developed anti-tocilizumab antibodies; of these, 1.4% (6/434) in the tocilizumab-SC arm and 0.5% (1/217) in the placebo arm also developed neutralizing antibodies.

A total of 1454 (>99%) patients who received tocilizumab-SC in the all exposure group have been tested for anti- tocilizumab antibodies. Thirteen patients (0.9%) developed anti-tocilizumab antibodies, and, of these, 12 patients (0.8%) developed neutralizing antibodies.

The rate is consistent with previous intravenous experience. No correlation of antibody development to adverse events or loss of clinical response was observed.

Laboratory Abnormalities

Neutropenia

During routine laboratory monitoring in the 6-month controlled clinical trials, a decrease in neutrophil count below 1 × 10^9/L occurred in 2.9% and 3.7% of patients receiving tocilizumab-SC weekly and every other week, respectively.

There was no clear relationship between decreases in neutrophils below 1 x 10^9/L and the occurrence of serious infections.

Thrombocytopenia

During routine laboratory monitoring in the tocilizumab-SC 6-month controlled clinical trials, none of the patients had a decrease in platelet count to ≤ 50,000/mm^3.

Elevated Liver Enzymes

During routine laboratory monitoring in the 6-month controlled clinical trials, elevation in ALT or AST ≥3 x ULN occurred in 6.5% and 1.4% of patients, respectively, receiving tocilizumab-SC weekly and 3.4% and 0.7% receiving tocilizumab-SC every other week.

Lipid Parameters Elevations

During routine laboratory monitoring in the tocilizumab-SC 6-month clinical trials, 19% of patients dosed weekly and 19.6% of patients dosed every other week and 10.2% of patients on placebo experienced sustained elevations in total cholesterol > 6.2 mmol/l (240 mg/dL), with 9%, 10.4% and 5.1% experiencing a sustained increase in LDL to 4.1 mmol/l (160 mg/dL) receiving tocilizumab-SC weekly, every other week and placebo, respectively.

6.3 Clinical Trials Experience in Giant Cell Arteritis Patients Treated with Subcutaneous Tocilizumab (tocilizumab-SC)

The safety of subcutaneous tocilizumab has been studied in one Phase III study (WA28119) with 251 GCA patients. The total patient years duration in the tocilizumab-SC GCA all exposure population was 138.5 patient years during the 12-month double blind, placebo-controlled phase of the study. The overall safety profile observed in the tocilizumab-SC treatment groups was generally consistent with the known safety profile of tocilizumab. There was an overall higher incidence of infections in GCA patients relative to RA patients.

The rate of infection/serious infection events was 200.2/9.7 events per 100 patient years in the tocilizumab-SC weekly group and 160.2/4.4 events per 100 patient years in the tocilizumab-SC every other week group as compared to 156.0/4.2 events per 100 patient years in the placebo + 26 week prednisone taper and 210.2/12.5 events per 100 patient years in the placebo + 52 week taper groups.

6.4 Clinical Trials Experience in Giant Cell Arteritis Patients Treated with Intravenous Tocilizumab (tocilizumab-IV)

The safety of tocilizumab-IV was studied in an open label PK-PD and safety study in 24 patients with GCA who were in remission on tocilizumab-IV at time of enrollment. Patients received tocilizumab 7 mg/kg every 4 weeks for 20 weeks, followed by 6 mg/kg every 4 weeks for 20 weeks. The total patient years exposure to treatment was 17.5 years. The overall safety profile observed for tocilizumab administered intravenously in GCA patients was consistent with the known safety profile of tocilizumab.

6.5 Clinical Trials Experience in Polyarticular Juvenile Idiopathic Arthritis Patients Treated With Intravenous Tocilizumab (tocilizumab-IV)

The safety of tocilizumab-IV was studied in 188 pediatric patients 2 to 17 years of age with PJIA who had an inadequate clinical response or were intolerant to methotrexate. The total patient exposure in the tocilizumab-IV all exposure population (defined as patients who received at least one dose of tocilizumab-IV) was 184.4 patient years. At baseline, approximately half of the patients were taking oral corticosteroids and almost 80% were taking methotrexate. In general, the types of adverse drug reactions in patients with PJIA were consistent with those seen in RA and SJIA patients [see Adverse Reactions (6.1 and 6.7)].

Infections

The rate of infections in the tocilizumab-IV all exposure population was 163.7 per 100 patient years. The most common events observed were nasopharyngitis and upper respiratory tract infections. The rate of serious infections was numerically higher in patients weighing less than 30 kg treated with 10 mg/kg tocilizumab (12.2 per 100 patient years) compared to patients weighing at or above 30 kg, treated with 8 mg/kg tocilizumab (4.0 per 100 patient years).

The incidence of infections leading to dose interruptions was also numerically higher in patients weighing less than 30 kg treated with 10 mg/kg tocilizumab (21%) compared to patients weighing at or above 30 kg, treated with 8 mg/kg tocilizumab (8%).

Infusion Reactions

In PJIA patients, infusion-related reactions are defined as all events occurring during or within 24 hours of an infusion. In the tocilizumab-IV all exposure population, 11 patients (6%) experienced an event during the infusion, and 38 patients (20.2%) experienced an event within 24 hours of an infusion. The most common events occurring during infusion were headache, nausea and hypotension, and occurring within 24 hours of infusion were dizziness and hypotension. In general, the adverse drug reactions observed during or within 24 hours of an infusion were similar in nature to those seen in RA and SJIA patients [see Adverse Reactions (6.1 and 6.7)].

No clinically significant hypersensitivity reactions associated with tocilizumab and requiring treatment discontinuation were reported.

Immunogenicity

One patient, in the 10 mg/kg less than 30 kg group, developed positive anti-tocilizumab antibodies without developing a hypersensitivity reaction and subsequently withdrew from the study.

Laboratory Abnormalities

Neutropenia

During routine laboratory monitoring in the tocilizumab-IV all exposure population, a decrease in neutrophil counts below 1 × 10^9 per L occurred in 3.7% of patients.

There was no clear relationship between decreases in neutrophils below 1 x 10^9 per L and the occurrence of serious infections.

Thrombocytopenia

During routine laboratory monitoring in the tocilizumab-IV all exposure population, 1% of patients had a decrease in platelet count at or less than 50,000 per mm^3 without associated bleeding events.

Elevated Liver Enzymes

During routine laboratory monitoring in the tocilizumab-IV all exposure population, elevation in ALT or AST at or greater than 3 x ULN occurred in 4% and less than 1% of patients, respectively.

Lipids

During routine laboratory monitoring in the tocilizumab all exposure population, elevation in total cholesterol greater than 1.5-2 x ULN occurred in one patient (0.5%) and elevation in LDL greater than 1.5-2 x ULN occurred in one patient (0.5%).

6.6 Clinical Trials Experience in Polyarticular Juvenile Idiopathic Arthritis Patients Treated With Subcutaneous Tocilizumab (tocilizumab-SC)

The safety of tocilizumab-SC was studied in 52 pediatric patients 1 to 17 years of age with PJIA who had an inadequate clinical response or were intolerant to methotrexate. The total patient exposure in the PJIA tocilizumab-SC population (defined as patients who received at least one dose of tocilizumab-SC and accounting for treatment discontinuation) was 49.5 patient years.

In general, the safety observed for tocilizumab administered subcutaneously was consistent with the known safety profile of intravenous tocilizumab, with the exception of injection site reactions (ISRs), and neutropenia.

Injection Site Reactions

During the 1-year study, a frequency of 28.8% (15/52) ISRs was observed in tocilizumab-SC treated PJIA patients. These ISRs occurred in a greater proportion of patients at or above 30 kg (44.0%) compared with patients below 30 kg (14.8%). All ISRs were mild in severity and none of the ISRs required patient withdrawal from treatment or dose interruption. A higher frequency of ISRs was observed in tocilizumab-SC treated PJIA patients compared to what was seen in adult RA or GCA patients [see Adverse Reactions (6.2 and 6.3)].

Immunogenicity

Three patients, 1 patient below 30 kg and 2 patients at or above 30 kg, developed positive anti-tocilizumab antibodies with neutralizing potential without developing a serious or clinically significant hypersensitivity reaction. One patient subsequently withdrew from the study.

Neutropenia

During routine laboratory monitoring in the tocilizumab-SC all exposure population, a decrease in neutrophil counts below 1 × 10^9 per L occurred in 15.4% of patients, and was more frequently observed in the patients less than 30 kg (25.9%) compared to patients at or above 30 kg (4.0%). There was no clear relationship between decreases in neutrophils below 1 x 10^9 per L and the occurrence of serious infections.

6.7 Clinical Trials Experience in Systemic Juvenile Idiopathic Arthritis Patients Treated with Intravenous Tocilizumab (tocilizumab-IV)

The data described below reflect exposure to tocilizumab-IV in one randomized, double-blind, placebo-controlled trial of 112 pediatric patients with SJIA 2 to 17 years of age who had an inadequate clinical response to nonsteroidal anti-inflammatory drugs (NSAIDs) or corticosteroids due to toxicity or lack of efficacy. At baseline, approximately half of the patients were taking 0.3 mg/kg/day corticosteroids or more, and almost 70% were taking methotrexate. The trial included a 12 week controlled phase followed by an open-label extension. In the 12 week double-blind, controlled portion of the clinical study 75 patients received treatment with tocilizumab-IV (8 or 12 mg per kg based upon body weight). After 12 weeks or at the time of escape, due to disease worsening, patients were treated with tocilizumab-IV in the open-label extension phase.

The most common adverse events (at least 5%) seen in tocilizumab-IV treated patients in the 12 week controlled portion of the study were: upper respiratory tract infection, headache, nasopharyngitis and diarrhea.

Infections

In the 12 week controlled phase, the rate of all infections in the tocilizumab-IV group was 345 per 100 patient-years and 287 per 100 patient-years in the placebo group. In the open label extension over an average duration of 73 weeks of treatment, the overall rate of infections was 304 per 100 patient-years.

In the 12 week controlled phase, the rate of serious infections in the tocilizumab-IV group was 11.5 per 100 patient years. In the open label extension over an average duration of 73 weeks of treatment, the overall rate of serious infections was 11.4 per 100 patient years. The most commonly reported serious infections included pneumonia, gastroenteritis, varicella, and otitis media.

Macrophage Activation Syndrome

In the 12 week controlled study, no patient in any treatment group experienced macrophage activation syndrome (MAS) while on assigned treatment; 3 per 112 (3%) developed MAS during open-label treatment with tocilizumab-IV. One patient in the placebo group escaped to tocilizumab-IV 12 mg per kg at Week 2 due to severe disease activity, and ultimately developed MAS at Day 70. Two additional patients developed MAS during the long-term extension. All 3 patients had tocilizumab-IV dose interrupted (2 patients) or discontinued (1 patient) for the MAS event, received treatment, and the MAS resolved without sequelae. Based on a limited number of cases, the incidence of MAS does not appear to be elevated in the tocilizumab-IV SJIA clinical development experience; however no definitive conclusions can be made.

Infusion Reactions

Patients were not premedicated, however most patients were on concomitant corticosteroids as part of their background treatment for SJIA. Infusion related reactions were defined as all events occurring during or within 24 hours after an infusion. In the 12 week controlled phase, 4% of tocilizumab-IV and 0% of placebo treated patients experienced events occurring during infusion. One event (angioedema) was considered serious and life-threatening, and the patient was discontinued from study treatment.

Within 24 hours after infusion, 16% of patients in the tocilizumab-IV treatment group and 5% of patients in the placebo group experienced an event. In the tocilizumab-IV group the events included rash, urticaria, diarrhea, epigastric discomfort, arthralgia and headache. One of these events, urticaria, was considered serious.

Anaphylaxis

Anaphylaxis was reported in 1 out of 112 patients (less than 1%) treated with tocilizumab-IV during the controlled and open label extension study [see Warnings and Precautions (5.6)].

Immunogenicity

All 112 patients were tested for anti-tocilizumab antibodies at baseline. Two patients developed positive anti- tocilizumab antibodies: one of these patients experienced serious adverse events of urticaria and angioedema consistent with an anaphylactic reaction which led to withdrawal; the other patient developed macrophage activation syndrome while on escape therapy and was discontinued from the study.

Laboratory Abnormalities

Neutropenia

During routine monitoring in the 12 week controlled phase, a decrease in neutrophil below 1 × 10^9 per L occurred in 7% of patients in the tocilizumab-IV group, and in no patients in the placebo group. In the open label extension over an average duration of 73 weeks of treatment, a decreased neutrophil count occurred in 17% of the tocilizumab-IV group. There was no clear relationship between decrease in neutrophils below 1 x 10^9 per L and the occurrence of serious infections.

Thrombocytopenia

During routine monitoring in the 12 week controlled phase, 1% of patients in the tocilizumab-IV group and 3% in the placebo group had a decrease in platelet count to no more than 100,000 per mm^3.

In the open label extension over an average duration of 73 weeks of treatment, decreased platelet count occurred in 4% of patients in the tocilizumab-IV group, with no associated bleeding.

Elevated Liver Enzymes

During routine laboratory monitoring in the 12 week controlled phase, elevation in ALT or AST at or above 3x ULN occurred in 5% and 3% of patients, respectively in the tocilizumab-IV group and in 0% of placebo patients.

In the open label extension over an average duration of 73 weeks of treatment, the elevation in ALT or AST at or above 3x ULN occurred in 13% and 5% of tocilizumab-IV treated patients, respectively.

Lipids

During routine laboratory monitoring in the 12 week controlled phase, elevation in total cholesterol greater than 1.5x ULN – 2x ULN occurred in 1.5% of the tocilizumab-IV group and in 0% of placebo patients. Elevation in LDL greater than 1.5x ULN – 2x ULN occurred in 1.9% of patients in the tocilizumab-IV group and 0% of the placebo group.

In the open label extension study over an average duration of 73 weeks of treatment, the pattern and incidence of elevations in lipid parameters remained consistent with the 12 week controlled study data.

6.8 Clinical Trials Experience in Systemic Juvenile Idiopathic Arthritis Patients Treated with Subcutaneous Tocilizumab (tocilizumab-SC)

The safety profile of tocilizumab-SC was studied in 51 pediatric patients 1 to 17 years of age with SJIA who had an inadequate clinical response to NSAIDs and corticosteroids. In general, the safety observed for tocilizumab administered subcutaneously was consistent with the known safety profile of intravenous tocilizumab, with the exception of ISRs where a higher frequency was observed in tocilizumab-SC treated SJIA patients compared to PJIA patients and adult RA or GCA patients [see Adverse Reactions (6.2, 6.3 and 6.6)].

Injection Site Reactions (ISRs)

A total of 41.2% (21/51) SJIA patients experienced ISRs to tocilizumab-SC. The most common ISRs were erythema, pruritus, pain, and swelling at the injection site. The majority of ISRs reported were Grade 1 events and all ISRs reported were non-serious and none required patient withdrawal from treatment or dose interruption.

Immunogenicity

Forty-six of the 51 (90.2%) patients who were tested for anti-tocilizumab antibodies at baseline had at least one post-baseline screening assay result. No patient developed positive anti-tocilizumab antibodies post-baseline.

6.9 Clinical Trials Experience in Patients with Cytokine Release Syndrome Treated with Intravenous Tocilizumab (tocilizumab-IV)

In a retrospective analysis of pooled outcome data from multiple clinical trials 45 patients were treated with tocilizumab 8 mg/kg (12 mg/kg for patients less than 30 kg) with or without additional high-dose corticosteroids for severe or life-threatening CAR T-cell-induced CRS. A median of 1 dose of tocilizumab (range, 1-4 doses) was administered. No adverse reactions related to tocilizumab were reported [see Clinical Studies (14.10)].

6.10 Clinical Trials Experience in COVID-19 Patients Treated with Intravenous Tocilizumab (tocilizumab-IV)

The safety of tocilizumab in hospitalized COVID-19 patients was evaluated in a pooled safety population that includes patients enrolled in EMPACTA, COVACTA, AND REMDACTA. The analysis of adverse reactions included a total of 974 patients exposed to tocilizumab. Patients received a single, 60-minute infusion of intravenous tocilizumab 8 mg/kg (maximum dose of 800 mg). If clinical signs or symptoms worsened or did not improve, one additional dose of tocilizumab 8 mg/kg could be administered between 8- 24 hours after the initial dose.

Adverse reactions summarized in Table 3 occurred in at least 3% of tocilizumab-treated patients and more commonly than in patients on placebo in the pooled safety population.

Table 3 Adverse Reactions^1 Identified From the Pooled COVID-19 Safety Population
Adverse Reaction | Tocilizumab 8 mg per kg N = 974 (%) | Placebo N = 483 (%)
Hepatic Transaminases increased | 10% | 8%
Constipation | 9% | 8%
Urinary tract infection | 5% | 4%
Hypertension | 4% | 1%
Hypokalaemia | 4% | 3%
Anxiety | 4% | 2%
Diarrhea | 4% | 2%
Insomnia | 4% | 3%
Nausea | 3% | 2%
^1Patients are counted once for each category regardless of the number of reactions

In the pooled safety population, the rates of infection/serious infection events were 30%/19% in patients receiving tocilizumab versus 32%/23% receiving placebo.

Laboratory Abnormalities

In the pooled safety population of EMPACTA, COVACTA, and REMDACTA, neutrophil counts <1000 cells/mcl occurred in 3.4% of patients who received tocilizumab and 0.5% of patients who received placebo. Platelet counts <50,000 cells/mcl occurred in 3.2% of patients who received tocilizumab and 1.5% of patients who received placebo. ALT or AST at or above 5x ULN occurred in 11.7% of patients who received tocilizumab and 9.9% of patients who received placebo.

6.11 Postmarketing Experience

The following adverse reactions have been identified during post-approval use of tocilizumab products. Because these reactions are reported voluntarily from a population of uncertain size, it is not always possible to reliably estimate their frequency or establish a causal relationship to drug exposure.

- Hypersensitivity Reactions: Fatal anaphylaxis, Stevens-Johnson Syndrome, Drug Reaction with Eosinophilia and Systemic Symptoms (DRESS) [see Warnings and Precautions (5.6)]
- Pancreatitis
- Drug-induced liver injury, Hepatitis, Hepatic failure, Jaundice [see Warnings and Precautions (5.3)]

7 DRUG INTERACTIONS

7.1 Concomitant Drugs for Treatment of Adult Indications

In RA patients, population pharmacokinetic analyses did not detect any effect of methotrexate (MTX), non-steroidal anti-inflammatory drugs or corticosteroids on tocilizumab clearance. Concomitant administration of a single intravenous dose of 10 mg/kg tocilizumab with 10-25 mg MTX once weekly had no clinically significant effect on MTX exposure. Tocilizumab products have not been studied in combination with biological DMARDs such as TNF antagonists [see Dosage and Administration (2.2)].

In GCA patients, no effect of concomitant corticosteroid on tocilizumab exposure was observed.

7.2 Interactions with CYP450 Substrates

Cytochrome P450s in the liver are down-regulated by infection and inflammation stimuli including cytokines such as IL-6. Inhibition of IL-6 signaling in RA patients treated with tocilizumab products may restore CYP450 activities to higher levels than those in the absence of tocilizumab products leading to increased metabolism of drugs that are CYP450 substrates. In vitro studies showed that tocilizumab has the potential to affect expression of multiple CYP enzymes including CYP1A2, CYP2B6, CYP2C9, CYP2C19, CYP2D6 and CYP3A4. Its effect on CYP2C8 or transporters is unknown. In vivo studies with omeprazole, metabolized by CYP2C19 and CYP3A4, and simvastatin, metabolized by CYP3A4, showed up to a 28% and 57% decrease in exposure one week following a single dose of tocilizumab, respectively. The effect of tocilizumab products on CYP enzymes may be clinically relevant for CYP450 substrates with narrow therapeutic index, where the dose is individually adjusted.

Upon initiation or discontinuation of TYENNE, in patients being treated with these types of medicinal products, perform therapeutic monitoring of effect (e.g., warfarin) or drug concentration (e.g., cyclosporine or theophylline) and the individual dose of the medicinal product adjusted as needed. Exercise caution when coadministering TYENNE with CYP3A4 substrate drugs where decrease in effectiveness is undesirable, e.g., oral contraceptives, lovastatin, atorvastatin, etc. The effect of tocilizumab products on CYP450 enzyme activity may persist for several weeks after stopping therapy [see Clinical Pharmacology (12.3)].

7.3 Live Vaccines

Avoid use of live vaccines concurrently with TYENNE [see Warnings and Precautions (5.9)].

8 USE IN SPECIFIC POPULATIONS

8.1 Pregnancy

Risk Summary

The available data with tocilizumab products from a pregnancy exposure registry, retrospective cohort study, pharmacovigilance, and published literature are insufficient to draw conclusions about a drug-associated risk of major birth defects, miscarriage, or other adverse maternal or fetal outcomes. These studies had methodological limitations, including small sample size of tocilizumab exposed groups, missing exposure and outcomes information, and lack of adjustment for cofounders. Monoclonal antibodies, such as tocilizumab products, are actively transported across the placenta during the third trimester of pregnancy and may affect immune response in the in utero exposed infant [see Clinical Considerations]. In animal reproduction studies, intravenous administration of tocilizumab to Cynomolgus monkeys during organogenesis caused abortion/embryo-fetal death at doses 1.25 times and higher than the maximum recommended human dose by the intravenous route of 8 mg per kg every 2 to 4 weeks. The literature in animals suggests that inhibition of IL-6 signaling may interfere with cervical ripening and dilatation and myometrial contractile activity leading to potential delays of parturition [see Data]. Based on the animal data, there may be a potential risk to the fetus.

The estimated background risk of major birth defects and miscarriage for the indicated population is unknown. All pregnancies have a background risk of birth defect, loss or other adverse outcomes. In the U.S. general population, the estimated background risk of major birth defects and miscarriage in clinically recognized pregnancies is 2 to 4% and 15 to 20%, respectively.

Clinical Considerations

Fetal/Neonatal adverse reactions

Monoclonal antibodies are increasingly transported across the placenta as pregnancy progresses, with the largest amount transferred during the third trimester. Risks and benefits should be considered prior to administering live or live-attenuated vaccines to infants exposed to TYENNE in utero [see Warnings and Precautions 5.9)].

Disease-associated Maternal Risk

Published data suggest that the risk of adverse pregnancy outcomes in women with rheumatoid arthritis is associated with increased disease activity. Adverse pregnancy outcomes include preterm delivery (before 37 weeks of gestation), low birth weight (less than 2500 g) infants, and small for gestational age at birth.

Data

Animal Data

An embryo-fetal developmental toxicity study was performed in which pregnant Cynomolgus monkeys were treated intravenously with tocilizumab at daily doses of 2, 10, or 50 mg/ kg during organogenesis from gestation day (GD) 20-50. Although there was no evidence for a teratogenic/dysmorphogenic effect at any dose, tocilizumab produced an increase in the incidence of abortion/embryo-fetal death at doses 1.25 times and higher the MRHD by the intravenous route at maternal intravenous doses of 10 and 50 mg/ kg. Testing of a murine analogue of tocilizumab in mice did not yield any evidence of harm to offspring during the pre- and postnatal development phase when dosed at 50 mg/kg intravenously with treatment every three days from implantation (GD 6) until post-partum day 21 (weaning). There was no evidence for any functional impairment of the development and behavior, learning ability, immune competence and fertility of the offspring.

Parturition is associated with significant increases of IL-6 in the cervix and myometrium. The literature suggests that inhibition of IL-6 signaling may interfere with cervical ripening and dilatation and myometrial contractile activity leading to potential delays of parturition. For mice deficient in IL-6 (ll6-/- null mice), parturition was delayed relative to wild-type (ll6+/+) mice.

Administration of recombinant IL-6 to ll6-/- null mice restored the normal timing of delivery.

8.2 Lactation

Risk Summary

No information is available on the presence of tocilizumab products in human milk, the effects of the drug on the breastfed infant, or the effects of the drug on milk production. Maternal immunoglobulin G (IgG) is present in human milk. If tocilizumab products are transferred into human milk, the effects of local exposure in the gastrointestinal tract and potential limited systemic exposure in the infant to tocilizumab products are unknown.

The lack of clinical data during lactation precludes clear determination of the risk of tocilizumab products to an infant during lactation; therefore the developmental and health benefits of breastfeeding should be considered along with the mother's clinical need for TYENNE and the potential adverse effects on the breastfed child from TYENNE or from the underlying maternal condition.

8.4 Pediatric Use

TYENNE by intravenous use is indicated for the treatment of pediatric patients with:

- Active systemic juvenile idiopathic arthritis in patients 2 years of age and older
- Active polyarticular juvenile idiopathic arthritis in patients 2 years of age and older
- Severe or life-threatening CAR T cell-induced cytokine release syndrome (CRS) in patients 2 years of age and older.

TYENNE by subcutaneous use is indicated for the treatment of pediatric patients with:

- Active polyarticular juvenile idiopathic arthritis in patients 2 years of age and older
- Active systemic juvenile idiopathic arthritis in patients 2 years of age and older

The safety and effectiveness of TYENNE in pediatric patients with conditions other than PJIA, SJIA or CRS have not been established. The safety and effectiveness in pediatric patients below the age of 2 have not been established in PJIA, SJIA or CRS.

Systemic Juvenile Idiopathic Arthritis – Intravenous Use

A multicenter, open-label, single arm study to evaluate the PK, safety and exploratory PD and efficacy of tocilizumab over 12-weeks in SJIA patients (N=11) under 2 years of age was conducted. Patients received intravenous tocilizumab 12 mg/kg every two weeks. Concurrent use of stable background treatment with corticosteroids, MTX, and/or non-steroidal anti-inflammatory drugs was permitted.

Patients who completed the 12-week period could continue to the optional extension period (a total of 52-weeks or until the age of 2 years, whichever was longer).

The primary PK endpoints (Cmax, Ctrough and AUC2weeks) of tocilizumab at steady-state in this study were within the ranges of these parameters observed in patients with SJIA aged 2 to 17 years.

The safety and immunogenicity of tocilizumab for patients with SJIA under 2 years of age was assessed descriptively. SAEs, AEs leading to discontinuation, and infectious AEs were reported by 27.3%, 36.4%, and 81.8% of patients. Six patients (54.5%) experienced hypersensitivity reactions, defined as all adverse events occurring during or within 24 hours after an infusion considered related to tocilizumab. Three of these patients experienced serious hypersensitivity reactions and were withdrawn from the study. Three patients with hypersensitivity reactions (two with serious hypersensitivity reactions) developed treatment induced anti- tocilizumab antibodies after the event. There were no cases of MAS based on the protocol-specified criteria, but 2 cases of suspected MAS based on Ravelli criteria [Ravelli A, Minoia F, Davì S on behalf of the Paediatric Rheumatology International Trials Organisation, the Childhood Arthritis and Rheumatology Research Alliance, the Pediatric Rheumatology Collaborative Study Group, and the Histiocyte Society, et al. 2016 Classification Criteria for Macrophage Activation Syndrome Complicating Systemic Juvenile Idiopathic Arthritis. Annals of the Rheumatic Diseases 2016;75:481-489.] .

Cytokine Release Syndrome – Intravenous Use
In the retrospective analysis of pooled outcome data for patients treated with tocilizumab for CAR T cell-induced CRS, 25 patients were children (2 years up to 12 years of age), and 17 patients were adolescents (12 years up to 18 years of age). There were no differences between the pediatric patients and the adults for safety or efficacy.

8.5 Geriatric Use

Of the 2644 patients who received tocilizumab in Studies I to V [see Clinical Studies (14)], a total of 435 rheumatoid arthritis patients were 65 years of age and older, including 50 patients 75 years and older. Of the 1069 patients who received tocilizumab-SC in studies SC-I and SC-II there were 295 patients 65 years of age and older, including 41 patients 75 years and older. The frequency of serious infection among tocilizumab treated subjects 65 years of age and older was higher than those under the age of 65. As there is a higher incidence of infections in the elderly population in general, caution should be used when treating the elderly.

Clinical studies that included tocilizumab for CRS did not include sufficient numbers of patients aged 65 and over to determine whether they respond differently from younger patients.
In the EMPACTA, COVACTA, and REMDACTA studies, of the 974 COVID-19 patients in the tocilizumab arm, 375 (39%) were 65 years of age or older. No overall differences in safety or effectiveness of tocilizumab were observed between patients 65 years of age and older and those under the age of 65 years of age in these studies [see Adverse Reactions (6.1) and Clinical Studies (14.11)].

In the RECOVERY study, of the 2022 COVID-19 patients in the tocilizumab arm, 930 (46%) were 65 years of age or older. No overall differences in effectiveness of tocilizumab were observed between patients 65 years of age and older and those under the age 65 years of age in this study [see Clinical Studies (14.11)].

8.6 Hepatic Impairment

The safety and efficacy of tocilizumab products have not been studied in patients with hepatic impairment, including patients with positive HBV and HCV serology [see Warnings and Precautions (5.8)].

8.7 Renal Impairment

No dose adjustment is required in patients with mild or moderate renal impairment. Tocilizumab products have not been studied in patients with severe renal impairment [see Clinical Pharmacology (12.3)].

9 DRUG ABUSE AND DEPENDENCE

No studies on the potential for tocilizumab products to cause dependence have been performed. However, there is no evidence from the available data that tocilizumab products treatment results in dependence.

10 OVERDOSAGE

There are limited data available on overdoses with tocilizumab products. One case of accidental overdose was reported with intravenous tocilizumab in which a patient with multiple myeloma received a dose of 40 mg per kg. No adverse drug reactions were observed. No serious adverse drug reactions were observed in healthy volunteers who received single doses of up to 28 mg per kg, although all 5 patients at the highest dose of 28 mg per kg developed dose-limiting neutropenia.

In case of an overdose, it is recommended that the patient be monitored for signs and symptoms of adverse reactions. Patients who develop adverse reactions should receive appropriate symptomatic treatment.

11 DESCRIPTION

Tocilizumab-aazg is a recombinant humanized anti-human interleukin 6 (IL-6) receptor monoclonal antibody of the immunoglobulin IgG1κ (gamma 1, kappa) subclass with a typical H2L2 polypeptide structure. Each light chain and heavy chain consists of 214 and 448 amino acids (excluding the C-terminal lysine), respectively.

The four polypeptide chains are linked intra- and inter-molecularly by disulfide bonds. Tocilizumab-aazg has a molecular weight of approximately 148 kDa. The antibody is produced in mammalian (Chinese hamster ovary) cells.

Intravenous Infusion

TYENNE (tocilizumab-aazg) injection is a sterile, clear and colorless to pale yellow, histidine buffered preservative-free solution with a pH of approximately 6 for further dilution prior to intravenous infusion. Each single-dose vial is available at a concentration of 20 mg/mL containing 80 mg/4 mL, 200 mg/10 mL, or 400 mg/20 mL of TYENNE. Each mL of solution contains arginine (17.4 mg), histidine (3.1 mg), lactic acid (0.9 mg), polysorbate 80 (0.2 mg), sodium chloride (0.6 mg), and Water for Injection, USP. Hydrochloric acid and sodium hydroxide are added to adjust the pH.

Subcutaneous Injection

TYENNE (tocilizumab-aazg) injection is a sterile, clear, colorless to pale yellow, preservative-free, histidine buffered solution with a pH of approximately 6 for subcutaneous use. It is supplied in a ready-to-use, single-dose 0.9 mL prefilled syringe (PFS) with a needle safety device or in a ready-to-use, single-dose 0.9 mL autoinjector that delivers 162 mg tocilizumab-aazg, arginine (16.7 mg), histidine (2.0 mg), lactic acid (0.9 mg), polysorbate 80 (0.2 mg), sodium chloride (0.6 mg), and Water for Injection, USP. Hydrochloric acid and sodium hydroxide are added to adjust the pH.

12 CLINICAL PHARMACOLOGY

12.1 Mechanism of Action

Tocilizumab products bind to both soluble and membrane-bound IL-6 receptors (sIL-6R and mIL-6R), and have been shown to inhibit IL-6-mediated signaling through these receptors. IL-6 is a pleiotropic pro-inflammatory cytokine produced by a variety of cell types including T- and B-cells, lymphocytes, monocytes and fibroblasts. IL-6 has been shown to be involved in diverse physiological processes such as T-cell activation, induction of immunoglobulin secretion, initiation of hepatic acute phase protein synthesis, and stimulation of hematopoietic precursor cell proliferation and differentiation. IL-6 is also produced by synovial and endothelial cells leading to local production of IL-6 in joints affected by inflammatory processes such as rheumatoid arthritis.

12.2 Pharmacodynamics

In clinical studies in RA patients with the 4 mg per kg and 8 mg per kg intravenous doses or the 162 mg weekly and every other weekly subcutaneous doses of tocilizumab, decreases in levels of C-reactive protein (CRP) to within normal ranges were seen as early as week 2. Changes in pharmacodynamic parameters were observed (i.e., decreases in rheumatoid factor, erythrocyte sedimentation rate (ESR), serum amyloid A, fibrinogen and increases in hemoglobin) with doses, however the greatest improvements were observed with 8 mg per kg tocilizumab. Pharmacodynamic changes were also observed to occur after tocilizumab administration in GCA, PJIA, and SJIA patients (decreases in CRP, ESR, and increases in hemoglobin). The relationship between these pharmacodynamic findings and clinical efficacy is not known.

In healthy subjects administered tocilizumab in doses from 2 to 28 mg per kg intravenously and 81 to 162 mg subcutaneously, absolute neutrophil counts decreased to the nadir 3 to 5 days following tocilizumab administration. Thereafter, neutrophils recovered towards baseline in a dose dependent manner. Rheumatoid arthritis and GCA patients demonstrated a similar pattern of absolute neutrophil counts following tocilizumab administration [see Warnings and Precautions (5.4)].

12.3 Pharmacokinetics

PK of tocilizumab is characterized by nonlinear elimination which is a combination of linear clearance and Michaelis-Menten elimination. The nonlinear part of tocilizumab elimination leads to an increase in exposure that is more than dose-proportional. The pharmacokinetic parameters of tocilizumab do not change with time. Due to the dependence of total clearance on tocilizumab serum concentrations, the half-life of tocilizumab is also concentration-dependent and varies depending on the serum concentration level. Population pharmacokinetic analyses in any patient population tested so far indicate no relationship between apparent clearance and the presence of anti-drug antibodies.

Rheumatoid Arthritis – Intravenous and Subcutaneous Administration

The pharmacokinetics in healthy subjects and RA patients suggest that PK is similar between the two populations.

The population PK model was developed from an analysis dataset composed of an IV dataset of 1793 patients from Study I, Study III, Study IV, and Study V, and from an IV and SC dataset of 1759 patients from Studies SC-I and SC-II. Cmean is included in place of AUCtau, since for dosing regimens with different inter-dose intervals, the mean concentration over the dosing period characterizes the comparative exposure better than AUCtau.

At high serum concentrations, when total clearance of tocilizumab is dominated by linear clearance, a terminal half-life of approximately 21.5 days was derived from the population parameter estimates.

For doses of 4 mg/kg tocilizumab given every 4 weeks intravenously, the estimated median (range) Cmax, Ctrough, and Cmean of tocilizumab at steady state were 86.1 (44.8–202) mcg/mL, 0.1 (0.0–14.6) mcg/mL, and 18.0 (8.9– 50.7) mcg/mL, respectively. For doses of 8 mg/kg tocilizumab given every 4 weeks intravenously, the estimated median (range) Cmax, Ctrough, and Cmean of tocilizumab were 176 (75.4–557) mcg/mL, 13.4 (0.1–154) mcg/mL, and 54.0 (17–260) mcg/mL, respectively. Cmax increased dose-proportionally between doses of 4 and 8 mg/kg IV every 4 weeks, while a greater than dose-proportional increase was observed in Cmean and Ctrough. At steady-state, Cmean and Ctrough were 3.0 and 134 fold higher at 8 mg/kg as compared to 4 mg/kg, respectively.

The accumulation ratios for AUC and Cmax after multiple doses of 4 and 8 mg/kg IV Q4W are low, while the accumulation ratios for Ctrough are higher (2.62 and 2.47, respectively). For Cmax, greater than 90% of the steady-state value was reached after the 1st IV infusion. For AUCtau and Cmean, 90% of the steady-state value was reached after the 1st and 3rd infusion for 4 mg/kg and 8 mg/kg IV, while for Ctrough, approximately 90% of the steady-state value was reached after the 4th IV infusion after both doses.

For doses of 162 mg given every other week subcutaneously, the estimated median (range) steady-state Cmax, Ctrough, and Cmean of tocilizumab were 12.1 (0.4–49.3) mcg/mL, 4.1 (0.0–34.2) mcg/mL, and 9.2 (0.2– 43.6) mcg/mL, respectively.

For doses of 162 mg given every week subcutaneously, the estimated median (range) steady-state Cmax, Ctrough, and Cmean of tocilizumab were 49.8 (3–150) mcg/mL, 42.9 (1.3–144) mcg/mL, and 47.3 (2.4–147) mcg/mL, respectively. Exposures after the 162 mg SC QW regimen were greater by 5.1 (Cmean) to 10.5 fold (Ctrough) compared to the 162 mg SC Q2W regimen.

Accumulation ratios after multiple doses of either SC regimen were higher than after IV regimen with the highest ratios for Ctrough (6.02 and 6.30, for 162 mg SC Q2W and 162 mg SC QW, respectively). The higher accumulation for Ctrough was expected based on the nonlinear clearance contribution at lower concentrations. For Cmax, greater than 90% of the steady-state value was reached after the 5th SC and the 12th SC injection with the Q2W and QW regimens, respectively. For AUCtau and Cmean, 90% of the steady-state value was reached after the 6th and 12th injections for the 162 mg SC Q2W and QW regimens, respectively. For Ctrough, approximately 90% of the steady-state value was reached after the 6th and 12th injections for the 162 mg SC Q2W and QW regimens, respectively.

Population PK analysis identified body weight as a significant covariate impacting the pharmacokinetics of tocilizumab. When given IV on a mg/kg basis, individuals with body weight ≥ 100 kg are predicted to have mean steady-state exposures higher than mean values for the patient population. Therefore, tocilizumab doses exceeding 800 mg per infusion are not recommended in patients with RA [see Dosage and Administration (2.2)]. Due to the flat dosing employed for SC administration of tocilizumab, no modifications are necessary by this dosing route.

Giant Cell Arteritis – Subcutaneous and Intravenous Administration

The pharmacokinetics of tocilizumab S C in GCA patients was determined using a population pharmacokinetic analysis on a dataset composed of 149 GCA patients treated with 162 mg subcutaneously every week or with 162 mg subcutaneously every other week.

For the 162 mg every week dose, the estimated median (range) steady-state Cmax, Ctrough and Cmean of tocilizumab SC were 72.1 (12.2–151) mcg/mL, 67.2 (10.7–145) mcg/mL, and 70.6 (11.7–149) mcg/mL, respectively. The accumulation ratios for Cmean or AUCtau, Ctrough, and Cmax were 10.9, 9.6, and 8.9, respectively. Steady state was reached after 17 weeks. For the 162 mg every other week dose, the estimated median (range) steady-state Cmax, Ctrough, and Cmean of tocilizumab were 17.2 (1.1–56.2) mcg/mL, 7.7 (0.1–37.3) mcg/mL, and 13.7 (0.5– 49) mcg/mL, respectively. The accumulation ratios for Cmean or AUCtau, Ctrough, and Cmax were 2.8, 5.6, and 2.3 respectively. Steady-state was reached after 14 weeks.

The pharmacokinetics of tocilizumab IV in GCA patients was characterized by a non-compartmental pharmacokinetic analysis which included 22 patients treated with 6 mg/kg intravenously every 4 weeks for 20 weeks. The median (range) Cmax, Ctrough and Cmean of tocilizumab at steady state were 178 (115-320) mcg/mL, 22.7 (3.38-54.5) mcg/mL and 57.5 (32.9-110) mcg/mL, respectively. Steady state trough concentrations were within the range observed in GCA patients treated with 162 mg TCZ SC administered every week or every other week. Based on pharmacokinetic exposure and extrapolation between RA and GCA patients, when given IV on a mg/kg basis, tocilizumab doses exceeding 600 mg per infusion are not recommended in patients with GCA [see Dosage and Administration (2.3)].

Polyarticular Juvenile Idiopathic Arthritis – Intravenous and Subcutaneous Administration

The pharmacokinetics of tocilizumab (TCZ) in PJIA patients was characterized by a population pharmacokinetic analysis which included 188 patients who were treated with TCZ IV or 52 patients treated with TCZ SC.

For doses of 8 mg/kg tocilizumab (patients with a body weight at or above 30 kg) given every 4 weeks intravenously, the estimated median (range) Cmax, Ctrough, and Cmean of tocilizumab at steady state were 181 (114–331) mcg/mL, 3.28 (0.02–35.4) mcg/mL, and 38.6 (22.2–83.8) mcg/mL, respectively. For doses of 10 mg/kg tocilizumab (patients with a body weight less than 30 kg) given every 4 weeks intravenously, the estimated median (range) Cmax, Ctrough, and Cmean of tocilizumab were 167 (125–220) mcg/mL, 0.35 (0– 11.8) mcg/mL, and 30.8 (16.0–48.0) mcg/mL, respectively.

The accumulation ratios were 1.05 and 1.16 for AUC4weeks, and 1.43 and 2.22 for Ctrough for 10 mg/kg (BW less than 30 kg) and 8 mg/kg (BW at or above 30 kg) intravenous doses, respectively. No accumulation for Cmax was observed. Following 10 mg/kg and 8 mg/kg TCZ IV every 4 weeks doses in PJIA patients (aged 2 to 17 years), steady state concentrations (trough and average) were within the range of exposures in adult RA patients following 4 mg/kg and 8 mg/kg every 4 weeks, and steady state peak concentrations in PJIA patients were comparable to those following 8 mg/kg every 4 weeks in adult RA patients.

For doses of 162 mg tocilizumab (patients with a body weight at or above 30 kg) given every 2 weeks subcutaneously, the estimated median (range) Cmax, Ctrough, and Cmean of tocilizumab were 29.7 (7.56–50.3) mcg/mL, 12.7 (0.19–23.8) mcg/mL, and 23.0 (3.86–36.9) mcg/mL, respectively. For doses of 162 mg tocilizumab (patients with a body weight less than 30 kg) given every 3 weeks subcutaneously, the estimated median (range) Cmax, Ctrough, and Cmean of tocilizumab were 62.4 (39.4–121) mcg/mL, 13.4 (0.21–52.3) mcg/mL, and 35.7 (17.4–91.8) mcg/mL, respectively.

The accumulation ratios were 1.46 and 2.04 for AUC4weeks, 2.08 and 3.58 for Ctrough, and 1.32 and 1.72 for Cmax, for 162 mg given every 3 weeks (BW less than 30 kg) and 162 mg given every 2 weeks (BW at or above 30 kg) subcutaneous doses, respectively. Following subcutaneous dosing, steady state Ctrough was comparable for patients in the two body weight groups, while steady-state Cmax and Cmean were higher for patients in the less than 30 kg group compared to the group at or above 30 kg. All patients treated with TCZ SC had steady-state Ctrough at or higher than that achieved with TCZ IV across the spectrum of body weights. The average and trough concentrations in patients after subcutaneous dosing were within the range of those achieved in adult patients with RA following the subcutaneous administration of the recommended regimens.

Systemic Juvenile Idiopathic Arthritis – Intravenous and Subcutaneous Administration

The pharmacokinetics of tocilizumab (TCZ) in SJIA patients was characterized by a population pharmacokinetic analysis which included 89 patients who were treated with TCZ IV or 51 patients treated with TCZ SC.

For doses of 8 mg/kg tocilizumab (patients with a body weight at or above 30 kg) given every 2 weeks intravenously, the estimated median (range) Cmax, Ctrough, and Cmean of tocilizumab were 253 (120–404) mcg/mL, 70.7 (5.26–127) mcg/mL, and 117 (37.6–199) mcg/mL, respectively. For doses of 12 mg/kg tocilizumab (patients with a body weight less than 30 kg) given every 2 weeks intravenously, the estimated median (range) Cmax, Ctrough, and Cmean of tocilizumab were 274 (149–444) mcg/mL, 65.9 (19.0–135) mcg/mL, and 124 (60–194) mcg/mL, respectively.

The accumulation ratios were 1.95 and 2.01 for AUC4weeks, and 3.41 and 3.20 for Ctrough for 12 mg/kg (BW less than 30 kg) and 8 mg/kg (BW at or above 30 kg) intravenous doses, respectively. Accumulation data for Cmax were 1.37 and 1.42 for 12 mg/kg (BW less than 30 kg) and 8 mg/kg (BW at or above 30 kg) intravenous doses, respectively. Following every other week dosing with tocilizumab IV, steady state was reached by 8 weeks for both body weight groups. Mean estimated tocilizumab exposure parameters were similar between the two dose groups defined by body weight.

For doses of 162 mg tocilizumab (patients with a body weight at or above 30 kg) given every week subcutaneously, the estimated median (range) Cmax, Ctrough, and Cmean of tocilizumab were 89.8 (26.4–190) mcg/mL, 72.4 (19.5–158) mcg/mL, and 82.4 (23.9–169) mcg/mL, respectively. For doses of 162 mg tocilizumab (patients with a body weight less than 30 kg) given every 2 weeks subcutaneously, the estimated median (range) Cmax, Ctrough, and Cmean of tocilizumab were 127 (51.7–266) mcg/mL, 64.2 (16.6–136) mcg/mL, and 92.7 (38.5–199) mcg/mL, respectively.

The accumulation ratios were 2.27 and 4.28 for AUC4weeks, 3.21 and 4.39 for Ctrough, and 1.88 and 3.66 for Cmax, for 162 mg given every 2 weeks (BW less than 30 kg) and 162 mg given every week (BW at or above 30 kg) subcutaneous doses, respectively. Following subcutaneous dosing, steady state was reached by 12 weeks for both body weight groups. All patients treated with tocilizumab SC had steady-state Cmax lower than that achieved with tocilizumab IV across the spectrum of body weights. Trough and mean concentrations in patients after SC dosing were similar to those achieved with tocilizumab IV across body weights.

COVID-19 -Intravenous Administration

The pharmacokinetics of tocilizumab in COVID-19 patients was characterized by a population pharmacokinetic analysis of a dataset composed of 380 adult patients treated with tocilizumab 8 mg/kg intravenously (IV) in the COVACTA study [see Clinical Studies (14.11)] and another clinical study.
For one dose of 8 mg/kg tocilizumab IV, the estimated median (range) Cmax and Cday28 of tocilizumab were 151 (77.5-319) mcg/mL and 0.229 (0.00119-19.4) mcg/mL, respectively. For two doses of 8 mg/kg tocilizumab IV separated by at least 8 hours, the estimated median (range) Cmax and Cday28 of tocilizumab was 290 (152-604) mcg/mL and 7.04 (0.00474-54.8) mcg/mL, respectively. The weight-tiered dosing used in RECOVERY study, 800 mg for patients >90 kg, 600 mg for patients >65 and ≤90 kg, 400 mg for patients >40 and ≤65 kg, and 8mg/kg for patients ≤40 kg, is comparable to 8 mg/kg dosing and is expected to have similar exposure.

Absorption

Following subcutaneous dosing, the absorption half-life was around 4 days in RA and GCA patients. The bioavailability for the subcutaneous formulation was 80%.

Following subcutaneous dosing in PJIA patients, the absorption half-life was around 2 days, and the bioavailability for the subcutaneous formulation in PJIA patients was 96%.

Following subcutaneous dosing in SJIA patients, the absorption half-life was around 2 days, and the bioavailability for the SC formulation in SJIA patients was 95%.

In RA patients the median values of Tmax were 2.8 days after the tocilizumab every week dose and 4.7 days after the tocilizumab every other week dose.

In GCA patients, the median values of Tmax were 3 days after the tocilizumab every week dose and 4.5 days after the tocilizumab every other week dose.

Distribution

Following intravenous dosing, tocilizumab undergoes biphasic elimination from the circulation. In rheumatoid arthritis patients the central volume of distribution was 3.5 L and the peripheral volume of distribution was 2.9 L, resulting in a volume of distribution at steady state of 6.4 L.

In GCA patients, the central volume of distribution was 4.09 L, the peripheral volume of distribution was 3.37 L resulting in a volume of distribution at steady state of 7.46 L.

In pediatric patients with PJIA, the central volume of distribution was 1.98 L, the peripheral volume of distribution was 2.1 L, resulting in a volume of distribution at steady state of 4.08 L.

In pediatric patients with SJIA, the central volume of distribution was 1.87 L, the peripheral volume of distribution was 2.14 L resulting in a volume of distribution at steady state of 4.01 L.

In COVID-19 patients treated with one or two infusions of tocilizumab 8 mg/kg intravenously separated by 8 hours, the estimated central volume of distribution was 4.52 L, and the estimated peripheral volume of distribution was 4.23 L, resulting in a volume of distribution of 8.75 L.

Elimination

Tocilizumab is eliminated by a combination of linear clearance and nonlinear elimination. The concentration-dependent nonlinear elimination plays a major role at low tocilizumab concentrations. Once the nonlinear pathway is saturated, at higher tocilizumab concentrations, clearance is mainly determined by the linear clearance. The saturation of the nonlinear elimination leads to an increase in exposure that is more than dose-proportional. The pharmacokinetic parameters of tocilizumab do not change with time.

Population pharmacokinetic analyses in any patient population tested so far indicate no relationship between apparent clearance and the presence of anti-drug antibodies.

The linear clearance in the population pharmacokinetic analysis was estimated to be 12.5 mL per h in RA patients, 6.7 mL per h in GCA patients, 5.8 mL per h in pediatric patients with PJIA, and 5.7 mL per h in pediatric patients with SJIA. In COVID-19 patients, serum concentrations were below the limit of quantification after 35 days on average following one infusion of tocilizumab 8 mg/kg intravenously. The average linear clearance in the population pharmacokinetic analysis was estimated to be 17.6 mL per hour in patients with baseline ordinal scale category 3 (OS 3, patients requiring supplemental oxygen), 22.5 mL per hour in patients with baseline OS 4 (patients requiring high-flow oxygen or non-invasive ventilation), 29 mL per hour in patients with baseline OS 5 (patients requiring mechanical ventilation), and 35.4 mL per hour in patients with baseline OS 6 (patients requiring extracorporeal membrane oxygenation (ECMO) or mechanical ventilation and additional organ support).

Due to the dependence of total clearance on tocilizumab serum concentrations, the half-life of tocilizumab is also concentration-dependent and varies depending on the serum concentration level.

For intravenous administration in RA patients, the concentration-dependent apparent t1/2 is up to 11 days for 4 mg per kg and up to 13 days for 8 mg per kg every 4 weeks in patients with RA at steady-state. For subcutaneous administration in RA patients, the concentration-dependent apparent t1/2 is up to 13 days for 162 mg every week and 5 days for 162 mg every other week in patients with RA at steady-state.

In GCA patients at steady state, the effective t1/2 of tocilizumab varied between 18.3 and 18.9 days for 162 mg subcutaneously every week dosing regimen and between 4.2 and 7.9 days for 162 mg subcutaneously every other week dosing regimen. For intravenous administration in GCA patients, the TCZ concentration-dependent apparent t1/2 was 13.2 days following 6 mg/kg every 4 weeks.

The t1/2 of tocilizumab in children with PJIA is up to 17 days for the two body weight categories (8 mg/kg for body weight at or above 30 kg or 10 mg/kg for body weight below 30 kg) during a dosing interval at steady state. For subcutaneous administration, the t1/2 of tocilizumab in PJIA patients is up to 10 days for the two body weight categories (every other week regimen for body weight at or above 30 kg or every 3 week regimen for body weight less than 30 kg) during a dosing interval at steady state.

The t1/2 of tocilizumab intravenous in pediatric patients with SJIA is up to 16 days for the two body weight categories (8 mg/kg for body weight at or above 30 kg and 12 mg/kg for body weight below 30 kg every other week) during a dosing interval at steady-state. Following subcutaneous administration, the effective t1/2 of tocilizumab subcutaneous in SJIA patients is up to 14 days for both the body weight categories (162 mg every week for body weight at or above 30 kg and 162 mg every two weeks for body weight below 30 kg) during a dosing interval at steady state.

Specific Populations

Population pharmacokinetic analyses in adult rheumatoid arthritis patients and GCA patients showed that age, gender and race did not affect the pharmacokinetics of tocilizumab. Linear clearance was found to increase with body size. In RA patients, the body weight-based dose (8 mg per kg) resulted in approximately 86% higher exposure in patients who are greater than 100 kg in comparison to patients who are less than 60 kg. There was an inverse relationship between tocilizumab exposure and body weight for flat dose subcutaneous regimens.

In GCA patients treated with tocilizumab-SC, higher exposure was observed in patients with lower body weight. For the 162 mg every week subcutaneous dosing regimen, the steady-state Cmean was 51% higher in patients with body weight less than 60 kg compared to patients weighing between 60 to 100 kg. For the 162 mg every other week subcutaneous regimen, the steady-state Cmean was 129% higher in patients with body weight less than 60 kg compared to patients weighing between 60 to 100 kg. There is limited data for patients above 100 kg (n=7).

In COVID-19 patients, exposure following body-weight-based intravenous dosing (8 mg per kg tocilizumab up to 100 kg body weight with a maximum dose of 800 mg) was dependent on body weight and disease severity assessed by an ordinal scale (OS). Within an OS category, compared to patients with a mean body weight of 80 kg, exposure was 20% lower in patients weighing less than 60 kg. Exposure in patients weighing more than 100 kg was in the same range as exposure in patients with a mean body weight of 80 kg. For an 80 kg patient, exposure decreases as OS category increases; for each category increase, exposure decreases by 13%.

Patients with Hepatic Impairment

No formal study of the effect of hepatic impairment on the pharmacokinetics of tocilizumab was conducted.

Patients with Renal Impairment

No formal study of the effect of renal impairment on the pharmacokinetics of tocilizumab was conducted.

Most of the RA and GCA patients in the population pharmacokinetic analysis had normal renal function or mild renal impairment. Mild renal impairment (estimated creatinine clearance less than 80 mL per min and at or above 50 mL per min based on Cockcroft-Gault formula) did not impact the pharmacokinetics of tocilizumab.

Approximately one-third of the patients in the tocilizumab-SC GCA clinical trial had moderate renal impairment at baseline (estimated creatinine clearance of 30-59 mL/min). No impact on tocilizumab exposure was noted in these patients.

No dose adjustment is required in patients with mild or moderate renal impairment.

Drug Interaction Studies

In vitro data suggested that IL-6 reduced mRNA expression for several CYP450 isoenzymes including CYP1A2, CYP2B6, CYP2C9, CYP2C19, CYP2D6 and CYP3A4, and this reduced expression was reversed by co-incubation with tocilizumab at clinically relevant concentrations. Accordingly, inhibition of IL-6 signaling in RA patients treated with tocilizumab may restore CYP450 activities to higher levels than those in the absence of tocilizumab leading to increased metabolism of drugs that are CYP450 substrates. Its effect on CYP2C8 or transporters (e.g., P-gp) is unknown. This is clinically relevant for CYP450 substrates with a narrow therapeutic index, where the dose is individually adjusted. Upon initiation of TYENNE, in patients being treated with these types of medicinal products, therapeutic monitoring of the effect (e.g., warfarin) or drug concentration (e.g., cyclosporine or theophylline) should be performed and the individual dose of the medicinal product adjusted as needed.

Caution should be exercised when TYENNE is coadministered with drugs where decrease in effectiveness is undesirable, e.g., oral contraceptives (CYP3A4 substrates) [see Drug Interactions (7.2)].

Simvastatin

Simvastatin is a CYP3A4 and OATP1B1 substrate. In 12 RA patients not treated with tocilizumab, receiving 40 mg simvastatin, exposures of simvastatin and its metabolite, simvastatin acid, was 4- to 10-fold and 2-fold higher, respectively, than the exposures observed in healthy subjects. One week following administration of a single infusion of tocilizumab (10 mg per kg), exposure of simvastatin and simvastatin acid decreased by 57% and 39%, respectively, to exposures that were similar or slightly higher than those observed in healthy subjects. Exposures of simvastatin and simvastatin acid increased upon withdrawal of tocilizumab in RA patients. Selection of a particular dose of simvastatin in RA patients should take into account the potentially lower exposures that may result after initiation of TYENNE (due to normalization of CYP3A4) or higher exposures after discontinuation of TYENNE.

Omeprazole

Omeprazole is a CYP2C19 and CYP3A4 substrate. In RA patients receiving 10 mg omeprazole, exposure to omeprazole was approximately 2 fold higher than that observed in healthy subjects. In RA patients receiving 10 mg omeprazole, before and one week after tocilizumab infusion (8 mg per kg), the omeprazole AUCinf decreased by 12% for poor (N=5) and intermediate metabolizers (N=5) and by 28% for extensive metabolizers (N=8) and were slightly higher than those observed in healthy subjects.

Dextromethorphan

Dextromethorphan is a CYP2D6 and CYP3A4 substrate. In 13 RA patients receiving 30 mg dextromethorphan, exposure to dextromethorphan was comparable to that in healthy subjects. However, exposure to its metabolite, dextrorphan (a CYP3A4 substrate), was a fraction of that observed in healthy subjects. One week following administration of a single infusion of tocilizumab (8 mg per kg), dextromethorphan exposure was decreased by approximately 5%. However, a larger decrease (29%) in dextrorphan levels was noted after tocilizumab infusion.

13 NONCLINICAL TOXICOLOGY

13.1 Carcinogenesis, Mutagenesis, Impairment of Fertility

No long-term animal studies have been performed to establish the carcinogenicity potential of tocilizumab products. Literature indicates that the IL-6 pathway can mediate anti-tumor responses by promoting increased immune cell surveillance of the tumor microenvironment. However, available published evidence also supports that IL-6 signaling through the IL-6 receptor may be involved in pathways that lead to tumorigenesis. The malignancy risk in humans from an antibody that disrupts signaling through the IL-6 receptor, such as tocilizumab, is presently unknown.

Fertility and reproductive performance were unaffected in male and female mice that received a murine analogue of tocilizumab administered by the intravenous route at a dose of 50 mg/kg every three days.

14 CLINICAL STUDIES

14.1 Rheumatoid Arthritis – Intravenous Administration

The efficacy and safety of intravenously administered tocilizumab was assessed in five randomized, double-blind, multicenter studies in patients greater than 18 years with active rheumatoid arthritis diagnosed according to American College of Rheumatology (ACR) criteria. Patients had at least 8 tender and 6 swollen joints at baseline. Tocilizumab was given intravenously every 4 weeks as monotherapy (Study I), in combination with methotrexate (MTX) (Studies II and III) or other disease-modifying anti-rheumatic drugs (DMARDs) (Study IV) in patients with an inadequate response to those drugs, or in combination with MTX in patients with an inadequate response to TNF antagonists (Study V).

Study I (NCT00109408) evaluated patients with moderate to severe active rheumatoid arthritis who had not been treated with MTX within 24 weeks prior to randomization, or who had not discontinued previous methotrexate treatment as a result of clinically important toxic effects or lack of response. In this study, 67% of patients were MTX-naïve, and over 40% of patients had rheumatoid arthritis less than 2 years. Patients received tocilizumab 8 mg per kg monotherapy or MTX alone (dose titrated over 8 weeks from 7.5 mg to a maximum of 20 mg weekly). The primary endpoint was the proportion of tocilizumab patients who achieved an ACR 20 response at Week 24.

Study II (NCT00106535) was a 104-week study with an optional 156-week extension phase that evaluated patients with moderate to severe active rheumatoid arthritis who had an inadequate clinical response to MTX. Patients received tocilizumab 8 mg per kg, tocilizumab 4 mg per kg, or placebo every four weeks, in combination with MTX (10 to 25 mg weekly). Upon completion of 52-weeks, patients received open-label treatment with tocilizumab 8 mg per kg through 104 weeks or they had the option to continue their double-blind treatment if they maintained a greater than 70% improvement in swollen/tender joint count. Two pre-specified interim analyses at week 24 and week 52 were conducted. The primary endpoint at week 24 was the proportion of patients who achieved an ACR 20 response. At weeks 52 and 104, the primary endpoints were change from baseline in modified total Sharp-Genant score and the area under the curve (AUC) of the change from baseline in HAQ-DI score.

Study III (NCT00106548) evaluated patients with moderate to severe active rheumatoid arthritis who had an inadequate clinical response to MTX. Patients received tocilizumab 8 mg per kg, tocilizumab 4 mg per kg, or placebo every four weeks, in combination with MTX (10 to 25 mg weekly). The primary endpoint was the proportion of patients who achieved an ACR 20 response at week 24.

Study IV (NCT00106574) evaluated patients who had an inadequate response to their existing therapy, including one or more DMARDs. Patients received tocilizumab 8 mg per kg or placebo every four weeks, in combination with the stable DMARDs. The primary endpoint was the proportion of patients who achieved an ACR 20 response at week 24.

Study V (NCT00106522) evaluated patients with moderate to severe active rheumatoid arthritis who had an inadequate clinical response or were intolerant to one or more TNF antagonist therapies. The TNF antagonist therapy was discontinued prior to randomization. Patients received tocilizumab 8 mg per kg, tocilizumab 4 mg per kg, or placebo every four weeks, in combination with MTX (10 to 25 mg weekly). The primary endpoint was the proportion of patients who achieved an ACR 20 response at week 24.

Clinical Response

The percentages of intravenous tocilizumab-treated patients achieving ACR 20, 50 and 70 responses are shown in Table 4. In all intravenous studies, patients treated with 8 mg per kg tocilizumab had higher ACR 20, ACR 50, and ACR 70 response rates versus MTX- or placebo-treated patients at week 24.

During the 24 week controlled portions of Studies I to V, patients treated with tocilizumab at a dose of 4 mg per kg in patients with inadequate response to DMARDs or TNF antagonist therapy had lower response rates compared to patients treated with tocilizumab 8 mg per kg.

Table 4 Clinical Response at Weeks 24 and 52 in Active and Placebo Controlled Trials of Intravenous Tocilizumab (Percent of Patients)
Percent of Patients
 | Study I |  | Study II |  |  | Study III |  |  | Study IV |  | Study V
Response Rate | MTX | Tocilizumab 8 mg per kg | Placebo + MTX | Tocilizumab 4 mg per kg + MTX | Tocilizumab 8 mg per kg + MTX | Placebo + MTX | Tocilizumab 4 mg per kg + MTX | Tocilizumab 8 mg per kg + MTX | Placebo + DMARDs | Tocilizumab 8 mg per kg + DMARDs | Placebo + MTX | Tocilizumab 4 mg per kg + MTX | Tocilizumab 8 mg per kg + MTX
Response Rate | N=284 | N=286 | N=393 | N=399 | N=398 | N=204 | N=213 | N=205 | N=413 | N=803 | N=158 | N=161 | N=170
Response Rate |  | (95% CI)a |  | (95% CI)a | (95% CI)a |  | (95% CI)a | (95% CI)a |  | (95% CI)a |  | (95% CI)a | (95% CI)a
ACR 20
Week 24 | 53% | 70% | 27% | 51% | 56% | 27% | 48% | 59% | 24% | 61% | 10% | 30% | 50%
 |  | (0.11, 0.27) |  | (0.17, 0.29) | (0.23, 0.35) |  | (0.15, 0.32) | (0.23, 0.41) |  | (0.30, 0.40) |  | (0.15, 0.36) | (0.36, 0.56)
Week 52 | N/A | N/A | 25% | 47% | 56% | N/A | N/A | N/A | N/A | N/A | N/A | N/A | N/A
 |  |  |  | (0.15, 0.28) | (0.25, 0.38)
ACR 50
Week 24 | 34% | 44% | 10% | 25% | 32% | 11% | 32% | 44% | 9% | 38% | 4% | 17% | 29%
 |  | (0.04, 0.20) |  | (0.09, 0.20) | (0.16, 0.28) |  | (0.13, 0.29) | (0.25, 0.41) |  | (0.23, 0.33) |  | (0.05, 0.25) | (0.21, 0.41)
Week 52 | N/A | N/A | 10% | 29% | 36% | N/A | N/A | N/A | N/A | N/A | N/A | N/A | N/A
 |  |  |  | (0.14, 0.25) | (0.21, 0.32)
ACR 70
Week 24 | 15% | 28% | 2% | 11% | 13% | 2% | 12% | 22% | 3% | 21% | 1% | 5% | 12%
 |  | (0.07, 0.22) |  | (0.03, 0.13) | (0.05, 0.15) |  | (0.04, 0.18) | (0.12, 0.27) |  | (0.13, 0.21) |  | (-0.06, 0.14) | (0.03, 0.22)
Week 52 | N/A | N/A | 4% | 16% | 20% | N/A | N/A | N/A | N/A | N/A
 |  |  |  | (0.08, 0.17) | (0.12, 0.21) |  |  |  |  |  | N/A | N/A | N/A
Major Clinical Responses b
Week 52 | N/A | N/A | 1% | 4% | 7% | N/A | N/A | N/A | N/A | N/A | N/A | N/A | N/A
 |  |  |  | (0.01, 0.06) | (0.03, 0.09)
a CI: 95% confidence interval of the weighted difference to placebo adjusted for site (and disease duration for Study I only)
b Major clinical response is defined as achieving an ACR 70 response for a continuous 24 week period

In study II, a greater proportion of patients treated with 4 mg per kg and 8 mg per kg tocilizumab + MTX achieved a low level of disease activity as measured by a DAS 28-ESR less than 2.6 compared with placebo+ MTX treated patients at week 52. The proportion of tocilizumab-treated patients achieving DAS 28-ESR less than 2.6, and the number of residual active joints in these responders in Study II are shown in Table 5.

Table 5 Proportion of Patients with DAS28-ESR Less Than 2.6 with Number of Residual Active Joints in Trials of Intravenous Tocilizumab
Study II
 | Placebo + MTX N = 393 | Tocilizumab 4 mg per kg + MTX N = 399 | Tocilizumab 8 mg per kg + MTX N = 398
DAS28-ESR less than 2.6
Proportion of responders at week 52 (n) 95% confidence interval | 3% (12) | 18% (70) 0.10, 0.19 | 32% (127) 0.24, 0.34
Of responders, proportion with 0 active joints (n) | 33% (4) | 27% (19) | 21% (27)
Of responders, proportion with 1 active joint (n) | 8% (1) | 19% (13) | 13% (16)
Of responders, proportion with 2 active joints (n) | 25% (3) | 13% (9) | 20% (25)
Of responders, proportion with 3 or more active joints (n) | 33% (4) | 41% (29) | 47% (59)
*n denotes numerator of all the percentage. Denominator is the intent-to-treat population. Not all patients received DAS28 assessments at Week 52.

The results of the components of the ACR response criteria for Studies III and V are shown in Table 6. Similar results to Study III were observed in Studies I, II and IV.

Table 6 Components of ACR Response at Week 24 in Trials of Intravenous Tocilizumab
 | Study III |  |  |  |  |  | Study V
 | Tocilizumab 4 mg per kg + MTX N=213 |  | Tocilizumab 8 mg per kg + MTX N=205 |  | Placebo + MTX N=204 |  | Tocilizumab 4 mg per kg + MTX N=161 |  | Tocilizumab 8 mg per kg + MTX N=170 |  | Placebo + MTX N=158
Component (mean) | Baseline | Week 24a | Baseline | Week 24 a | Baseline | Week 24 | Baseline | Week 24 a | Baseline | Week 24 a | Baseline | Week 24
Number of | 33 | 19 | 32 | 14.5 | 33 | 25 | 31 | 21 | 32 | 17 | 30 | 30
tender joints | 33 | -7.0 | 32 | -9.6 | 33 | 25 | 31 | -10.8 | 32 | -15.1 | 30 | 30
(0-68) | 33 | (-10.0, -4.1) | 32 | (-12.6, -6.7) | 33 | 25 | 31 | (-14.6, -7.1) | 32 | (-18.8, -11.4) | 30 | 30
Number of | 20 | 10 | 19.5 | 8 | 21 | 15 | 19.5 | 13 | 19 | 11 | 19 | 18
swollen | 20 | -4.2 | 19.5 | -6.2 | 21 | 15 | 19.5 | -6.2 | 19 | -7.2 | 19 | 18
joints (0-66) | 20 | (-6.1, -2.3) | 19.5 | (-8.1, -4.2) | 21 | 15 | 19.5 | (-9.0, -3.5) | 19 | (-9.9, -4.5) | 19 | 18
Pain b | 61 | 33 -11.0 | 60 | 30 -15.8 | 57 | 43 | 63.5 | 43 -12.4 | 65 | 33 -23.9 | 64 | 48
Pain b | 61 | (-17.0, -5.0) | 60 | (-21.7, -9.9) | 57 | 43 | 63.5 | (-22.1, -2.1) | 65 | (-33.7, -14.1) | 64 | 48
Patient | 66 | 34 | 65 | 31 | 64 | 45 | 70 | 46 | 70 | 36 | 71 | 51
global | 66 | -10.9 | 65 | -14.9 | 64 | 45 | 70 | -10.0 | 70 | -17.4 | 71 | 51
Assessment b | 66 | (-17.1, -4.8) | 65 | (-20.9, -8.9) | 64 | 45 | 70 | (-20.3, 0.3) | 70 | (-27.8, -7.0) | 71 | 51
Physician | 64 | 26 | 64 | 23 | 64 | 32 | 66.5 | 39 | 66 | 28 | 67.5 | 43
global | 64 | -5.6 | 64 | -9.0 | 64 | 32 | 66.5 | -10.5 | 66 | -18.2 | 67.5 | 43
Assessment b | 64 | (-10.5, -0.8) | 64 | (-13.8, -4.2) | 64 | 32 | 66.5 | (-18.6, -2.5) | 66 | (-26.3, -10.0) | 67.5 | 43
Disability | 1.64 | 1.01 | 1.55 | 0.96 | 1.55 | 1.21 | 1.67 | 1.39 | 1.75 | 1.34 | 1.70 | 1.58
index | 1.64 | -0.18 | 1.55 | -0.21 | 1.55 | 1.21 | 1.67 | -0.25 | 1.75 | -0.34 | 1.70 | 1.58
(HAQ)c | 1.64 | (-0.34, -0.02) | 1.55 | (-0.37, -0.05) | 1.55 | 1.21 | 1.67 | (-0.42, -0.09) | 1.75 | (-0.51, -0.17) | 1.70 | 1.58
CRP (mg per | 2.79 | 1.17; -1.30 | 2.61 | 0.25 -2.156 | 2.36 | 1.89 | 3.11 | 1.77; -1.34 | 2.80 | 0.28; -2.52 | 3.705 | 3.06
dL) | 2.79 | 1.17; -1.30 | 2.61 | 0.25 -2.156 | 2.36 | 1.89 | 3.11 | 1.77; -1.34 | 2.80 | 0.28; -2.52 | 3.705 | 3.06
dL) | (-2.0, -0.59) | 1.17; -1.30 | (-2.86, -1.46) | 0.25 -2.156 | (-2.5, -0.15) | 1.89 | 3.11 | 1.77; -1.34 | (-3.72, -1.32) | 0.28; -2.52 | 3.705 | 3.06
a Data shown is mean at week 24, difference in adjusted mean change from baseline compared with placebo + MTX at week 24 and 95% confidence interval for that difference
b Visual analog scale: 0 = best, 100 = worst
c Health Assessment Questionnaire: 0 = best, 3 = worst; 20 questions; 8 categories: dressing and grooming, arising, eating, walking, hygiene, reach, grip, and activities

The percent of ACR 20 responders by visit for Study III is shown in Figure 1. Similar response curves were observed in studies I, II, IV, and V.

Figure 1 Percent of ACR 20 Responders by Visit for Study III (Inadequate Response to MTX)*

*The same patients may not have responded at each timepoint.

Radiographic Response

In Study II, structural joint damage was assessed radiographically and expressed as change in total Sharp-Genant score and its components, the erosion score and joint space narrowing score. Radiographs of hands/wrists and forefeet were obtained at baseline, 24 weeks, 52 weeks, and 104 weeks and scored by readers unaware of treatments group and visit number. The results from baseline to week 52 are shown in Table 7. Tocilizumab 4 mg per kg slowed (less than 75% inhibition compared to the control group) and tocilizumab 8 mg per kg inhibited (at least 75% inhibition compared to the control group) the progression of structural damage compared to placebo plus MTX at week 52.

Table 7 Mean Radiographic Change from Baseline to Week 52 in Study II
 | Placebo + MTX | Tocilizumab 4 mg per kg + MTX | Tocilizumab 8 mg per kg + MTX
 | N=294 | N=343 | N=353
Week 52*
Total Sharp-Genant Score, Mean (SD) | 1.17 (3.14) | 0.33 (1.30) | 0.25 (0.98)
Adjusted Mean difference** (95%CI) |  | -0.83 (-1.13, -0.52) | -0.90 (-1.20, -0.59)
Erosion Score, Mean (SD) | 0.76 (2.14) | 0.20 (0.83) | 0.15 (0.77)
Adjusted Mean difference** (95%CI) |  | -0.55 (-0.76, -0.34) | -0.60 (-0.80, -0.39)
Joint Space Narrowing Score, Mean (SD) | 0.41 (1.71) | 0.13 (0.72) | 0.10 (0.49)
Adjusted Mean difference** (95%CI) |  | -0.28 (-0.44, -0.11) | -0.30 (-0.46, -0.14)
* Week 52 analysis employs linearly extrapolated data for patients after escape, withdrawal, or loss to follow up.
** Difference between the adjusted means (tocilizumab + MTX – Placebo + MTX) SD = standard deviation

The mean change from baseline to week 104 in Total Sharp-Genant Score for the tocilizumab 4 mg per kg groups was 0.47 (SD = 1.47) and for the 8 mg per kg groups was 0.34 (SD = 1.24). By the week 104, most patients in the control (placebo + MTX) group had crossed over to active treatment, and results are therefore not included for comparison. Patients in the active groups may have crossed over to the alternate active dose group, and results are reported per original randomized dose group.

In the placebo group, 66% of patients experienced no radiographic progression (Total Sharp-Genant Score change ≤ 0) at week 52 compared to 78% and 83% in the tocilizumab 4 mg per kg and 8 mg per kg, respectively. Following 104 weeks of treatment, 75% and 83% of patients initially randomized to tocilizumab 4 mg per kg and 8 mg per kg, respectively, experienced no progression of structural damage compared to 66% of placebo treated patients.

Health Related Outcomes

In Study II, physical function and disability were assessed using the Health Assessment Questionnaire Disability Index (HAQ-DI). Both dosing groups of tocilizumab demonstrated a greater improvement compared to the placebo group in the AUC of change from baseline in the HAQ-DI through week 52. The mean change from baseline to week 52 in HAQ-DI was 0.6, 0.5, and 0.4 for tocilizumab 8 mg per kg, tocilizumab 4 mg per kg, and placebo treatment groups, respectively. Sixty-three percent (63%) and sixty percent (60%) of patients in the tocilizumab 8 mg per kg and tocilizumab 4 mg per kg treatment groups, respectively, achieved a clinically relevant improvement in HAQ-DI (change from baseline of ≥ 0.3 units) at week 52 compared to 53% in the placebo treatment group.

Other Health-Related Outcomes

General health status was assessed by the Short Form Health Survey (SF-36) in Studies I – V. Patients receiving tocilizumab demonstrated greater improvement from baseline compared to placebo in the Physical Component Summary (PCS), Mental Component Summary (MCS), and in all 8 domains of the SF-36.

Cardiovascular Outcomes

Study WA25204 (NCT01331837) was a randomized, open-label (sponsor-blinded), 2-arm parallel-group, multicenter, non-inferiority, cardiovascular (CV) outcomes trial in patients with a diagnosis of moderate to severe RA. This CV safety study was designed to exclude a moderate increase in CV risk in patients treated with tocilizumab compared with a TNF inhibitor standard of care (etanercept).

The study included 3,080 seropositive RA patients with active disease and an inadequate response to non- biologic disease-modifying anti-rheumatic drugs, who were aged ≥50 years with at least one additional CV risk factor beyond RA. Patients were randomized 1:1 to IV tocilizumab 8 mg/kg Q4W or SC etanercept 50 mg QW and followed for an average of 3.2 years. The primary endpoint was the comparison of the time-to-first occurrence of any component of a composite of major adverse CV events (MACE; non-fatal myocardial infarction, non-fatal stroke, or CV death), with the final intent-to-treat analysis based on a total of 161 confirmed CV events (83/1538 [5.4%] for tocilizumab; 78/1542 [5.1%] for etanercept) reviewed by an independent and blinded adjudication committee.

Non-inferiority of tocilizumab to etanercept for cardiovascular risk was determined by excluding >80% relative increase in the risk of MACE. The estimated hazard ratio (HR) for the risk of MACE comparing tocilizumab to etanercept was 1.05; 95% CI (0.77, 1.43).

14.2 Rheumatoid Arthritis – Subcutaneous Administration

The efficacy and safety of subcutaneously administered tocilizumab was assessed in two double-blind, controlled, multicenter studies in patients with active RA. One study, SC-I (NCT01194414), was a non-inferiority study that compared the efficacy and safety of tocilizumab 162 mg administered every week subcutaneously to 8 mg per kg intravenously every four weeks. The second study, SC-II (NCT01232569), was a placebo-controlled superiority study that evaluated the safety and efficacy of tocilizumab 162 mg administered every other week subcutaneously to placebo. Both SC-I and SC-II required patients to be >18 years of age with moderate to severe active rheumatoid arthritis diagnosed according to ACR criteria who had at least 4 tender and 4 swollen joints at baseline (SC-I) or at least 8 tender and 6 swollen joints at baseline (SC-II), and an inadequate response to their existing DMARD therapy, where approximately 20% also had a history of inadequate response to at least one TNF inhibitor. All patients in both SC studies received background non-biologic DMARD(s).

In SC-I, 1262 patients were randomized 1:1 to receive tocilizumab-SC 162 mg every week or intravenous tocilizumab 8 mg/kg every four weeks in combination with DMARD(s). In SC-II, 656 patients were randomized 2:1 to tocilizumab-SC 162 mg every other week or placebo, in combination with DMARD(s). The primary endpoint in both studies was the proportion of patients who achieved an ACR20 response at Week 24.

The clinical response to 24 weeks of tocilizumab-SC therapy is shown in Table 8. In SC-I, the primary outcome measure was ACR20 at Week 24. The pre-specified non-inferiority margin was a treatment difference of 12%. The study demonstrated non-inferiority of tocilizumab with respect to ACR20 at Week 24; ACR50, ACR70, and DAS28 responses are also shown in Table 8. In SC-II, a greater portion of patients treated with tocilizumab 162 mg subcutaneously every other week achieved ACR20, ACR50, and ACR70 responses compared to placebo-treated patients (Table 8). Further, a greater proportion of patients treated with tocilizumab 162 mg subcutaneously every other week achieved a low level of disease activity as measured by a DAS28-ESR less than 2.6 at Week 24 compared to those treated with placebo (Table 8).

Table 8 Clinical Response at Week 24 in Trials of Subcutaneous Tocilizumab (Percent of Patients)
 | SC-Ia |  | SC-IIb
 | TCZ SC 162 mg every week + DMARD | TCZ IV 8mg/kg + DMARD | TCZ SC 162 mg every other week + DMARD | Placebo + DMARD
 | N=558 | N=537 | N=437 | N=219
ACR20
Week 24 | 69% | 73.4% | 61% | 32%
Weighted difference (95% CI) | -4% (-9.2, 1.2) |  | 30% (22.0, 37.0)
ACR50
Week 24 | 47% | 49% | 40% | 12%
Weighted difference (95% CI) | -2% (-7.5, 4.0) |  | 28% (21.5, 34.4)
ACR70
Week 24 | 24% | 28% | 20% | 5%
Weighted difference (95% CI) | -4% (-9.0, 1.3) |  | 15% (9.8, 19.9)
Change in DAS28 [Adjusted mean]
Week 24 | -3.5 | -3.5 | -3.1 | -1.7
Adjusted mean difference (95% CI) | 0 (-0.2, 0.1) |  | -1.4 (-1.7; -1.1)
DAS28 < 2.6
Week 24 | 38.4% | 36.9% | 32.0% | 4.0%
Weighted difference (95% CI) | 0.9 (-5.0, 6.8) |  | 28.6 (22.0, 35.2)
TCZ = tocilizumab
a Per Protocol Population
b Intent To Treat Population

The results of the components of the ACR response criteria and the percent of ACR20 responders by visit for tocilizumab-SC in Studies SC-I and SC-II were consistent with those observed for tocilizumab-IV.

Radiographic Response

In study SC-II, the progression of structural joint damage was assessed radiographically and expressed as a change from baseline in the van der Heijde modified total Sharp score (mTSS). At week 24, significantly less radiographic progression was observed in patients receiving tocilizumab-SC every other week plus DMARD(s) compared to placebo plus DMARD(s); mean change from baseline in mTSS of 0.62 vs. 1.23, respectively, with an adjusted mean difference of -0.60 (-1.1, -0.1). These results are consistent with those observed in patients treated with intravenous tocilizumab.

Health Related Outcomes

In studies SC-I and SC-II, the mean decrease from baseline to week 24 in HAQ-DI was 0.6, 0.6, 0.4 and 0.3, and the proportion of patients who achieved a clinically relevant improvement in HAQ-DI (change from baseline of ≥ 0.3 units) was 65%, 67%, 58% and 47%, for the subcutaneous every week, intravenous 8 mg/kg, subcutaneous every other week, and placebo treatment groups, respectively.

Other Health-Related Outcomes

General health status was assessed by the SF-36 in Studies SC-I and SC-II. In Study SC-II, patients receiving tocilizumab every other week demonstrated greater improvement from baseline compared to placebo in the PCS, MCS, and in all 8 domains of the SF-36. In Study SC-I, improvements in these scores were similar between tocilizumab-SC every week and tocilizumab-IV 8 mg/kg.

14.3 Giant Cell Arteritis – Subcutaneous Administration

The efficacy and safety of subcutaneously administered tocilizumab was assessed in a single, randomized, double-blind, multicenter study in patients with active GCA. In Study WA28119 (NCT01791153), 251 screened patients with new-onset or relapsing GCA were randomized to one of four treatment arms. Two subcutaneous doses of tocilizumab (162 mg every week and 162 mg every other week) were compared to two different placebo control groups (pre-specified prednisone-taper regimen over 26 weeks and 52 weeks) randomized 2:1:1:1. The study consisted of a 52-week blinded period, followed by a 104-week open-label extension.

All patients received background glucocorticoid (prednisone) therapy. Each of the tocilizumab-treated groups and one of the placebo-treated groups followed a pre-specified prednisone-taper regimen with the aim to reach 0 mg by 26 weeks, while the second placebo-treated group followed a pre-specified prednisone-taper regimen with the aim to reach 0 mg by 52 weeks designed to be more in keeping with standard practice.

The primary efficacy endpoint was the proportion of patients achieving sustained remission from Week 12 through Week 52. Sustained remission was defined by a patient attaining a sustained (1) absence of GCA signs and symptoms from Week 12 through Week 52, (2) normalization of erythrocyte sedimentation rate (ESR) (to < 30 mm/hr without an elevation to ≥ 30 mm/hr attributable to GCA) from Week 12 through Week 52, (3) normalization of C-reactive protein (CRP) (to < 1 mg/dL, with an absence of successive elevations to ≥ 1mg/dL) from Week 12 through Week 52, and (4) successful adherence to the prednisone taper defined by not more than 100 mg of excess prednisone from Week 12 through Week 52. Tocilizumab 162 mg weekly and 162 mg every other week + 26 weeks prednisone taper both showed superiority in achieving sustained remission from Week 12 through Week 52 compared with placebo + 26 weeks prednisone taper (Table 9). Both tocilizumab treatment arms also showed superiority compared to the placebo + 52 weeks prednisone taper (Table 9).

Table 9 Efficacy Results from Study WA28119
 | PBO + 26 weeks prednisone taper N=50 | PBO + 52 weeks prednisone taper N=51 | TCZ 162mg SC QW + 26 weeks prednisone taper N=100 | TCZ 162 mg SC Q2W + 26 weeks prednisone taper N=49
Sustained remission a
Responders, n (%) | 7 (14.0%) | 9 (17.6%) | 56 (56.0%) | 26 (53.1%)
Unadjusted difference in proportions vs PBO + 26 weeks taper (99.5% CI) | N/A | N/A | 42.0% (18.0, 66.0) | 39.1% (12.5, 65.7)
Unadjusted difference in proportions vs PBO + 52 weeks taper (99.5% CI) | N/A | N/A | 38.4% (14.4, 62.3) | 35.4% (8.6, 62.2)
Components of Sustained Remission
Sustained absence of GCA signs and symptomsb, n (%) Sustained ESR<30 mm/hrc, n (%) Sustained CRP normalizationd, n (%) Successful prednisone taperinge, n (%) | 20 (40.0%) 20 (40.0%) 17 (34.0%) 10 (20.0%) | 23 (45.1%) 22 (43.1%) 13 (25.5%) 20 (39.2%) | 69 (69.0%) 83 (83.0%) 72 (72.0%) 60 (60.0%) | 28 (57.1%) 37 (75.5%) 34 (69.4%) 28 (57.1%)
a Sustained remission was achieved by a patient meeting all of the following components: absence of GCA signs and symptomsb, normalization of ESRc, normalization of CRPd and adherence to the prednisone taper regimene.
b Patients who did not have any signs or symptoms of GCA recorded from Week 12 up to Week 52.
c Patients who did not have an elevated ESR ≥30 mm/hr which was classified as attributed to GCA from Week 12 up to Week 52.
d Patients who did not have two or more consecutive CRP records of ≥ 1mg/dL from Week 12 up to Week 52.
e Patients who did not enter escape therapy and received ≤ 100mg of additional concomitant prednisone from Week 12 up to Week 52.

Patients not completing the study to week 52 were classified as non-responders in the primary and key secondary analysis: PBO+26: 6 (12.0%), PBO+52: 5 (9.8%), TCZ QW: 15 (15.0%), TCZ Q2W: 9 (18.4%).

CRP = C-reactive protein

ESR = erythrocyte sedimentation rate

PBO = placebo

Q2W = every other week dose

QW = every week dose

TCZ = tocilizumab

The estimated annual cumulative prednisone dose was lower in the two tocilizumab dose groups (medians of 1887 mg and 2207 mg on tocilizumab QW and Q2W, respectively) relative to the placebo arms (medians of 3804 mg and 3902 mg on placebo + 26 weeks prednisone and placebo + 52 weeks prednisone taper, respectively).

14.4 Giant Cell Arteritis – Intravenous Administration

Intravenously administered tocilizumab in patients with GCA was assessed in WP41152 (NCT03923738), an open-label PK-PD and safety study to determine the appropriate intravenous dose of tocilizumab that achieved comparable PK-PD profiles to the tocilizumab-SC regimen.

At enrollment, all patients (n=24) were in remission on tocilizumab-IV. In Period 1, all patients received open label tocilizumab-IV 7 mg/kg every 4 weeks for 20 weeks. Patients who completed Period 1 and remained in remission (n=22) were eligible to enter Period 2, and received open-label tocilizumab-IV 6 mg/kg every 4 weeks for 20 weeks.

The efficacy of intravenous tocilizumab 6 mg/kg in adult patients with GCA is based on pharmacokinetic exposure and extrapolation to the efficacy established for subcutaneous tocilizumab in patients with GCA [see Clinical Pharmacology (12.3) and Clinical Studies (14.3)].

14.5 Polyarticular Juvenile Idiopathic Arthritis – Intravenous Administration

The efficacy of tocilizumab was assessed in a three-part study, WA19977 (NCT00988221), including an open- label extension in children 2 to 17 years of age with active polyarticular juvenile idiopathic arthritis (PJIA), who had an inadequate response to methotrexate or inability to tolerate methotrexate. Patients had at least 6 months of active disease (mean disease duration of 4.2 ± 3.7 years), with at least five joints with active arthritis (swollen or limitation of movement accompanied by pain and/or tenderness) and/or at least 3 active joints having limitation of motion (mean, 20 ± 14 active joints). The patients treated had subtypes of JIA that at disease onset included Rheumatoid Factor Positive or Negative Polyarticular JIA, or Extended Oligoarticular JIA. Treatment with a stable dose of methotrexate was permitted but was not required during the study. Concurrent use of disease modifying antirheumatic drugs (DMARDs), other than methotrexate, or other biologics (e.g., TNF antagonists or T cell costimulation modulator) were not permitted in the study.

Part I consisted of a 16-week active tocilizumab treatment lead-in period (n=188) followed by Part II, a 24-week randomized double-blind placebo-controlled withdrawal period, followed by Part III, a 64-week open-label period. Eligible patients weighing at or above 30 kg received tocilizumab at 8 mg/kg intravenously once every four weeks. Patients weighing less than 30 kg were randomized 1:1 to receive either tocilizumab 8 mg/kg or 10 mg/kg intravenously every four weeks. At the conclusion of the open-label Part I, 91% of patients taking background MTX in addition to tocilizumab and 83% of patients on tocilizumab monotherapy achieved an ACR 30 response at week 16 compared to baseline and entered the blinded withdrawal period (Part II) of the study.

The proportions of patients with JIA ACR 50/70 responses in Part I were 84.0%, and 64%, respectively for patients taking background MTX in addition to tocilizumab and 80% and 55% respectively for patients on tocilizumab monotherapy.

In Part II, patients (ITT, n=163) were randomized to tocilizumab (same dose received in Part I) or placebo in a 1:1 ratio that was stratified by concurrent methotrexate use and concurrent corticosteroid use. Each patient continued in Part II of the study until Week 40 or until the patient satisfied JIA ACR 30 flare criteria (relative to Week 16) and qualified for escape.

The primary endpoint was the proportion of patients with a JIA ACR 30 flare at week 40 relative to week 16. JIA ACR 30 flare was defined as 3 or more of the 6 core outcome variables worsening by at least 30% with no more than 1 of the remaining variables improving by more than 30% relative to Week 16.

Tocilizumab treated patients experienced significantly fewer disease flares compared to placebo-treated patients (26% [21/82] versus 48% [39/81]; adjusted difference in proportions -21%, 95% CI: -35%, -8%).

During the withdrawal phase (Part II), more patients treated with tocilizumab showed JIA ACR 30/50/70 responses at Week 40 compared to patients withdrawn to placebo.

14.6 Polyarticular Juvenile Idiopathic Arthritis – Subcutaneous Administration

Subcutaneously administered tocilizumab in pediatric patients with polyarticular juvenile idiopathic arthritis (PJIA) was assessed in WA28117 (NCT01904279), a 52-week, open-label, multicenter, PK-PD and safety study to determine the appropriate subcutaneous dose of tocilizumab that achieved comparable PK/PD profiles to the tocilizumab-IV regimen. PJIA patients aged 1 to 17 years with an inadequate response or inability to tolerate MTX, including patients with well-controlled disease on treatment with tocilizumab-IV and tocilizumab-naïve patients with active disease, were treated with subcutaneous tocilizumab based on body weight.

Patients weighing at or above 30 kg (n = 25) were treated with 162 mg of tocilizumab-SC every 2 weeks and patients weighing less than 30 kg (n = 27) received 162 mg of tocilizumab-SC every 3 weeks for 52 weeks. Of these 52 patients, 37 (71%) were naïve to tocilizumab and 15 (29%) had been receiving tocilizumab-IV and switched to tocilizumab-SC at baseline.

The efficacy of subcutaneous tocilizumab in children 2 to 17 years of age is based on pharmacokinetic exposure and extrapolation of the established efficacy of intravenous tocilizumab in polyarticular JIA patients and subcutaneous tocilizumab in patients with RA [see Clinical Pharmacology (12.3) and Clinical Studies (14.2 and 14.6)].

14.7 Systemic Juvenile Idiopathic Arthritis - Intravenous Administration

The efficacy of tocilizumab for the treatment of active SJIA was assessed in WA18221 (NCT00642460), a 12-week randomized, double blind, placebo-controlled, parallel group, 2-arm study. Patients treated with or without MTX, were randomized (tocilizumab:placebo = 2:1) to one of two treatment groups: 75 patients received tocilizumab infusions every two weeks at either 8 mg per kg for patients at or above 30 kg or 12 mg per kg for patients less than 30 kg and 37 were randomized to receive placebo infusions every two weeks. Corticosteroid tapering could occur from week six for patients who achieved a JIA ACR 70 response. After 12 weeks or at the time of escape, due to disease worsening, patients were treated with tocilizumab in the open-label extension phase at weight appropriate dosing.

The primary endpoint was the proportion of patients with at least 30% improvement in JIA ACR core set (JIA ACR 30 response) at Week 12 and absence of fever (no temperature at or above 37.5°C in the preceding 7 days). JIA ACR (American College of Rheumatology) responses are defined as the percentage improvement (e.g., 30%, 50%, 70%) in 3 of any 6 core outcome variables compared to baseline, with worsening in no more than 1 of the remaining variables by 30% or more.

Core outcome variables consist of physician global assessment, parent per patient global assessment, number of joints with active arthritis, number of joints with limitation of movement, erythrocyte sedimentation rate (ESR), and functional ability (childhood health assessment questionnaire-CHAQ).

Primary endpoint result and JIA ACR response rates at Week 12 are shown in Table 10.

Table 10 Efficacy Findings at Week 12
 | Tocilizumab N=75 | Placebo N=37
Primary Endpoint: JIA ACR 30 response + absence of fever
Responders | 85% | 24%
Weighted difference (95% CI) | 62 (45, 78) | -
JIA ACR Response Rates at Week 12
JIA ACR 30
Responders Weighted difference a (95% CI) b | 91% 67 (51, 83) | 24% -
JIA ACR 50
Responders Weighted difference a (95% CI) b | 85% 74 (58, 90) | 11% -
JIA ACR 70
Responders Weighted difference a (95% CI) b | 71% 63 (46, 80) | 8% -
aThe weighted difference is the difference between the tocilizumab and Placebo response rates, adjusted for the stratification factors (weight, disease duration, background oral corticosteroid dose and background methotrexate use).
b CI: confidence interval of the weighted difference.

The treatment effect of tocilizumab was consistent across all components of the JIA ACR response core variables. JIA ACR scores and absence of fever responses in the open label extension were consistent with the controlled portion of the study (data available through 44 weeks).

Systemic Features

Of patients with fever or rash at baseline, those treated with tocilizumab had fewer systemic features; 35 out of 41 (85%) became fever free (no temperature recording at or above 37.5°C in the preceding 14 days) compared to 5 out of 24 (21%) of placebo-treated patients, and 14 out of 22 (64%) became free of rash compared to 2 out of 18 (11%) of placebo-treated patients. Responses were consistent in the open label extension (data available through 44 weeks).

Corticosteroid Tapering

Of the patients receiving oral corticosteroids at baseline, 8 out of 31 (26%) placebo and 48 out of 70 (69%), tocilizumab patients achieved a JIA ACR 70 response at week 6 or 8 enabling corticosteroid dose reduction. Seventeen (24%) tocilizumab patients versus 1 (3%) placebo patient were able to reduce the dose of corticosteroid by at least 20% without experiencing a subsequent JIA ACR 30 flare or occurrence of systemic symptoms to week 12. In the open label portion of the study, by week 44, there were 44 out of 103 (43%) tocilizumab patients off oral corticosteroids. Of these 44 patients 50% were off corticosteroids 18 weeks or more.

Health Related Outcomes

Physical function and disability were assessed using the Childhood Health Assessment Questionnaire Disability Index (CHAQ-DI). Seventy-seven percent (58 out of 75) of patients in the tocilizumab treatment group achieved a minimal clinically important improvement in CHAQ-DI (change from baseline of ≥ 0.13 units) at week 12 compared to 19% (7 out of 37) in the placebo treatment group.

14.8 Systemic Juvenile Idiopathic Arthritis - Subcutaneous Administration

Subcutaneously administered tocilizumab in pediatric patients with systemic juvenile idiopathic arthritis (SJIA) was assessed in WA28118 (NCT01904292), a 52-week, open-label, multicenter, PK-PD and safety study to determine the appropriate subcutaneous dose of tocilizumab that achieved comparable PK/PD profiles to the tocilizumab-IV regimen.

Eligible patients received tocilizumab subcutaneously dosed according to body weight, with patients weighing at or above 30 kg (n = 26) dosed with 162 mg of tocilizumab every week and patients weighing below 30 kg (n = 25) dosed with 162 mg of tocilizumab every 10 days (n=8) or every 2 weeks (n=17) for 52 weeks. Of these 51 patients, 26 (51%) were naïve to subcutaneous tocilizumab and 25 (49%) had been receiving tocilizumab intravenously and switched to subcutaneous tocilizumab at baseline.

The efficacy of subcutaneous tocilizumab in children 2 to 17 years of age is based on pharmacokinetic exposure and extrapolation of the established efficacy of intravenous tocilizumab in systemic JIA patients [see Clinical Pharmacology (12.3) and Clinical Studies (14.8)].

14.9 Cytokine Release Syndrome – Intravenous Administration

The efficacy of tocilizumab for the treatment of CRS was assessed in a retrospective analysis of pooled outcome data from clinical trials of CAR T-cell therapies for hematological malignancies. Evaluable patients had been treated with tocilizumab 8 mg/kg (12 mg/kg for patients < 30 kg) with or without additional high-dose corticosteroids for severe or life-threatening CRS; only the first episode of CRS was included in the analysis. The study population included 24 males and 21 females (total 45 patients) of median age 12 years (range, 3–23 years); 82% were Caucasian. The median time from start of CRS to first dose of tocilizumab was 4 days (range, 0-18 days). Resolution of CRS was defined as lack of fever and off vasopressors for at least 24 hours. Patients were considered responders if CRS resolved within 14 days of the first dose of tocilizumab, if no more than 2 doses of tocilizumab were needed, and if no drugs other than tocilizumab and corticosteroids were used for treatment. Thirty-one patients (69%; 95% CI: 53%–82%) achieved a response. Achievement of resolution of CRS within 14 days was confirmed in a second study using an independent cohort that included 15 patients (range: 9–75 years old) with CAR T cell-induced CRS.

14.10 COVID-19 – Intravenous Administration

The efficacy of tocilizumab for the treatment of COVID-19 was based on RECOVERY (NCT04381936), a randomized, controlled, open-label, platform study, and supported by the results from EMPACTA (NCT04372186), a randomized, double-blind, placebo-controlled study. Results of two other randomized, double-blind, placebo-controlled studies, COVACTA (NCT04320615) and REMDACTA (NCT04409262), which evaluated the efficacy of tocilizumab for the treatment of COVID-19 are also summarized.

RECOVERY (Randomised Evaluation of COVID-19 Therapy) Collaborative Group Study in Hospitalized Adults Diagnosed with COVID-19

RECOVERY was a randomized, controlled, open-label, multicenter platform study conducted in the United Kingdom to evaluate the efficacy and safety of potential treatments in hospitalized adult patients with severe COVID-19 pneumonia. Eligible patients for the tocilizumab portion of the study had clinically suspected or laboratory-confirmed SARS-CoV-2 infection and no medical contraindications to any of the treatments and had clinical evidence of progressive COVID-19 (defined as oxygen saturation <92% on room air or receiving oxygen therapy, and CRP ≥75 mg/L). Patients were then randomized to receive either standard of care (SoC) or intravenous tocilizumab at a weight-tiered dosing comparable to the recommended dosage [see Clinical Pharmacology (12.3)] in addition to SoC.

Efficacy analyses were performed in the intent-to-treat (ITT) population comprising 4116 adult patients who were randomized to the tocilizumab + SoC arm (n=2022) or to the SoC arm (n=2094). The mean age of participants was 64 years (range: 20 to 101), and patients were 67% male, 76% White, 11% Asian, 3% Black or African American, and 1% mixed race. At baseline, 0.2% of patients were not on supplemental oxygen, 45% of patients required low flow oxygen, 41% of patients required non-invasive ventilation or high-flow oxygen, and 14% of patients required invasive mechanical ventilation; 82% of patients were reported to be receiving systemic corticosteroids. The primary efficacy endpoint was time to death through Day 28. The results for the overall population and the subgroups of patients who were or were not receiving systemic corticosteroids at time of randomization are summarized in Table 11.

Table 11 Mortality through Day 28 in RECOVERY
 | Tocilizumab +SoC N=2022 n (%)^1 | SoC N=2094 n (%)^1 | Hazard Ratio (95% CI) | Risk Difference (95% CI)
Mortality | 621 (30.7%) | 729 (34.9%) | 0.85 (0.76, 0.94) p= 0.00281 | -4.1% (-7.0, -1.3)
By baseline receipt of corticosteroid use
Mortality for patients receiving systemic corticosteroids at randomization^2 | 482/1664 (29.0%) | 600/1721 (34.9%) | 0.79 (0.70, 0.89) | -5.9% (-9.1, -2.8)
Mortality for patients not receiving systemic corticosteroids at randomization^2 | 139/357 (39.0%) | 127/367 (34.6%) | 1.16 (0.91, 1.48) | 4.4% (-2.6, 11.5)
^1 P-value reflects that the RECOVERY trial primary analysis results were statistically significant at the two-sided significance level of 𝛼 = 0.05.
^2 Probabilities of dying by Day 28 were estimated by the Kaplan-Meier method.

EMPACTA

EMPACTA was a randomized, double-blind, placebo-controlled, multicenter study to evaluate intravenous tocilizumab 8 mg/kg in combination with SoC in hospitalized, non-ventilated adult patients with COVID-19 pneumonia. Eligible patients were at least 18 years of age, had confirmed SARS-CoV-2 infection by a positive reverse-transcriptase polymerase chain reaction (RT-PCR) result, had pneumonia confirmed by radiography, and had SpO2 < 94% on ambient air.

Of the 389 patients randomized, efficacy analyses were performed in the modified intent-to-treat (mITT) population comprising 377 patients who were randomized and received study medication (249 in the tocilizumab arm; 128 in the placebo arm). The mean age of participants was 56 years (range: 20 to 95); 59% of patients were male, 56% were of Hispanic or Latino ethnicity, 53% were White, 20% were American Indian/Alaska Native, 15% were Black/African American and 2% were Asian. At baseline, 9% patients were not on supplemental oxygen, 64% patients required low flow oxygen, 27% patients required high-flow oxygen, and 73% were on corticosteroids.

The primary efficacy endpoint evaluated time to progression to mechanical ventilation or death through Day 28. The hazard ratio comparing tocilizumab to placebo was 0.56 (95% CI, 0.33 to 0.97), a statistically significant result (log-rank, p-value = 0.036). The cumulative proportion of patients who required mechanical ventilation or died by Day 28 was 12.0% (95% CI, 8.5% to 16.9%) in the tocilizumab arm and 19.3% (95% CI, 13.3% to 27.4%) in the placebo arm.

Mortality at Day 28 was 10.4% in the tocilizumab arm versus 8.6% in the placebo arm (weighted difference (tocilizumab arm - placebo arm): 2.0% [95% CI, -5.2% to 7.8%]).

COVACTA

COVACTA was a randomized, double-blind, placebo-controlled, multicenter study to evaluate intravenous tocilizumab 8 mg/kg in combination with SoC for the treatment of adult patients hospitalized with severe COVID-19 pneumonia. The study randomized 452 patients who were at least 18 years of age with confirmed SARS-CoV2 infection by a positive RT-PCR result, had pneumonia confirmed by radiography, and had oxygen saturation of 93% or lower on ambient air or a ratio of arterial oxygen partial pressure to fractional inspired oxygen of 300 mmHg or less. At baseline, 3% of patients were not on supplemental oxygen, 28% were on low flow oxygen, 30% were on non-invasive ventilation or high flow oxygen, 38% were on invasive mechanical ventilation, and 22% were on corticosteroids. The primary efficacy endpoint was clinical status on Day 28 assessed on a 7-category ordinal scale that ranged from “discharged” to “death.” There were no statistically significant differences observed in the distributions of clinical status on the 7-category ordinal scale at Day 28 when comparing the tocilizumab arm to the placebo arm.

Mortality at Day 28 was 19.7% in the tocilizumab arm versus 19.4% in the placebo arm (weighted difference (tocilizumab arm - placebo arm): 0.3% [95% CI, -7.6 to 8.2]).

REMDACTA

REMDACTA was a randomized, double-blind, placebo-controlled, multicenter study to evaluate intravenous tocilizumab 8 mg/kg in combination with intravenous remdesivir (RDV) 200 mg on Day 1 followed by 100 mg once daily for a total of 10 days in hospitalized patients with severe COVID-19 pneumonia. The study randomized 649 adult patients with SARS-CoV-2 infection confirmed by a positive polymerase chain reaction (PCR) result, pneumonia confirmed by radiography, and who required supplemental oxygen > 6 L/min to maintain SpO2 >93%. At baseline, 7% of patients were on low flow oxygen, 80% were on non-invasive ventilation or high flow oxygen, 14% were on invasive mechanical ventilation, and 84% were on corticosteroids.

The primary efficacy endpoint was time from randomization to hospital discharge or ‘ready for discharge’ up to Day 28. There was no statistically significant difference between the treatment arms with respect to time to hospital discharge or “ready for discharge” through Day 28.

Mortality at Day 28 was 18.1% in the tocilizumab + RDV arm versus 19.5% in the placebo +RDV arm (weighted difference (tocilizumab arm - placebo arm): -1.3% [95% CI, -7.8% to 5.2%]).

Mortality Across Studies in Patients Receiving Baseline Corticosteroids

A study-level meta-analysis was conducted on EMPACTA, COVACTA, REMDACTA and RECOVERY studies. For each of the four studies, the risk difference through Day 28 was estimated by the Kaplan-Meier method in the subgroup of patients receiving baseline corticosteroids, summarized in Figure 2. Patients from the RECOVERY trial represent 78.8% of the total sample size in this meta-analysis. The combined risk difference showed that tocilizumab treatment (n=2261) resulted in a 4.61% absolute reduction in the risk of death at Day 28 (risk difference=-4.6%; 95% CI: -7.3% to -1.9%) compared to SoC (n=2034).

Figure 2 Risk Differences Through Day 28 for Baseline Corticosteroid Use Subpopulation in RECOVERY, EMPACTA, COVACTA and REMDACTA studies

16 HOW SUPPLIED/STORAGE AND HANDLING

How Supplied:

TYENNE (tocilizumab-aazg) injection is a preservative-free, sterile clear and colorless to pale yellow solution. The following packaging configurations are available:

For Intravenous Infusion

TYENNE Single-Dose Vial

Each TYENNE carton contains one vial. Each vial is supplied as 80 mg/4 mL (20 mg/mL) (NDC 65219-590-04), 200 mg/10 mL (20 mg/mL) (NDC 65219-592-10), and 400 mg/20 mL (20 mg/mL) (NDC 65219-594-20) TYENNE solution for further dilution prior to intravenous infusion. The vial stopper is not made with natural rubber latex.

For Subcutaneous Injection

TYENNE Prefilled Syringe

Each TYENNE carton contains a single-dose prefilled syringe delivering 162 mg/0.9 mL of TYENNE. The syringe plunger stopper and needle cover are not made with natural rubber latex. The NDC number is 65219-598-10.

TYENNE Autoinjector

Each TYENNE carton contains a single-dose autoinjector delivering 162 mg/0.9 mL of TYENNE. The syringe plunger stopper and needle cover are not made with natural rubber latex. The NDC number is 65219-596-01.

Storage and Handling: Do not use beyond expiration date on the container, package, prefilled syringe, or autoinjector. TYENNE must be refrigerated at 36°F to 46°F (2ºC to 8ºC). Do not freeze. A single prefilled syringe (or autoinjector) may be stored at room temperature at or below 77°F (25°C) for a single period of up to 14 days. Protect the vials, syringes and autoinjectors from light by storage in the original package until time of use, and keep syringes and autoinjectors dry. Do not shake.

17 PATIENT COUNSELING INFORMATION

Advise the patient to read the FDA-approved patient labeling (Medication Guide and Instructions for Use).

- Serious Infections

Inform patients that TYENNE may lower their resistance to infections [see Warnings and Precautions (5.1)]. Instruct the patient of the importance of contacting their doctor immediately when symptoms suggesting infection appear in order to assure rapid evaluation and appropriate treatment.

- Gastrointestinal Perforation

Inform patients that some patients who have been treated with TYENNE have had serious side effects in the stomach and intestines [see Warnings and Precautions (5.2)]. Instruct the patient of the importance of contacting their doctor immediately when symptoms of fever, severe, persistent abdominal pain, and change in bowel habits appear to assure rapid evaluation and appropriate treatment.

- Hypersensitivity and Serious Allergic Reactions

Inform patients that some patients who have been treated with TYENNE have developed serious allergic reactions, including anaphylaxis, as well as serious skin reactions [see Warnings and Precautions (5.6)]. Advise patients to stop taking TYENNE and seek immediate medical attention if they experience any symptom of serious allergic reactions (including rash, hives, and swelling of the face, lips, tongue, and throat that may cause difficulty in breathing or swallowing).

Instruction on Injection Technique

Assess patient suitability for home use for subcutaneous injection. Perform the first injection under the supervision of a qualified healthcare professional. If a patient or caregiver is to administer subcutaneous TYENNE, instruct him/her in injection techniques and assess his/her ability to inject subcutaneously to ensure proper administration of subcutaneous TYENNE and the suitability for home use [See Instructions for Use].

Prior to use, remove the prefilled syringe (PFS) or autoinjector from the refrigerator and allow to sit at room temperature outside of the carton for 30 minutes (PFS) or 45 minutes (autoinjector), out of the reach of children.

Do not warm TYENNE in any other way.

Advise patients to consult their healthcare provider if the full dose is not received.

A puncture-resistant container for disposal of needles, syringes and autoinjectors should be used and should be kept out of the reach of children. Instruct patients or caregivers in the technique as well as proper needle, syringe and autoinjector disposal, and caution against reuse of these items.

Pregnancy

Inform female patients of reproductive potential that TYENNE may cause fetal harm and to inform their prescriber of a known or suspected pregnancy [see Use in Specific Populations (8.1)].

TYENNE (tocilizumab-aazg)

Manufactured by:
Fresenius Kabi USA, LLC
Lake Zurich, IL 60047, U.S.A.

U.S. License Number: 2146

Medication Guide
TYENNE® (tye en')
(tocilizumab-aazg)
injection for intravenous use
TYENNE® (tye en')
(tocilizumab-aazg)
injection for subcutaneous use

What is the most important information I should know about TYENNE?
TYENNE can cause serious side effects including:

1. Serious Infections. TYENNE is a medicine that affects your immune system. TYENNE can lower the ability of your immune system to fight infections. Some people have serious infections while taking TYENNE, including tuberculosis (TB), and infections caused by bacteria, fungi, or viruses that can spread throughout the body. Some people have died from these infections. Your healthcare provider should assess you for TB before starting TYENNE (except if you have COVID-19).

If you have COVID-19, your healthcare provider should monitor you for signs and symptoms of new infections during and after treatment with TYENNE.

Your healthcare provider should monitor you closely for signs and symptoms of TB during and after treatment with
TYENNE

- You should not start taking TYENNE if you have any kind of infection unless your healthcare provider says it is okay.

Before starting TYENNE, tell your healthcare provider if you:

- think you have an infection or have symptoms of an infection, with or without a fever, such as:

  - sweating or chills
  - shortness of breath
  - warm, red, or painful skin or sores on your body

  - feel very tired
  - muscle aches
  - blood in phlegm
  - diarrhea or stomach pain

  - cough
  - weight loss
  - burning when you urinate more often than normal

- are being treated for an infection.
- get a lot of infections or have infections that keep coming back.
- have diabetes, HIV, or a weak immune system. People with these conditions have a higher chance for infections.
- have TB or have been in close contact with someone with TB.
- live or have lived or have traveled to certain parts of the country (such as the Ohio and Mississippi River valleys and the Southwest) where there is an increased chance for getting certain kinds of fungal infections (histoplasmosis, coccidiomycosis, or blastomycosis). These infections may happen or become more severe if you use TYENNE. Ask your healthcare provider if you do not know if you have lived in an area where these infections are common.
- have or have had hepatitis B.

After starting TYENNE, call your healthcare provider right away if you have any symptoms of an infection. TYENNE can make you more likely to get infections or make worse any infection that you have.

2. Tears (perforation) of the stomach or intestines.
  1. Tell your healthcare provider if you have had diverticulitis (inflammation in parts of the large intestine) or ulcers in your stomach or intestines. Some people taking TYENNE get tears in their stomach or intestine. This happens most often in people who also take nonsteroidal anti-inflammatory drugs (NSAIDs), corticosteroids, or methotrexate.
  2. Tell your healthcare provider right away if you have fever and stomach-area pain that does not go away, and a change in your bowel habits.
3. Liver problems (Hepatotoxicity): Some people have experienced serious life-threatening liver problems, which required a liver transplant or led to death. Your healthcare provider may tell you to stop taking TYENNE if you develop new or worse liver problems during treatment with TYENNE. Tell your healthcare provider right away if you have any of the following symptoms:

  - feeling tired (fatigue)
  - lack of appetite for several days or longer (anorexia)
  - yellowing of your skin or the whites of your eyes (jaundice)
  - abdominal swelling and pain on the right side of your stomach-area
  - light colored stools

  - Weakness
  - nausea and vomiting
  - confusion
  - dark “tea-colored” urine

4. Changes in certain laboratory test results. Your healthcare provider should do blood tests before you start receiving TYENNE. If you have rheumatoid arthritis (RA) or giant cell arteritis (GCA) your healthcare provider should do blood tests every 4 to 8 weeks after you start receiving TYENNE for the first 6 months and then every 3 months after that. If you have polyarticular juvenile idiopathic arthritis (PJIA) you will have blood tests done every 4 to 8 weeks during treatment. If you have systemic juvenile idiopathic arthritis (SJIA) you will have blood tests done every 2 to 4 weeks during treatment. These blood tests are to check for the following side effects of TYENNE:
  1. low neutrophil count. Neutrophils are white blood cells that help the body fight off bacterial infections.
  2. low platelet count. Platelets are blood cells that help with blood clotting and stop bleeding.
  3. increase in certain liver function tests.
  4. increase in blood cholesterol levels. You may also have changes in other laboratory tests, such as your blood cholesterol levels. Your healthcare provider should do blood tests to check your cholesterol levels 4 to 8 weeks after you start receiving TYENNE.

Your healthcare provider will determine how often you will have follow-up blood tests. Make sure you get all your follow-up blood tests done as ordered by your healthcare provider.
You should not receive TYENNE if your neutrophil or platelet counts are too low, or your liver function tests are too high.
Your healthcare provider may stop your TYENNE treatment for a period of time or change your dose of medicine if needed because of changes in these blood test results.

5. Cancer. TYENNE may increase your risk of certain cancers by changing the way your immune system works. Tell your healthcare provider if you have ever had any type of cancer.

See “What are the possible side effects with TYENNE?” for more information about side effects.

What is TYENNE?
TYENNE is a prescription medicine called an Interleukin-6 (IL-6) receptor antagonist. TYENNE is used:

- To treat adults with moderately to severely active rheumatoid arthritis (RA), after at least one other medicine called a Disease-Modifying Anti-Rheumatic Drug (DMARD) has been used and did not work well.
- To treat adults with giant cell arteritis (GCA).
- To treat people with active PJIA ages 2 and above.
- To treat people with active SJIA ages 2 and above.
- To treat people age 2 years and above who experience severe or life-threatening Cytokine Release Syndrome (CRS) following chimeric antigen receptor (CAR) T cell treatment.
- To treat hospitalized adults with coronavirus disease 2019 (COVID-19) receiving systemic corticosteroids and requiring supplemental oxygen or mechanical ventilation.
- TYENNE is not approved for subcutaneous use in people with CRS or COVID-19.

It is not known if TYENNE is safe and effective in children with PJIA or SJIA or CRS under 2 years of age or in children with conditions other than PJIA or SJIA or CRS.

Do not take TYENNE: if you are allergic to tocilizumab products, or any of the ingredients in TYENNE. See the end of this Medication Guide for a complete list of ingredients in TYENNE.

Before you receive TYENNE, tell your healthcare provider about all of your medical conditions, including if you:

- have an infection. See “What is the most important information I should know about TYENNE?”
- have liver problems.
- have any stomach-area (abdominal) pain or been diagnosed with diverticulitis or ulcers in your stomach or intestines.
- have had a reaction to tocilizumab or any of the ingredients in TYENNE before.
- have or had a condition that affects your nervous system, such as multiple sclerosis.
- have recently received or are scheduled to receive a vaccine:
  - All vaccines should be brought up-to-date before starting TYENNE, unless urgent treatment initiation is required.
  - People who take TYENNE should not receive live vaccines.
  - People taking TYENNE can receive non-live vaccines.
- plan to have surgery or a medical procedure.
- are pregnant or plan to become pregnant or are pregnant. TYENNE may harm your unborn baby. Tell your healthcare provider if you become pregnant or think you may be pregnant during treatment with TYENNE.
- are breastfeeding or plan to breastfeed. It is not known if TYENNE passes into your breast milk. Talk to your healthcare provider about the best way to feed your baby if you take TYENNE.

Tell your healthcare provider about all of the medicines you take, including prescription, over-the-counter medicines, vitamins, and herbal supplements. TYENNE and other medicines may affect each other causing side effects.
Especially tell your healthcare provider if you take:

- any other medicines to treat your RA. You should not take etanercept (Enbrel), adalimumab (Humira), infliximab (Remicade), rituximab (Rituxan), abatacept (Orencia), anakinra (Kineret), certolizumab (Cimzia), or golimumab (Simponi) while you are taking TYENNE. Taking TYENNE with these medicines may increase your risk of infection.
- medicines that affect the way certain liver enzymes work. Ask your healthcare provider if you are not sure if your medicine is one of these.

Know the medicines you take. Keep a list of them to show to your healthcare provider and pharmacist when you get a new medicine.

How will I receive TYENNE?
Into a vein (IV or intravenous infusion) for Rheumatoid Arthritis, Giant Cell Arteritis, PJIA, SJIA, CRS, or COVID-19:

- If your healthcare provider prescribes TYENNE as an IV infusion, you will receive TYENNE from a healthcare provider through a needle placed in a vein in your arm. The infusion will take about 1 hour to give you the full dose of medicine.
- For rheumatoid arthritis, giant cell arteritis or PJIA you will receive a dose of TYENNE about every 4 weeks.
- For SJIA you will receive a dose of TYENNE about every 2 weeks.
- For CRS you will receive a single dose of TYENNE, and if needed, additional doses.
- For COVID-19, you will receive a single dose of TYENNE, and if needed one additional dose.
- While taking TYENNE, you may continue to use other medicines that help treat your rheumatoid arthritis, PJIA, SJIA or COVID-19 such as methotrexate, non-steroidal anti-inflammatory drugs (NSAIDs) and prescription steroids, as instructed by your healthcare provider.
- Keep all of your follow-up appointments and get your blood tests as ordered by your healthcare provider.

Under the skin (SC or subcutaneous injection) for Rheumatoid Arthritis, Giant Cell Arteritis, PJIA or SJIA:

- See the Instructions for Use at the end of this Medication Guide for instructions about the right way to prepare and give your TYENNE injections at home.
- TYENNE is available as a single-dose prefilled syringe or single-dose prefilled autoinjector.
- You may also receive TYENNE as an injection under your skin (subcutaneous). If your healthcare provider decides that you or a caregiver can give your injections of TYENNE at home, you or your caregiver should receive training on the right way to prepare and inject TYENNE. Do not try to inject TYENNE until you have been shown the right way to give the injections by your healthcare provider.
- For PJIA or SJIA, you may self-inject with the prefilled syringe or prefilled autoinjector, or your caregiver can give you TYENNE, if both your healthcare provider and parent/legal guardian find it appropriate.
- Your healthcare provider will tell you how much TYENNE to use and when to use it.

What are the possible side effects with TYENNE?
TYENNE can cause serious side effects, including:

- See “What is the most important information I should know about TYENNE?”
- Hepatitis B infection in people who carry the virus in their blood. If you are a carrier of the hepatitis B virus (a virus that affects the liver), the virus may become active while you use TYENNE. Your healthcare provider may do blood tests before you start treatment with TYENNE and while you are using TYENNE. Tell your healthcare provider if you have any of the following symptoms of a possible hepatitis B infection:

  - feel very tired
  - vomiting
  - chills
  - dark urine

  - skin or eyes look yellow
  - clay-colored bowel movements
  - stomach discomfort
  - skin rash

  - little or no appetite
  - fevers
  - muscle aches

- Serious Allergic Reactions: Serious: Allergic Reactions. Serious allergic reactions, including death, can happen with TYENNE. These reactions can happen with any infusion or injection of TYENNE, even if they did not occur with an earlier infusion or injection. Stop taking TYENNE, contact your healthcare provider, and get emergency help right away if you have any of the following signs of a serious allergic reaction:
  - swelling of your face, lips, mouth, or tongue
  - trouble breathing
  - wheezing
  - severe itching
  - skin rash, hives, redness, or swelling outside of the injection site are
  - dizziness or fainting
  - fast heartbeat or pounding in your chest (tachycardia)
  - sweating
- Nervous system problems. While rare, Multiple Sclerosis has been diagnosed in people who take TYENNE. It is not known what effect TYENNE may have on some nervous system disorders.

The most common side effects of TYENNE include:

- upper respiratory tract infections (common cold, sinus infections)
- headache
- increased blood pressure (hypertension)
- injection site reactions

Tell your healthcare provider about any side effect that bothers you or does not go away. These are not all the possible side effects of TYENNE. For more information, ask your healthcare provider or pharmacist.

Call your doctor for medical advice about side effects. You may report side effects to FDA at 1-800-FDA-1088.
You may also report side effects to Fresenius Kabi USA, LLC at 1-800-551-7176.
General information about the safe and effective use of TYENNE.
Medicines are sometimes prescribed for purposes other than those listed in a Medication Guide. Do not give TYENNE to other people, even if they have the same symptoms that you have. It may harm them. You can ask your pharmacist or healthcare provider for information about TYENNE that is written for health professionals.
For more information go to www.TYENNE.com or you can enroll in a patient support program by calling 1-833-522-4227 or visiting the patient support program website: www.kabicare.com.

What are the ingredients in TYENNE?
Active ingredient: tocilizumab-aazg.
Inactive ingredients of Intravenous and Subcutaneous TYENNE: arginine, histidine, hydrochloric acid, lactic acid, polysorbate 80, sodium chloride, sodium hydroxide and Water for Injection.
TYENNE is a registered trademark of Fresenius Kabi
Manufactured by: Fresenius Kabi USA LLC, Lake Zurich, IL 60047, U.S.A
U.S License Number 2146

This Medication Guide has been approved by the U.S. Food and Drug Administration Revised: 02/2025

INSTRUCTIONS FOR USE

Read and follow the Instructions for Use that come with your TYENNE autoinjector before you start using it and each time you get a refill. There may be new information. This information does not replace talking to your healthcare provider about your medical condition or treatment.

If you have any questions about using your TYENNE autoinjector, please call your healthcare provider or Company at 1-833-522-4227.

Important information

- Read the Medication Guide that comes with your autoinjector for important information you need to know before using it.
- Before you use the autoinjector for the first time, make sure your healthcare provider shows you the right way to use it.
- Do not try to take apart the TYENNE autoinjector at any time.
- Always inject TYENNE the way your healthcare provider taught you to.

Using the TYENNE autoinjector

- The autoinjector is for self-injection or administration with the help of a caregiver.
- The autoinjector is for use at home.
- When injecting TYENNE, children may self-inject if both the healthcare provider and caregiver find it appropriate.
- Do not reuse the autoinjector. The autoinjector is for single-dose (1-time) use only.
- Do not share your autoinjector with another person. You may give another person an infection or get an infection from them.
- Do not remove the autoinjector clear cap until you are ready to inject.
- Do not use the autoinjector if it shows any signs of damage or if it has been dropped.

Storing TYENNE autoinjectors

- Store TYENNE in the refrigerator between 36°F to 46°F (2°C to 8°C).
- Store unused autoinjectors in the original carton to protect from light.
- Do not freeze TYENNE. Do not use TYENNE if frozen. Throw away (dispose of) in a sharps disposal container.
- Do not expose TYENNE to heat or direct sunlight.
- Keep the autoinjector out of the reach of children.
- TYENNE may be stored at room temperature at or below 77°F (25°C) in the original carton for up to 14 days. Throw away (dispose of) TYENNE in a sharp disposal container if it has been out of the refrigerator more than 14 days. After being stored at room temperature, do not place it back in the refrigerator.
  See the Medication Guide for more information.

Traveling with TYENNE autoinjector

- When travelling on an airplane, always check with your airline and your healthcare provider about bringing injectable medicine with you. Always carry TYENNE in your carry-on luggage because the airplane luggage area can be very cold and TYENNE could freeze.

Your TYENNE autoinjector

Before Use

After Use

1.1. Prepare a clean, flat surface, such as a table or countertop, in a well-lit area.

1.2. Gather the following supplies (not included) (see Figure A):

- A sterile cotton ball or gauze
- An alcohol pad
- An FDA-cleared sharps disposal container (see Step 8, “Throw away your autoinjector”).

1.3. Remove the carton containing the autoinjector from the refrigerator.

1.4. Check the expiration date on the carton to make sure the date has not passed (see Figure B). Do not use the autoinjector if the expiration date has passed.
1.5. Check to make sure that the carton is properly sealed and is not damaged. Do not use the Autoinjector if the carton looks like it has already been opened or damaged.

1.6. Remove the tray from the carton.

1.7. Let the tray with the autoinjector sit on the prepared surface for 45 minutes before use to allow the medicine in the autoinjector to reach room temperature (see Figure C).

Note: Not doing so could cause your injection to feel uncomfortable and it could take longer to inject.
Do not warm in any other way, such as in a microwave, hot water, or direct sunlight.

1.8. Turn the tray upside down to remove the single-dose autoinjector (see Figure D).

Do not remove the clear cap of the autoinjector until you are ready to inject to avoid injury.

2.1 Check the autoinjector to make sure it is not cracked or damaged (see Figure E).

Do not use if the autoinjector shows signs of damage or if it has been dropped.

2.2 Check the autoinjector label to make sure that:

- The name on the autoinjector says TYENNE
- The expiration date (EXP) on the autoinjector has not passed (see Figure F)

Do not use the autoinjector if the name on the label is not TYENNE or the expiration date on the label has passed.

2.3 Look at the medicine in the viewing window.
Make sure it is clear and colorless to pale yellow and does not contain flakes or particles (see Figure G).

Note: Air bubbles in the medicine are normal.

Do not inject if the liquid is cloudy, discolored, or has lumps or particles in it because it may not be safe to use.

3.1 Wash your hands well with soap and water, then dry them with a clean towel (see Figure H).

4.1 If you are giving yourself the injection, you can use:

- The front of your upper thigh
- The belly (abdomen), except within 2 in (5 cm) around the belly button (navel)

If a caregiver is giving the injection, they can use the outer area of the upper arm (see Figure I).

Note: Choose a different site for each injection to reduce redness, irritation, or other skin problems.

Do not inject into skin that is sore (tender), bruised, red, hard, scaly, or has lesions, moles, scars, or stretch marks or tattoos.
Do not use the autoinjector through clothing.

5.1 Wipe the skin where you want to inject with an alcohol pad to clean it (see Figure J). Let the skin dry.
Do not blow on or touch the site after cleaning.

6.1 When you are ready to inject, hold the autoinjector in one hand with the clear cap on top, pointing straight up.
Using your other hand, firmly pull the clear cap straight off without twisting (see Figure K).

Note: Use the autoinjector within 3 minutes after removing the cap to avoid contamination.

Do not try to recap the needle at any time, even at the end of the injection.

Do not touch the needle cover (the orange part located at the tip of the autoinjector) because this might cause an accidental needle stick.

6.2 Throw away the clear cap in a sharps disposal container.

6.3 Rotate the autoinjector so that the orange needle cover points downwards.

6.4 Position your hand on the autoinjector so that you can see the window.

6.5 Place the needle cover flat against your skin at a 90-degree angle (see Figure L).
Note: To make sure you inject under the skin (into fatty tissue), do not hold the autoinjector at an angle.

Do not pinch your skin.

To make sure you inject the full dose, read all of the steps from 6.6 to 6.9 before you start:

6.6 In a single motion, push and hold the autoinjector firmly against your skin until you hear a first click. This means the injection has started (see Figure M).
The orange plunger rod will move through the window during the injection.

6.7 Hold the autoinjector in place until you hear a second click. This may take up to 10 seconds. (see Figure N).
6.8 Wait and slowly count to 5 after you hear the second click. Continue to hold the autoinjector in place to make sure you inject a full dose (see Figure O). Do not lift the autoinjector until you are sure 5 seconds has passed, and the injection is complete.

6.9 While holding the autoinjector in place, check the window to make sure the orange plunger rod has fully appeared in the viewing window, and has stopped moving (see Figure P).

7.1 When the injection is complete, lift the autoinjector straight away from your skin (see Figure Q).

Note: The needle cover will slide down and cover the needle.

Do not recap the autoinjector.

7.2 Check the window to make sure the orange plunger rod came all the way down (see Figure R).

Note: If the orange plunger rod did not come all the way down or you believe you did not get a full injection, call your healthcare provider.
Do not try to repeat the injection with a new autoinjector.

7.3 If you see blood on the injection site, press gauze or a cotton ball against on the skin until the bleeding stops (see Figure S).

Do not rub the injection site.

8.1 Put your used autoinjector in an FDA-cleared sharps disposal container right away after use (see Figure T).

Do not throw away (dispose of) your autoinjector in your household trash.
If you do not have a FDA-cleared sharps disposal container, you can use a household container that is:

- made of a heavy-duty plastic,
- can be closed with a tight-fitting, puncture-resistant lid, without sharps being able to come out,
- upright and stable during use,
- leak-resistant, and
- properly labeled to warn of hazardous waste inside the container.

When your sharps disposal container is almost full, you will need to follow your community guidelines for the right way to dispose of your sharps disposal container. There may be state or local laws about how you should throw away used needles and syringes.

For more information about safe sharps disposal, and for specific information about sharps disposal in the state that you live in, go to the FDA's website at http://www.fda.gov/safesharpsdisposal

Do not throw away (dispose of) your used sharps disposal container in your household trash unless your community guidelines permit this.

Do not recycle your used sharps disposal container.

Always keep the sharps disposal container out of reach of children.

9.1 Write the date, time, and specific part of your body where you injected yourself (see Figure U).
It may also be helpful to write any questions or concerns about the injection, so you can ask your healthcare provider.

Manufactured by:
Fresenius Kabi USA, LLC
Lake Zurich, Illinois 60047
U.S. License No. 2146

This Instructions for Use has been approved by the U.S. Food and Drug Administration Revised: 02/2025

Read and follow the Instructions for Use that come with your TYENNE prefilled syringe before you start using it and each time you get a refill. There may be new information. This does not replace talking to your healthcare provider about your medical condition or treatment.

If you have any questions about using your TYENNE prefilled syringe, please call your healthcare provider or Company at 1-833-522-4227.

Important Information

- Read the Medication Guide that comes with your TYENNE prefilled syringe for important information you need to know before using it.
- Before you use the prefilled syringe for the first time, make sure your healthcare provider shows you the right way to use it.
- Do not remove the needle cap until you are ready to inject TYENNE.
- Do not try to take apart the prefilled syringe at any time.
- Always inject TYENNE the way your healthcare provider taught you.

Using TYENNE prefilled syringe

- The prefilled syringe is for self-injection or administration with the help of a caregiver.
- Do not use the prefilled syringe if the carton is open or damaged.
- Do not use the prefilled syringe if it has been dropped on a hard surface.
  The prefilled syringe may be broken even if you cannot see the break.

Storing TYENNE prefilled syringes

- Store TYENNE in the refrigerator between 36°F to 46°F (2°C to 8°C).
- Store unused prefilled syringes in the original carton to protect from light.
- Keep the prefilled syringes out of the reach of children.
- Do not freeze TYENNE. Do not use TYENNE if frozen. Throw away (dispose of) in a sharps disposal container.
- Do not expose TYENNE to heat or direct sunlight.
- If needed, for example when traveling, TYENNE may be stored at room temperature at or below 77°F (25°C) in the original carton for up to 14 days. Throw away (dispose of) TYENNE in a sharps disposal container if it has been out of the refrigerator for more than 14 days. After being stored at room temperature, do not place it back in the refrigerator.

See the Medication Guide for more information.

Your TYENNE prefilled syringe (see Figure A)

Do not try to activate the clear needle guard before injecting.

Do not insert your fingers into the opening of the clear needle guard because the needle could injure you.

1.1 Find a comfortable space with a clean, flat working surface.

1.2 Supplies needed for your TYENNE prefilled syringe injection (see Figure B):

- TYENNE prefilled syringe
- An alcohol pad
- A sterile cotton ball or gauze
- Puncture-resistant container or sharps container for safe disposal of used syringe (see Step 7 “Throw away used prefilled syringe”)

1.3 Take the box containing the syringe out of the refrigerator and open the box (see Figure C).

1.4 Remove the plastic tray out of the box and let it warm up for 30 minutes to reach room temperature (see Figure D). If the syringe does not reach room temperature, this could cause your injection to feel uncomfortable and make it difficult to push the plunger in.

- Do not speed up the warming process in any way, such as in a microwave or placing the syringe in hot water.
- Prepare and check your records of previous injection sites. This will help you choose the appropriate injection site for this injection (see Step 8 “Record your injection”).

Remove TYENNE prefilled syringe from the plastic tray

- Place two fingers on either side, in the middle of the clear needle guard.
- Pull the prefilled syringe straight up and out of the tray (see Figure E).
- Do not pick up the prefilled syringe by the plunger or the needle cap. Doing so could damage the prefilled syringe or activate the clear needle guard.

2.1 Check the expiration date on the TYENNE prefilled syringe (see Figure F).

Do not use it if the expiration date has passed because it may not be safe to use. If the expiration date has passed, safely dispose of the syringe in a sharps container and get a new one.

2.2 Check the name on the prefilled syringe says TYENNE (see Figure F).

2.3 Check the liquid in the TYENNE prefilled syringe. It should be clear and colorless to pale yellow (see Figure G).

Do not inject TYENNE if the liquid is cloudy, discolored or has lumps or particles in it because it may not be safe to use. Safely dispose of the syringe in a sharps container and get a new one.

2.4 Check the prefilled syringe to make sure that:

- The prefilled syringe, the clear needle guard, and the needle cap are not cracked or damaged (see Figure H).
- The needle cap is securely attached (see Figure I).
- The needle guard spring is not extended (see Figure J).
- Do not use the syringe if it shows any sign of damage. If damaged, call your healthcare provider or pharmacist right away and throw away the syringe in your sharps disposal container (see Step 7 “Throw away used prefilled syringe”).

Wash your hands well with soap and water (see Figure K).

4.1 Choose an injection site

- The front of the thighs and your belly (abdomen) except for 2-inch area around your navel are the recommended injection sites (see Figure L).
- The outer area of the upper arms may also be used only if the injection is being given by a caregiver. Do not attempt to use the upper arm area by yourself (see Figure M).

4.2 Rotate injection site

- Choose a different injection site for each new injection.
- Do not inject into moles, scars, bruises, or areas where the skin is tender, red, hard or not intact.

5.1 Clean the injection site

- Wipe the injection site with an alcohol pad in a circular motion and let it air dry to reduce the chance of getting an infection. Do not touch the injection site again before giving the injection.
- Do not fan or blow on the clean area.

6.1 Remove the needle cap.

Hold the TYENNE prefilled syringe by the clear needle guard with 1 hand and pull the needle cap straight off with your other hand (see Figure N).
3. Do not hold the plunger while you remove the needle cap. If you cannot remove the needle cap, you should ask a caregiver for help or contact your healthcare provider.
4. Throw away the needle cap in your sharps container.
5. There may be a small air bubble in the TYENNE prefilled syringe. You do not need to remove it.
6. You may see drops of liquid at the end of the needle. This is normal and will not affect your dose.
7. Do not touch the needle or let it touch any surfaces.
8. Do not use the prefilled syringe if it is dropped.
9. If it is not used within 5 minutes of needle cap removal, the syringe should be disposed of in the puncture resistant container or sharps container and a new syringe should be used.
10. Never reattach the needle cap after removal.

6.2 Pinch the skin

- Hold the TYENNE prefilled syringe in 1 hand between the thumb and index finger (see Figure O).
- Do not pull back on the plunger of the syringe.
- Use your other hand and gently pinch the area of skin firmly (see Figure P). Pinching the skin is important to make sure that you inject under the skin (into fatty tissue) but not any deeper (into muscle). Injection into muscle could cause the injection to feel uncomfortable.

6.3 Insert the needle

- Use a quick, dart-like motion to insert the needle all the way into the pinched skin at an angle between 45° to 90° (see Figure Q). It is important to use the correct angle to make sure the medicine is delivered under the skin (into fatty tissue), or the injection could be painful, and the medicine may not work.
- Keep the syringe in position.
- Do not hold or push on the plunger while inserting the needle into the skin.

6.4 Inject

- Slowly inject all of the medicine by gently pushing the plunger all the way down (see Figure R).
- You must press the plunger all the way down to get the full dose of medicine until you cannot press any more (see Figure S).
- Do not pull the needle out of the skin when the plunger is pushed all the way down.

6.5 Finish Injection

- After the plunger is pushed all the way down, hold the syringe firmly without moving it, at the same angle as inserted.
- Slowly release your thumb off the plunger. The plunger will move up. The safety system will remove the needle from the skin and cover the needle (see Figure T).
- Release the pinched skin

Important: Call your healthcare provider right away if you did not inject the full dose. Injecting an incorrect amount of medicine could affect your treatment.

Do not reuse a syringe even if all of the medicine was not injected.

Do not try to recap the needle as it could lead to needle stick injury.

6.6 After the injection

- There may be a little bleeding at the injection site. You can press a cotton ball or gauze on the injection site.
- Do not rub the injection site.
- If needed, you may cover the injection site with a small bandage.

- The TYENNE prefilled syringe should not be reused.
- Do not put the needle cap back on the needle
- If your injection is given by another person, this person must also be careful when removing the syringe and disposing of the syringe to prevent accidental needle stick injury and passing injection.

How do I throw away used syringes?

Put your used syringe in an FDA-cleared sharps disposal container right away after use (see Figure U). Do not throw away (dispose of) loose needles and syringes in your household trash.

- If you do not have an FDA-cleared sharps disposal container, you may use a household container that is:
  - made of a heavy-duty plastic,
  - can be closed with a tight-fitting, puncture-resistant lid, without sharps being able to come out,
  - upright and stable during use,
  - leak-resistant and
  - properly labeled to warn of hazardous waste inside the container.
    - When your sharps disposal container is almost full, you will need to follow your community guidelines for the right way to dispose of your sharps disposal container. There may be state or local laws about how you should throw away used syringes. For more information about safe sharps disposal, and for specific information about sharps disposal in the state you live in, go to the FDA's website at: http://www.fda.gov/safesharpsdisposal
    - Do not throw away (dispose of) your used sharps disposal container in your household trash unless your community guidelines permit this. Do not recycle your used sharps disposal container.

Keep TYENNE prefilled syringes and disposal container out of the reach of children.

Write the date, time, and specific part of your body where you injected yourself (see Figure V).

It may also be helpful to write any questions or concerns about the injection, so you can ask your healthcare provider.

Manufactured by:
Fresenius Kabi USA, LLC
Lake Zurich, Illinois 60047

U.S. License No. 2146

This Instructions for Use has been approved by the U.S. Food and Drug Administration Revised: 02/2025

Principal Display Panel – 0.9 mL Prefilled syringe – Primary Label

NDC 65219-598-10 Rx only

Tyenne®
(tocilizumab-aazg)
Injection

162 mg / 0.9 mL

For Subcutaneous
Use Only

Fresenius Kabi USA, LLC

Principal Display Panel – 0.9 mL Prefilled syringe - Carton

NDC 65219-598-10 Rx only

Tyenne®
tocilizumab-aazg

Injection

162 mg / 0.9 mL

For Subcutaneous Use Only

1 single-dose prefilled syringe 0.9 mL

Carton contains:
1 single-dose prefilled syringe - Discard Unused Portion
1 Prescribing Information
1 Medication Guide
1 Instruction for Use

Dispense the enclosed
Medication Guide to each patient

Sterile Solution - No Preservative

Refrigerate Immediately

Principal Display Panel – 0.9 mL Autoinjector – Primary Label

NDC 65219-596-01 Rx only

Tyenne®
(tocilizumab-aazg)
Injection

162 mg / 0.9 mL

For Subcutaneous Use Only

Fresenius Kabi USA, LLC

Principal Display Panel – 0.9 mL Autoinjector - Carton

NDC 65219-596-01 Rx only

Tyenne®
tocilizumab-aazg

Injection

162 mg / 0.9 mL

For Subcutaneous Use Only

1 single-dose autoinjector 0.9 mL

Carton contains:
1 single-dose autoinjector - Discard Unused Portion
1 Prescribing Information
1 Medication Guide
1 Instruction for Use

Dispense the enclosed Medication Guide to each patient

Refrigerate Immediately
Sterile Solution - No Preservative